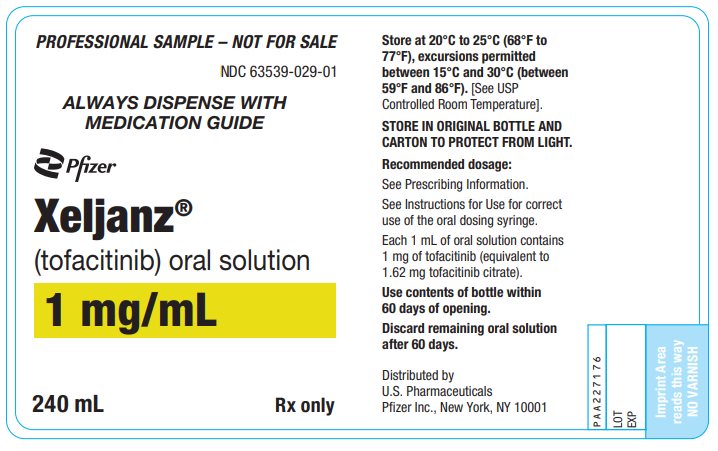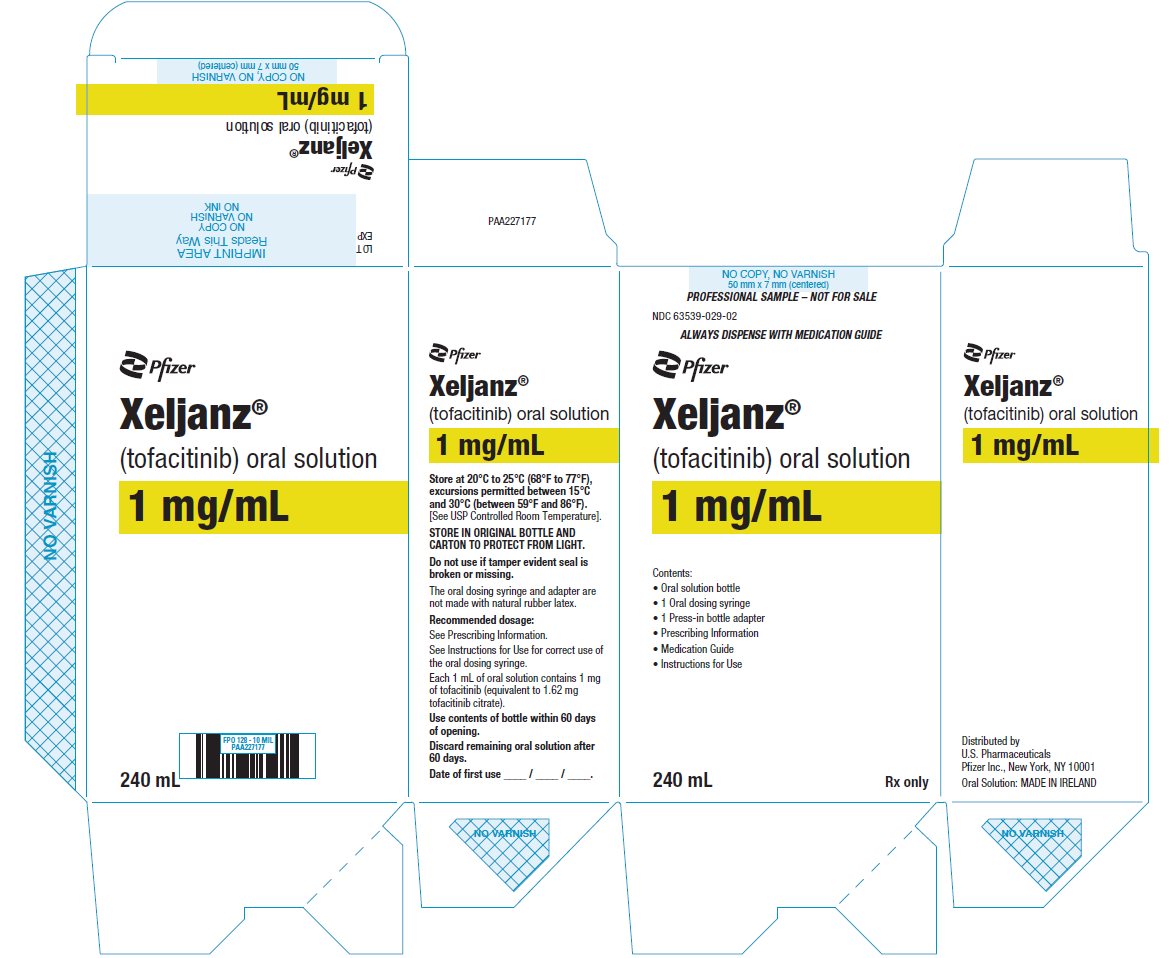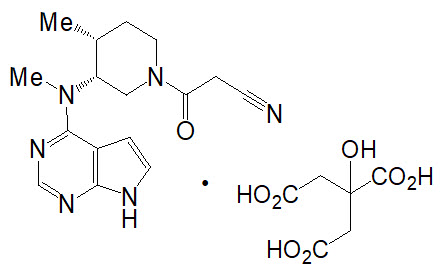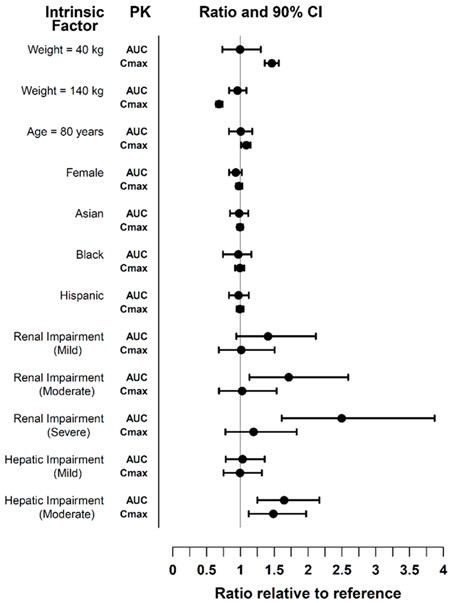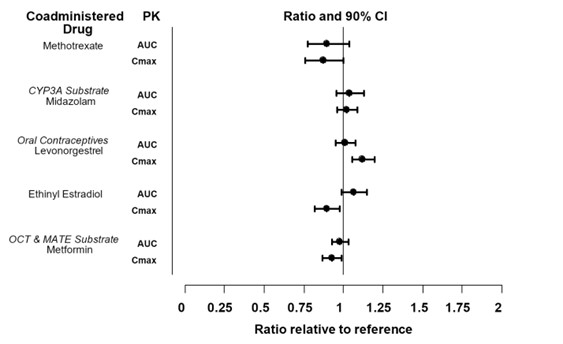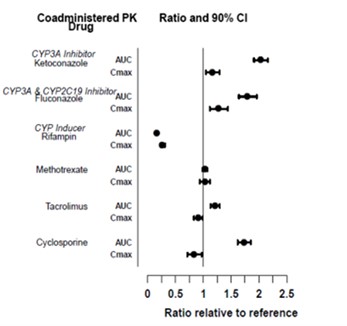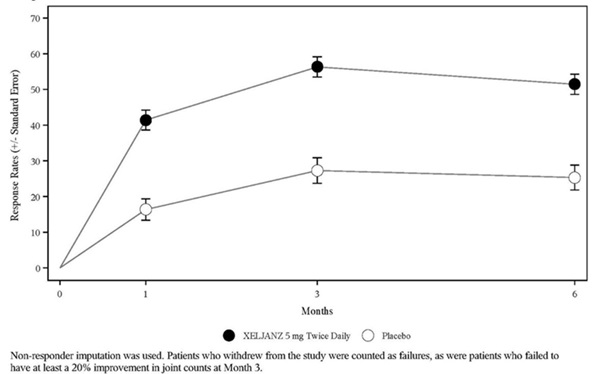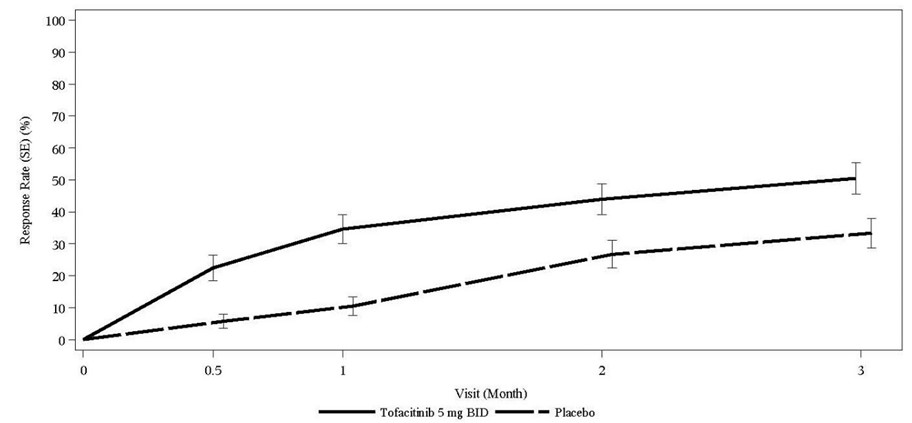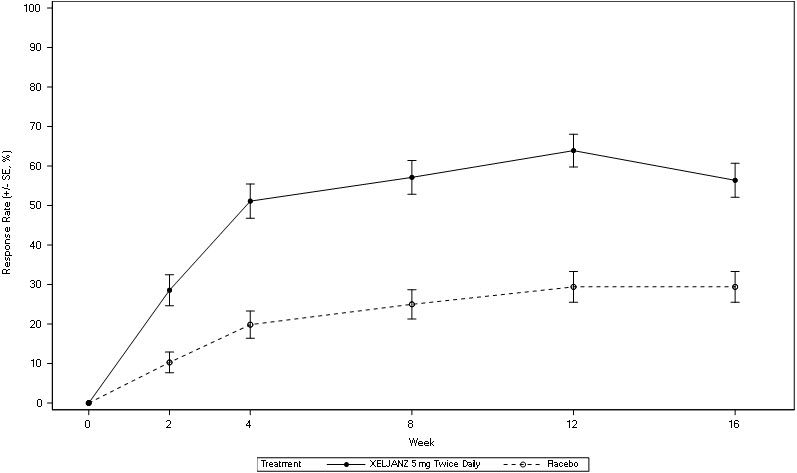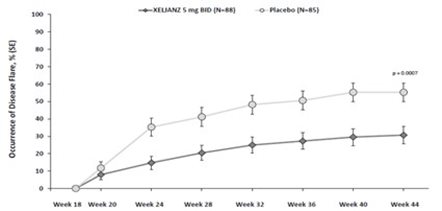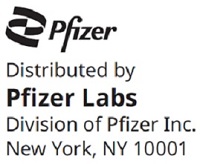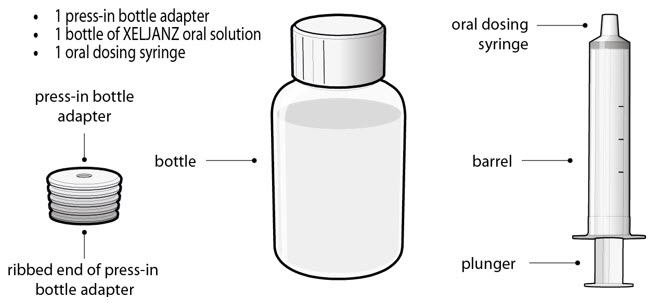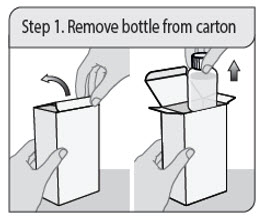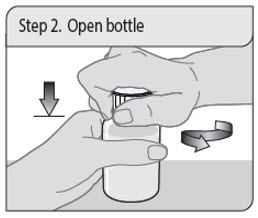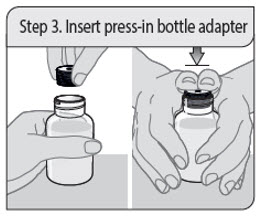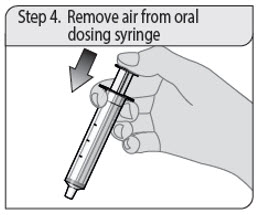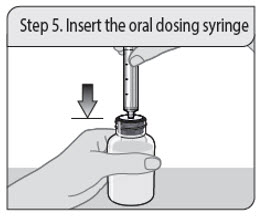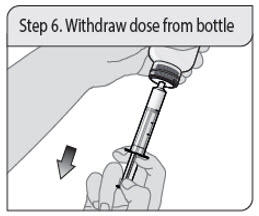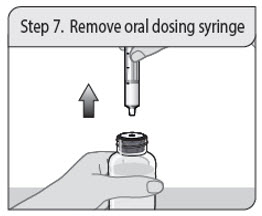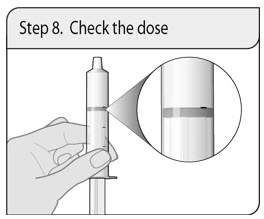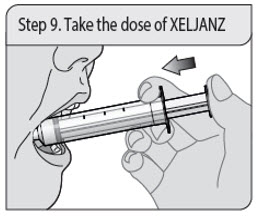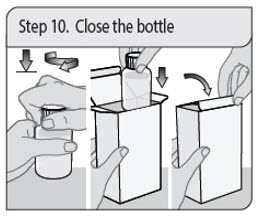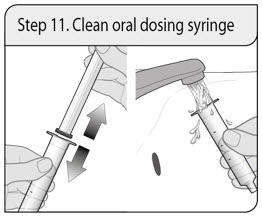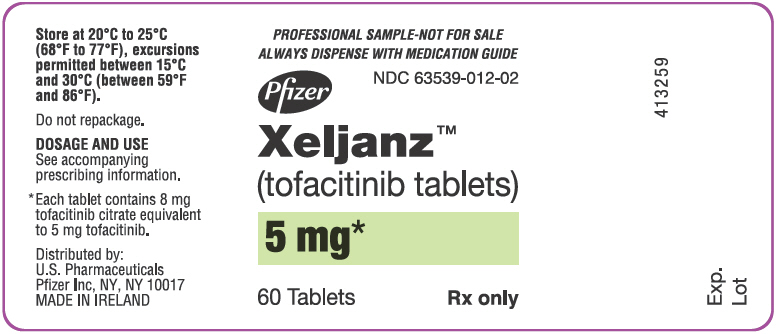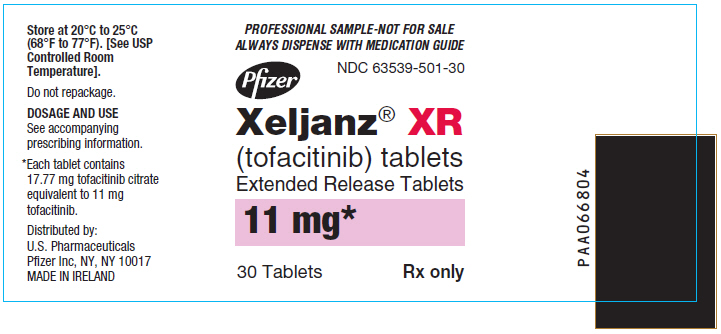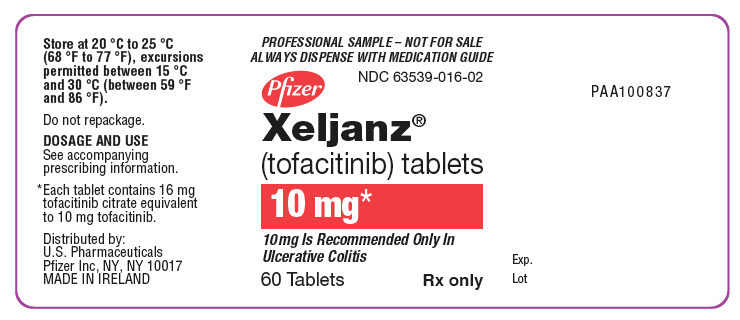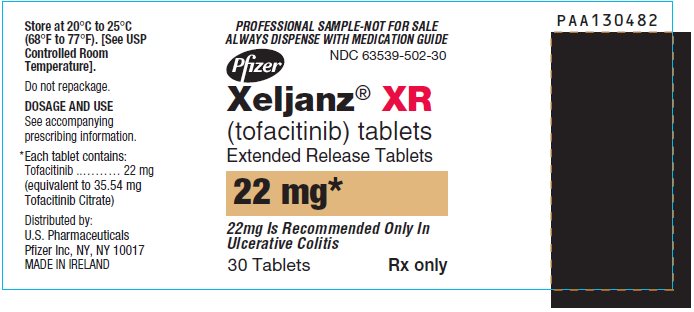 DRUG LABEL: XELJANZ
NDC: 63539-012 | Form: TABLET, FILM COATED
Manufacturer: U.S. Pharmaceuticals
Category: prescription | Type: HUMAN PRESCRIPTION DRUG LABEL
Date: 20260130

ACTIVE INGREDIENTS: TOFACITINIB CITRATE 5 mg/1 1
INACTIVE INGREDIENTS: MICROCRYSTALLINE CELLULOSE; LACTOSE MONOHYDRATE; CROSCARMELLOSE SODIUM; MAGNESIUM STEARATE; TITANIUM DIOXIDE; TRIACETIN; POLYETHYLENE GLYCOL 3350; HYPROMELLOSE 2910 (6 MPA.S)

HIGHLIGHTS OF PRESCRIBING INFORMATION

These highlights do not include all the information needed to use XELJANZ/XELJANZ XR safely and effectively. See full prescribing information for XELJANZ/XELJANZ XR.
XELJANZ® (tofacitinib) tablets, for oral use
XELJANZ® (tofacitinib) oral solution
XELJANZ® XR (tofacitinib) extended-release tablets, for oral use
Initial U.S. Approval: 2012

RECENT MAJOR CHANGES

Boxed Warning | 10/2025
Indications and Usage, Psoriatic Arthritis (1.2) | 10/2025
Dosage and Administration, Recommended Dosage in Pediatric Patients 2 Years of Age and Older with Psoriatic Arthritis or Polyarticular Course Juvenile Idiopathic Arthritis (2.4) | 10/2025

WARNING: SERIOUS INFECTIONS, MORTALITY, MALIGNANCY, MAJOR ADVERSE CARDIOVASCULAR EVENTS, and THROMBOSIS

See full prescribing information for complete boxed warning.

- Increased risk of serious bacterial, fungal, viral, and opportunistic infections, including tuberculosis (TB), leading to hospitalization or death. Interrupt XELJANZ/XELJANZ XR treatment if serious infection occurs until the infection is controlled. Test for latent TB before and during therapy; treat latent TB prior to use. Monitor all patients for active TB during treatment, even patients with initial negative latent TB test. (5.1)
- Higher rate of all-cause mortality, including sudden cardiovascular (CV) death with XELJANZ vs. TNF blockers in rheumatoid arthritis (RA) patients. (5.2)
- Malignancies have occurred in patients treated with XELJANZ. Higher rate of lymphomas and lung cancers with XELJANZ vs. TNF blockers in RA patients. (5.3)
- Higher rate of major adverse CV events (defined as CV death, myocardial infarction, and stroke) with XELJANZ vs. TNF blockers in RA patients. (5.4)
- Thrombosis has occurred in patients treated with XELJANZ. Increased incidence of pulmonary embolism, venous and arterial thrombosis with XELJANZ vs. TNF blockers in RA patients. (5.5)

1 INDICATIONS AND USAGE

XELJANZ (tablets and oral solution) and XELJANZ XR (extended-release tablets) are Janus kinase (JAK) inhibitors.

XELJANZ tablets and XELJANZ XR are indicated for the treatment of adult patients with:

- Moderately to severely active rheumatoid arthritis (RA), who have had an inadequate response or intolerance to one or more TNF blockers.
- Active psoriatic arthritis (PsA), who have had an inadequate response or intolerance to one or more TNF blockers.
- Active ankylosing spondylitis (AS), who have had an inadequate response or intolerance to one or more TNF blockers.
- Moderately to severely active ulcerative colitis (UC), who have had an inadequate response or intolerance to one or more TNF blockers.

XELJANZ (tablets and oral solution) are indicated for the treatment of pediatric patients 2 years of age and older with:

- Active PsA, who have had an inadequate response or intolerance to one or more TNF blockers.
- Active polyarticular course juvenile idiopathic arthritis (pcJIA), who have had an inadequate response or intolerance to one or more TNF blockers.

Limitations of Use:

- Use of XELJANZ/XELJANZ XR for RA, AS, PsA, or pcJIA in combination with biologic DMARDs or potent immunosuppressants such as azathioprine and cyclosporine is not recommended. (1.1, 1.2, 1.3, 1.4)
- Use of XELJANZ tablets and XELJANZ XR for UC in combination with biological therapies for UC or with potent immunosuppressants such as azathioprine and cyclosporine is not recommended. (1.5)

2 DOSAGE AND ADMINISTRATION

Recommended Evaluations and Immunization Prior to Treatment Initiation

- Prior to initiating XELJANZ/XELJANZ XR, consider performing an active and latent TB evaluation, viral hepatitis screening, a complete blood count, and updating immunizations. Avoid XELJANZ or XELJANZ XR initiation if absolute lymphocyte count <500 cells/mm^3, an absolute neutrophil count (ANC) <1000 cells/mm^3 or hemoglobin <9 g/dL. (2.1)

Important Administration Instructions

- XELJANZ XR (extended-release tablets) is not substitutable with XELJANZ (tablets and oral solution). (2.2)
- Switching between XELJANZ and XELJANZ XR should be made by the healthcare provider. (2.2)

Recommended Dosage

Adult Patients with RA, PsA or AS

- XELJANZ tablets 5 mg twice daily or XELJANZ XR (extended-release tablets) 11 mg once daily. (2.3)

Pediatric Patients 2 Years of Age and Older with PsA or pcJIA Who Weigh At Least 10 kg

- XELJANZ (tablets or oral solution) 5 mg twice daily for those ≥40 kg or weight-based equivalent twice daily for those <40 kg. (2.4)

Adult Patients with UC

- Induction: XELJANZ tablets 10 mg twice daily or XELJANZ XR 22 mg once daily for 8 weeks; evaluate patients and transition to maintenance therapy depending on therapeutic response. If needed, continue XELJANZ tablets 10 mg twice daily or XELJANZ XR 22 mg once daily for a maximum of 16 weeks. Discontinue XELJANZ tablets 10 mg twice daily or XELJANZ XR 22 mg once daily after 16 weeks if adequate therapeutic response is not achieved. (2.5)
- Maintenance: XELJANZ tablets 5 mg twice daily or XELJANZ XR 11 mg once daily. For patients with loss of response during maintenance treatment, XELJANZ tablets 10 mg twice daily or XELJANZ XR 22 mg once daily may be considered and limited to the shortest duration, with careful consideration of the benefits and risks for the individual patient. Use the lowest effective dose needed to maintain response. (2.5)

Dosage in Patients with Renal Impairment or Hepatic Impairment

- Use of XELJANZ (tablets and oral solution) or XELJANZ XR in patients with severe HI is not recommended. (2.3, 2.4, 2.5, 8.7)
- See full prescribing information (FPI) for recommended dosage in patients with moderate or severe RI or moderate HI. (2.3, 2.4, 2.5, 8.6, 8.7)

Dosage Modification

See the full prescribing information for dosage modification by indication for patients who concomitantly use CYP2C19 and/or CYP3A4 inhibitors and patients with lymphopenia, neutropenia, or anemia. (2.3, 2.4, 2.5, 7)

3 DOSAGE FORMS AND STRENGTHS

- XELJANZ tablets: 5 mg, 10 mg (3)
- XELJANZ XR extended-release tablets: 11 mg, 22 mg (3)
- XELJANZ oral solution: 1 mg/mL (3)

4 CONTRAINDICATIONS

None. (4)

5 WARNINGS AND PRECAUTIONS

- Serious Infections: Avoid use of XELJANZ (tablets and oral solution) and XELJANZ XR (extended-release tablets) during an active serious infection, including localized infections. (5.1)
- Gastrointestinal Perforations: Promptly evaluate patients at increased risk for gastrointestinal perforation who present with new onset abdominal symptoms. (5.6)
- Laboratory Monitoring: Recommended due to potential changes in lymphocytes, neutrophils, hemoglobin, liver enzymes and lipids. (5.8)
- Vaccinations: Avoid use of live vaccines concurrently with XELJANZ or XELJANZ XR. (5.9)

6 ADVERSE REACTIONS

Most common adverse reactions are:

- RA, PsA, and AS: Reported in ≥2% of adult patients treated with XELJANZ tablets monotherapy or in combination with DMARDs: upper respiratory tract infection (URI), nasopharyngitis, diarrhea, and headache. (6.1)
- PcJIA: Consistent with common adverse reactions reported in adult patients with RA. (6.1)
- UC: Reported in ≥ 5% of adult patients treated with either XELJANZ tablets and ≥1% greater than reported in patients treated with placebo: nasopharyngitis, elevated cholesterol levels, headache, URI, increased blood creatine phosphokinase, rash, diarrhea, and herpes zoster. (6.1)

To report SUSPECTED ADVERSE REACTIONS, contact Pfizer, Inc. at 1-800-438-1985 or FDA at 1-800-FDA-1088 or www.fda.gov/medwatch.

7 DRUG INTERACTIONS

See FPI for clinically significant drug interactions. (2, 7)

8 USE IN SPECIFIC POPULATIONS

Lactation: Advise not to breastfeed. (8.2)

FULL PRESCRIBING INFORMATION

WARNING: SERIOUS INFECTIONS, MORTALITY, MALIGNANCY, MAJOR ADVERSE CARDIOVASCULAR EVENTS, and THROMBOSIS

SERIOUS INFECTIONS

Patients treated with XELJANZ (tablets and oral solution) or XELJANZ XR (extended-release tablets) are at increased risk for developing serious bacterial, fungal, viral, and opportunistic infections, including tuberculosis (TB), that may lead to hospitalization or death [see Warnings and Precautions (5.1) and Adverse Reactions (6.1)]. Most patients who developed these infections were taking concomitant immunosuppressants such as methotrexate or corticosteroids. Reported infections included:

- Active TB, which may present with pulmonary or extrapulmonary disease. Patients should be tested for latent TB before XELJANZ/XELJANZ XR use and during therapy. Treatment for latent infection should be initiated prior to XELJANZ/XELJANZ XR use.
- Invasive fungal infections, including cryptococcosis and pneumocystosis. Patients with invasive fungal infections may present with disseminated, rather than localized, disease.
- Bacterial, viral, including herpes zoster, and other infections due to opportunistic pathogens.

The risks and benefits of XELJANZ/XELJANZ XR treatment should be carefully considered prior to initiating therapy in patients with chronic or recurrent infection.

Patients should be closely monitored for the development of signs and symptoms of infection during and after XELJANZ/XELJANZ XR treatment, including the possible development of TB in patients who tested negative for latent TB infection prior to initiating therapy. If a serious infection develops, interrupt XELJANZ/XELJANZ XR until the infection is controlled [see Warnings and Precautions (5.1)].

MORTALITY

In a large, randomized, postmarketing safety study in rheumatoid arthritis (RA) patients 50 years of age and older with at least one cardiovascular (CV) risk factor comparing XELJANZ tablets 5 mg or 10 mg twice a day to tumor necrosis factor (TNF) blockers, a higher rate of all-cause mortality, including sudden CV death, was observed with XELJANZ tablets 5 mg or 10 mg twice a day [see Warnings and Precautions (5.2)]. XELJANZ 10 mg twice daily and XELJANZ XR 22 mg once daily dosages are not recommended for the treatment of RA, psoriatic arthritis (PsA), ankylosing spondylitis (AS), or polyarticular course juvenile idiopathic arthritis (pcJIA) [see Dosage and Administration (2.3, 2.4)].

MALIGNANCIES

Malignancies, including lymphomas and solid tumors, have occurred in patients treated with XELJANZ and other Janus kinase inhibitors used to treat inflammatory conditions. In RA patients, a higher rate of malignancies (excluding non-melanoma skin cancer (NMSC)) was observed in patients treated with XELJANZ tablets 5 mg or 10 mg twice a day compared with TNF blockers [see Warnings and Precautions (5.3)].

Lymphomas and lung cancers were observed at a higher rate in patients treated with XELJANZ tablets 5 mg or 10 mg twice a day in RA patients compared to those treated with TNF blockers. Patients who are current or past smokers are at additional increased risk.

MAJOR ADVERSE CARDIOVASCULAR EVENTS

RA patients 50 years of age and older with at least one cardiovascular risk factor, treated with XELJANZ tablets 5 mg or 10 mg twice daily, had a higher rate of major adverse cardiovascular events (MACE) (defined as cardiovascular death, myocardial infarction, and stroke), compared to those treated with TNF blockers. Patients who are current or past smokers are at additional increased risk. Discontinue XELJANZ/XELJANZ XR in patients that have experienced a myocardial infarction or stroke [see Warnings and Precautions (5.4)].

THROMBOSIS

Thrombosis, including pulmonary embolism, deep venous thrombosis, and arterial thrombosis have occurred in patients treated with XELJANZ and other Janus kinase inhibitors used to treat inflammatory conditions. Many of these events were serious and some resulted in death. RA patients 50 years of age and older with at least one cardiovascular risk factor treated with XELJANZ tablets 5 mg or 10 mg twice daily compared to TNF blockers had an observed increase in incidence of these events. Avoid XELJANZ/XELJANZ XR in patients at risk. Discontinue XELJANZ/XELJANZ XR and promptly evaluate patients with symptoms of thrombosis [see Warnings and Precautions (5.5)].

1 INDICATIONS AND USAGE

1.1 Rheumatoid Arthritis

XELJANZ tablets and XELJANZ XR (extended-release tablets) are indicated for the treatment of adult patients with moderately to severely active rheumatoid arthritis (RA), who have had an inadequate response or intolerance to one or more TNF blockers.

Limitations of Use

Use of XELJANZ tablets or XELJANZ XR in combination with biologic disease-modifying antirheumatic drugs (DMARDs) or with potent immunosuppressants such as azathioprine and cyclosporine is not recommended.

1.2 Psoriatic Arthritis

XELJANZ (tablets and oral solution) is indicated for the treatment of adult and pediatric patients 2 years of age and older with active psoriatic arthritis (PsA), who have had an inadequate response or intolerance to one or more TNF blockers.

XELJANZ XR (extended-release tablets) is indicated for the treatment of adults with active PsA who have had an inadequate response or intolerance to one or more TNF blockers.

Limitations of Use

Use of XELJANZ or XELJANZ XR in combination with biologic DMARDs or with potent immunosuppressants such as azathioprine and cyclosporine is not recommended.

1.3 Ankylosing Spondylitis

XELJANZ tablets and XELJANZ XR (extended-release tablets) are indicated for the treatment of adult patients with active ankylosing spondylitis (AS), who have had an inadequate response or intolerance to one or more TNF blockers.

Limitations of Use

Use of XELJANZ tablets or XELJANZ XR in combination with biologic DMARDs or potent immunosuppressants such as azathioprine and cyclosporine is not recommended.

1.4 Polyarticular Course Juvenile Idiopathic Arthritis

XELJANZ (tablets and oral solution) are indicated for the treatment of pediatric patients 2 years of age and older with of active polyarticular course juvenile idiopathic arthritis (pcJIA), who have had an inadequate response or intolerance to one or more TNF blockers.

Limitations of Use

Use of XELJANZ in combination with biologic DMARDs or with potent immunosuppressants such as azathioprine and cyclosporine is not recommended.

1.5 Ulcerative Colitis

XELJANZ tablets and XELJANZ XR (extended-release tablets) are indicated for the treatment of adult patients with moderately to severely active ulcerative colitis (UC), who have an inadequate response or intolerance to one or more TNF blockers.

Limitations of Use

Use of XELJANZ tablets or XELJANZ XR in combination with biological therapies for UC or with potent immunosuppressants such as azathioprine and cyclosporine is not recommended.

2 DOSAGE AND ADMINISTRATION

2.1 Recommended Evaluations and Immunization Prior to Treatment Initiation

Prior to initiating XELJANZ (tablets and oral solution) or XELJANZ XR (extended-release tablets), consider performing the following:

- Active and latent tuberculosis (TB) infection evaluation: If the patient has latent TB, treat for TB prior to XELJANZ/XELJANZ XR treatment [see Warnings and Precautions (5.1)].
- Viral hepatitis screening in accordance with clinical guidelines [see Warnings and Precautions (5.1)].
- A complete blood count: Avoid initiation of XELJANZ/XELJANZ XR treatment in patients with a lymphocyte count less than 500 cells/mm^3, absolute neutrophil count less than 1000 cells/mm^3, or hemoglobin level less than 9 g/dL [see Warnings and Precautions (5.8)].
- Baseline hepatic function evaluation: XELJANZ/XELJANZ XR is not recommended for patients with severe hepatic impairment [see Use in Specific Populations (8.7) and Clinical Pharmacology (12.3)].
- Update immunizations according to current immunization guidelines. The interval between live vaccinations and initiation of XELJANZ/XELJANZ XR should be in accordance with current vaccination guidelines regarding immunosuppressive agents [see Warnings and Precautions (5.9)].

2.2 Important Administration Instructions

- XELJANZ XR (extended-release tablets) is not substitutable with XELJANZ (tablets and oral solution). Switching between XELJANZ and XELJANZ XR should be made by the healthcare provider.
- Dose interruption is recommended for management of lymphopenia, neutropenia, and anemia [see Warnings and Precautions (5.8) and Adverse Reactions (6.1)].
- Interrupt use of XELJANZ/XELJANZ XR if a patient develops a serious infection until the infection is controlled [see Warnings and Precautions (5.1)].
- Take XELJANZ/XELJANZ XR with or without food [see Clinical Pharmacology (12.3)].
- Swallow XELJANZ XR whole and intact. Do not crush, split, or chew the extended-release tablets [see Clinical Pharmacology (12.3)].

2.3 Recommended Dosage in Adults with Rheumatoid Arthritis, Psoriatic Arthritis, and Ankylosing Spondylitis

Table 1 displays the recommended dosage of XELJANZ tablets and XELJANZ XR (extended-release tablets) for adults with RA, PsA, and AS [see Indication and Usage (1.1, 1.2, 1.3)] with and without renal impairment (including those who are undergoing hemodialysis) or hepatic impairment [see Use in Specific Populations (8.6, 8.7)]. The table also displays the recommended dosage modifications for patients concomitantly using CYP2C19 and/or CYP3A4 inhibitors [see Drug Interactions (7) and Clinical Pharmacology (12.3)], and patients with lymphopenia, neutropenia, or anemia.

Table 1: Recommended Dosage of XELJANZ Tablets and XELJANZ XR in Adults with Rheumatoid Arthritis, Psoriatic Arthritis, or Ankylosing Spondylitis
Adults | XELJANZ Tablets | XELJANZ XR; (extended-release tablets)
Patients with Normal Renal and Hepatic Function [Excludes patients who concomitantly use XELJANZ tablets/XELJANZ XR with strong CYP3A4 inhibitor(s) or moderate CYP3A4 inhibitor(s) and strong CYP2C19 inhibitor(s), as well as patients with lymphocyte count less than 500 cells/mm^3, ANC <1000 cells/mm^3, or hemoglobin less than 8 g/dL or a decrease of more than 2 g/dL.] | 5 mg twice daily | 11 mg once daily
Recommended Dosage in Patients with Renal Impairment (RI) [Tofacitinib PK was evaluated in subjects with varying degrees of renal impairment, where the severity of renal impairment was defined based on creatinine clearance (CLcr) estimated using the Cockcroft‑Gault equation: CLcr >80 mL/min (normal renal function); >50 and ≤80 mL/min (mild renal impairment); ≥30 and ≤50 mL/min (moderate renal impairment); <30 mL/min (severe renal impairment).]
Mild RI; (CLcr >50 and ≤80 mL/min) | 5 mg twice daily | 11 mg once daily
Moderate RI; (CLcr ≥30 and ≤50 mL/min) | 5 mg once daily | XELJANZ tablets 5 mg once daily
Severe RI; (CLcr <30 mL/min) | 5 mg once daily | XELJANZ tablets 5 mg once daily
Severe RI; (CLcr <30 mL/min) | For patients undergoing hemodialysis, administer the dose after the dialysis session on dialysis days. If a dose was taken before the dialysis procedure, supplemental doses are not recommended after dialysis.
Recommended Dosage in Patients with Hepatic Impairment (HI)
Mild HI; (Child-Pugh A) | 5 mg twice daily | 11 mg once daily
Moderate HI; (Child-Pugh B) | 5 mg once daily | XELJANZ tablets 5 mg once daily
Severe HI; (Child-Pugh C) | Use of XELJANZ tablets/XELJANZ XR is not recommended.
Dosage Modifications with Concomitant Use of CYP3A4 and/or CYP2C19 Inhibitor(s)
Strong CYP2C19 inhibitor(s) | 5 mg twice daily | 11 mg once daily
Moderate CYP2C19 inhibitor(s) | 5 mg twice daily | 11 mg once daily
Moderate CYP3A4 inhibitor(s) | 5 mg twice daily | 11 mg once daily
Moderate CYP3A4 inhibitor(s) with strong CYP2C19 inhibitor(s) (e.g., fluconazole) | 5 mg once daily | XELJANZ tablets 5 mg once daily
Strong CYP3A4 inhibitor(s) | 5 mg once daily | XELJANZ tablets 5 mg once daily
Dosage Modifications for Lymphopenia, Neutropenia, or Anemia
Patients with lymphocyte count less than 500 cells/mm^3, confirmed by repeat testing | Discontinue dosing.
Patients with ANC less than 500 cells/mm^3 | Discontinue dosing.
Patients with ANC 500 to 1000 cells/mm^3 | Interrupt dosing. When ANC is greater than 1000, resume 5 mg twice daily. | Interrupt dosing. When ANC is greater than 1000, resume 11 mg once daily.
Patients with hemoglobin less than 8 g/dL or a decrease of more than 2 g/dL | Interrupt dosing until hemoglobin values have normalized.

Switching from XELJANZ Tablets to XELJANZ XR Extended-Release Tablets

Patients treated with XELJANZ tablets 5 mg twice daily may be switched to XELJANZ XR extended-release tablets 11 mg once daily the day following the last dose of XELJANZ tablets 5 mg.

2.4 Recommended Dosage in Pediatric Patients 2 Years of Age and Older with Psoriatic Arthritis or Polyarticular Course Juvenile Idiopathic Arthritis

Table 2 displays the recommended body weight-based dosages for XELJANZ tablets and XELJANZ oral solution in pediatric patients 2 years of age and older with PsA or pcJIA [see Indication and Usage (1.2, 1.4)] with and without renal impairment (including those who are undergoing hemodialysis) or hepatic impairment [see Use in Specific Populations (8.6, 8.7)]. The table also includes recommended dosage modification for pediatric patients concomitantly using CYP2C19 and/or CYP3A4 inhibitors [see Drug Interactions (7) and Clinical Pharmacology (12.3)], and pediatric patients with lymphopenia, neutropenia, or anemia.

Administer XELJANZ oral solution using the included press-in bottle adapter and oral dosing syringe [see Instructions for Use].

Table 2: Recommended Dosage of XELJANZ Tablets and XELJANZ Oral Solution in Pediatric Patients 2 Years of Age and Older with PsA or pcJIA
Pediatric Patients 2 Years of Age and Older | XELJANZ tablets and XELJANZ oral solution
Patients with Normal Renal and Hepatic Function [Excludes patients who concomitantly use XELJANZ (tablets and oral solution) with strong CYP3A4 inhibitor(s) or moderate CYP3A4 inhibitor(s) and strong CYP2C19 inhibitor(s), as well as patients with lymphocyte count less than 500 cells/mm^3, ANC <1000 cells/mm^3, or hemoglobin less than 8 g/dL or a decrease of more than 2 g/dL.] | - 10 kg ≤ body weight <20 kg: 3.2 mg (3.2 mL oral solution) twice daily - 20 kg ≤ body weight <40 kg: 4 mg (4 mL oral solution) twice daily - Body weight ≥40 kg: 5 mg (one 5 mg tablet or 5 mL oral solution) twice daily [Patients treated with XELJANZ oral solution 5 mL may be switched to XELJANZ tablets 5 mg.]
Recommended Dosage in Patients with Renal Impairment (RI)
Mild RI | Same as patients with normal renal function.
Moderate RI | - 10 kg ≤ body weight <20 kg: 3.2 mg once daily - 20 kg ≤ body weight <40 kg: 4 mg once daily - Body weight ≥40 kg: 5 mg once daily
Severe RI | - 10 kg ≤ body weight <20 kg: 3.2 mg once daily - 20 kg ≤ body weight <40 kg: 4 mg once daily - Body weight ≥40 kg: 5 mg once daily
Severe RI | For patients undergoing hemodialysis, administer the dose after the dialysis session on dialysis days. If a dose was taken before the dialysis procedure, supplemental doses are not recommended after dialysis.
Recommended Dosage in Patients with Hepatic Impairment (HI)
Mild HI | Same as patients with normal hepatic function.
Moderate HI | - 10 kg ≤ body weight <20 kg: 3.2 mg once daily - 20 kg ≤ body weight <40 kg: 4 mg once daily - Body weight ≥40 kg: 5 mg once daily
Severe HI | Use of XELJANZ tablets/XELJANZ oral solution is not recommended.
Dosage Modifications with Concomitant Use of CYP3A4 and/or CYP2C19 Inhibitor(s)
Strong CYP2C19 inhibitor(s) | No dosage modification is recommended.
Moderate CYP2C19 inhibitor(s) | No dosage modification is recommended.
Moderate CYP3A4 inhibitor(s) | No dosage modification is recommended.
Moderate CYP3A4 inhibitor(s) with strong CYP2C19 inhibitor(s) (e.g., fluconazole) | - 10 kg ≤ body weight <20 kg: 3.2 mg once daily - 20 kg ≤ body weight <40 kg: 4 mg once daily - Body weight ≥40 kg: 5 mg once daily
Strong CYP3A4 inhibitor(s) | - 10 kg ≤ body weight <20 kg: 3.2 mg once daily - 20 kg ≤ body weight <40 kg: 4 mg once daily - Body weight ≥40 kg: 5 mg once daily
Dosage Modifications for Lymphopenia, Neutropenia, or Anemia
Patients with lymphocyte count less than 500 cells/mm^3, confirmed by repeat testing | Discontinue dosing.
Patients with ANC less than 500 cells/mm^3 | Discontinue dosing.
Patients with ANC 500 to 1000 cells/mm^3 | Interrupt dosing until ANC is greater than 1000 cells/mm^3.
Patients with hemoglobin less than 8 g/dL or a decrease of more than 2 g/dL | Interrupt dosing until hemoglobin values have normalized.

2.5 Recommended Dosage in Adults with Ulcerative Colitis

Table 3 displays the recommended dosage of XELJANZ tablets and XELJANZ XR (extended-release tablets) in adult patients with ulcerative colitis (UC) [see Indications and Usage (1.5)] with and without renal impairment (including those who are undergoing hemodialysis) or hepatic impairment [see Use in Specific Populations (8.6, 8.7)]. Table 4 displays the recommended dosage modification for patients concomitantly using CYP2C19 and/or CYP3A4 inhibitors [see Drug Interactions (7) and Clinical Pharmacology (12.3)], and patients with lymphopenia, neutropenia, or anemia.

Table 3: Recommended Dosage of XELJANZ Tablets and XELJANZ XR in Adults with Ulcerative Colitis With and Without Renal Impairment or Hepatic Impairment
Adults | XELJANZ tablets | XELJANZ XR (extended-release tablets)
Patients with Normal Renal and Hepatic Function [Excludes patients who concomitantly use XELJANZ tablets/XELJANZ XR with strong CYP3A4 inhibitor(s) or moderate CYP3A4 inhibitor(s) and strong CYP2C19 inhibitor(s), as well as patients with lymphocyte count less than 500 cells/mm^3, ANC <1000 cells/mm^3, or hemoglobin less than 8 g/dL or a decrease of more than 2 g/dL.] | Induction: 10 mg twice daily for at least 8 weeks [see Clinical Studies (14.5)]; evaluate patients and transition to maintenance therapy depending on therapeutic response. If needed continue 10 mg twice daily for a maximum of 16 weeks. Discontinue 10 mg twice daily after 16 weeks if adequate therapeutic response is not achieved. | Induction: 22 mg once daily for at least 8 weeks; evaluate patients and transition to maintenance therapy depending on therapeutic response. If needed continue 22 mg once daily for a maximum of 16 weeks. Discontinue 22 mg once daily after 16 weeks if adequate therapeutic response is not achieved.
Patients with Normal Renal and Hepatic Function [Excludes patients who concomitantly use XELJANZ tablets/XELJANZ XR with strong CYP3A4 inhibitor(s) or moderate CYP3A4 inhibitor(s) and strong CYP2C19 inhibitor(s), as well as patients with lymphocyte count less than 500 cells/mm^3, ANC <1000 cells/mm^3, or hemoglobin less than 8 g/dL or a decrease of more than 2 g/dL.] | Maintenance: 5 mg twice daily.; For patients with loss of response during maintenance treatment, may consider a dosage of 10 mg twice daily (limited to the shortest duration), with careful consideration of the benefits and risks for the individual patient. Use the lowest effective dosage needed to maintain response. | Maintenance: 11 mg once daily.; For patients with loss of response during maintenance treatment, may consider a dosage of 22 mg once daily (limited to the shortest duration), with careful consideration of the benefits and risks for the individual patient. Use the lowest effective dose needed to maintain response.
Recommended Dosage in Patients with Renal Impairment (RI) [Tofacitinib PK was evaluated in subjects with varying degrees of renal impairment, where the severity of renal impairment was defined based on creatinine clearance (CLcr) estimated using the Cockcroft‑Gault equation: CLcr >80 mL/min (normal renal function); CLcr >50 and ≤80 mL/min (mild renal impairment); ≥30 and ≤50 mL/min (moderate renal impairment); <30 mL/min (severe renal impairment).]
Mild RI (CLcr >50 and ≤80 mL/min) | Same as patients with normal renal function.
Moderate RI (CLcr ≥30 and ≤50 mL/min) | Induction: 5 mg twice daily for at least 8 weeks [see Clinical Studies (14.5)]; evaluate patients and transition to maintenance therapy depending on therapeutic response. If needed continue 5 mg twice daily for a maximum of 16 weeks. Discontinue 5 mg twice daily after 16 weeks if adequate therapeutic response is not achieved. | Induction: 11 mg once daily for at least 8 weeks; evaluate patients and transition to maintenance therapy depending on therapeutic response. If needed continue 11 mg once daily for a maximum of 16 weeks. Discontinue 11 mg once daily after 16 weeks if adequate therapeutic response is not achieved.
Severe RI (CLcr <30 mL/min) | Maintenance: 5 mg once daily. For patients with loss of response during maintenance treatment, may consider a dosage of 5 mg twice daily (limited to the shortest duration), with careful consideration of the benefits and risks for the individual patient. Use the lowest effective dosage needed to maintain response.; For patients undergoing hemodialysis, administer the dose after the dialysis session on dialysis days. If a dose was taken before the dialysis procedure, supplemental doses are not recommended after dialysis. | Maintenance: XELJANZ XR is not recommended. See Maintenance Dosage for XELJANZ tablets for Moderate or Severe RI.; For patients undergoing hemodialysis, administer the dose after the dialysis session on dialysis days. If a dose was taken before the dialysis procedure, supplemental doses are not recommended after dialysis.
Recommended Dosage in Patients with Hepatic Impairment (HI)
Mild HI (Child-Pugh A) | Same as patients with normal hepatic function.
Moderate HI (Child-Pugh B) | Induction: 5 mg twice daily for at least 8 weeks [see Clinical Studies (14.5)]; evaluate patients and transition to maintenance therapy depending on therapeutic response. If needed continue 5 mg twice daily for a maximum of 16 weeks. Discontinue 5 mg twice daily after 16 weeks if adequate therapeutic response is not achieved. | Induction: 11 mg once daily for at least 8 weeks; evaluate patients and transition to maintenance therapy depending on therapeutic response. If needed continue 11 mg once daily for a maximum of 16 weeks. Discontinue 11 mg once daily after 16 weeks if adequate therapeutic response is not achieved.
Moderate HI (Child-Pugh B) | Maintenance: 5 mg once daily.; For patients with loss of response during maintenance treatment, may consider a dosage of 5 mg twice daily (limited to the shortest duration), with careful consideration of the benefits and risks for the individual patient. Use the lowest effective dosage needed to maintain response. | Maintenance: XELJANZ XR is not recommended. See Maintenance Dosage for XELJANZ tablets for Moderate HI.
Severe HI (Child-Pugh C) | Use of XELJANZ tablets/XELJANZ XR is not recommended.

Table 4: Dosage Modifications of XELJANZ Tablets and XELJANZ XR Due to Drug Interactions and for Lymphopenia, Neutropenia or Anemia in Adults with Ulcerative Colitis
Adults | XELJANZ Tablets | XELJANZ XR (extended-release tablets)
Dosage Modifications with Concomitant Use of CYP3A4 and/or CYP2C19 Inhibitor(s)
Strong CYP2C19 inhibitor(s) | No dosage modification is recommended.
Moderate CYP2C19 inhibitor(s) | No dosage modification is recommended.
Moderate CYP3A4 inhibitor(s) | No dosage modification is recommended.
Moderate CYP3A4 inhibitor(s) with strong CYP2C19 inhibitor(s) (e.g., fluconazole) | Induction: 5 mg twice daily for at least 8 weeks [see Clinical Studies (14.5)]; evaluate patients and transition to maintenance therapy depending on therapeutic response. If needed continue 5 mg twice daily for a maximum of 16 weeks. Discontinue 5 mg twice daily after 16 weeks if adequate therapeutic response is not achieved. | Induction: 11 mg once daily for at least 8 weeks; evaluate patients and transition to maintenance therapy depending on therapeutic response. If needed continue 11 mg once daily for a maximum of 16 weeks. Discontinue 11 mg once daily after 16 weeks if adequate therapeutic response is not achieved.
Strong CYP3A4 inhibitor(s) | Induction: 5 mg twice daily for at least 8 weeks [see Clinical Studies (14.5)]; evaluate patients and transition to maintenance therapy depending on therapeutic response. If needed continue 5 mg twice daily for a maximum of 16 weeks. Discontinue 5 mg twice daily after 16 weeks if adequate therapeutic response is not achieved. | Induction: 11 mg once daily for at least 8 weeks; evaluate patients and transition to maintenance therapy depending on therapeutic response. If needed continue 11 mg once daily for a maximum of 16 weeks. Discontinue 11 mg once daily after 16 weeks if adequate therapeutic response is not achieved.
Strong CYP3A4 inhibitor(s) | Maintenance: 5 mg once daily.; For patients with loss of response during maintenance treatment, may consider a dosage of 5 mg twice daily (limited to the shortest duration), with careful consideration of the benefits and risks for the individual patient. Use the lowest effective dosage needed to maintain response. | Maintenance: XELJANZ XR is not recommended. see Maintenance Dosage for XELJANZ tablets for Strong CYP3A4 inhibitors.
Dosage Modifications for Lymphopenia, Neutropenia, or Anemia
Lymphocyte count less than 500 cells/mm^3, confirmed by repeat testing | Discontinue dosing.
ANC less than 500 cells/mm^3 | Discontinue dosing.
ANC 500 to 1000 cells/mm^3 | If taking:; - 10 mg twice daily, reduce to 5 mg twice daily. When ANC is greater than 1000, increase to 10 mg twice daily based on clinical response. - 5 mg twice daily, interrupt dosing. When ANC is greater than 1000, resume 5 mg twice daily. | If taking:; - 22 mg once daily, reduce to 11 mg once daily. When ANC is greater than 1000, increase to 22 mg once daily based on clinical response. - 11 mg once daily, interrupt dosing. When ANC is greater than 1000, resume 11 mg once daily.
Hemoglobin less than 8 g/dL or a decrease of more than 2 g/dL | Interrupt dosing until hemoglobin values have normalized.

Switching from XELJANZ Tablets to XELJANZ XR Extended-Release Tablets

Patients treated with XELJANZ tablets:

- 5 mg twice daily may be switched to XELJANZ XR extended-release tablets 11 mg once daily the day following the last dose of XELJANZ tablets 5 mg.
- 10 mg twice daily may be switched to XELJANZ XR extended-release tablets 22 mg once daily the day following the last dose of XELJANZ tablets 10 mg.

3 DOSAGE FORMS AND STRENGTHS

XELJANZ tablets:

- 5 mg of tofacitinib: White, round, immediate-release film-coated tablets, debossed with “Pfizer” on one side, and “JKI 5” on the other side.
- 10 mg of tofacitinib: Blue, round, immediate-release film-coated tablets, debossed with “Pfizer” on one side, and “JKI 10” on the other side.

XELJANZ XR extended-release tablets:

- 11 mg of tofacitinib: Pink, oval, extended-release film-coated tablets with a drilled hole at one end of the tablet band and “JKI 11” printed on one side of the tablet.
- 22 mg of tofacitinib: Beige, oval, extended-release film-coated tablets with a drilled hole at one end of the tablet band and “JKI 22” printed on one side of the tablet.

XELJANZ oral solution:

1 mg/mL of tofacitinib: Clear, colorless oral solution.

4 CONTRAINDICATIONS

None.

5 WARNINGS AND PRECAUTIONS

5.1 Serious Infections

Serious and sometimes fatal infections may occur with XELJANZ (tablets and oral solution) and XELJANZ XR (extended-release tablets). Serious and sometimes fatal infections due to bacterial, mycobacterial, invasive fungal, viral, or other opportunistic pathogens have been reported in patients receiving XELJANZ. The most common serious infections reported with XELJANZ included pneumonia, cellulitis, herpes zoster, urinary tract infection, diverticulitis, and appendicitis. Among opportunistic infections, tuberculosis and other mycobacterial infections, cryptococcosis, histoplasmosis, esophageal candidiasis, pneumocystosis, multi-dermatomal herpes zoster, cytomegalovirus infections, BK virus infection, and listeriosis were reported with XELJANZ. Some patients have presented with disseminated rather than localized disease, and were often taking concomitant immunomodulating agents such as methotrexate or corticosteroids.

In the UC population, treatment with XELJANZ tablets 10 mg twice daily was associated with greater risk of serious infections compared to 5 mg twice daily. Additionally, opportunistic herpes zoster infections (including meningoencephalitis, ophthalmologic, and disseminated cutaneous) were seen in patients who were treated with XELJANZ tablets 10 mg twice daily.

Other serious infections that were not reported in clinical studies may also occur (e.g., coccidioidomycosis).

Avoid use of XELJANZ/XELJANZ XR in patients with an active, serious infection, including localized infections. The risks and benefits of treatment should be considered prior to initiating XELJANZ/XELJANZ XR in patients:

- with chronic or recurrent infection
- who have been exposed to tuberculosis
- with a history of a serious or an opportunistic infection
- who have resided or traveled in areas of endemic tuberculosis or endemic mycoses; or
- with underlying conditions that may predispose them to infection.

Closely monitor patients for the development of signs and symptoms of infection during and after treatment with XELJANZ/XELJANZ XR. Interrupt XELJANZ/XELJANZ XR if a patient develops a serious infection, an opportunistic infection, or sepsis. In patients who develop a new infection during treatment with XELJANZ/XELJANZ XR, promptly complete diagnostic testing appropriate for an immunocompromised patient; initiate appropriate antimicrobial therapy, and monitor the patients closely.

Caution is also recommended in patients with a history of chronic lung disease, or in those who develop interstitial lung disease, as they may be more prone to infections.

Risk of infection may be higher with increasing degrees of lymphopenia and consideration should be given to lymphocyte counts when assessing individual patient risk of infection. Discontinuation and monitoring criteria for lymphopenia are recommended [see Dosage and Administration (2.3, 2.4, 2.5)].

Tuberculosis

Evaluate and test patients for latent or active tuberculosis (TB) infection prior to and per applicable guidelines during administration of XELJANZ/XELJANZ XR.

Consider anti-TB therapy prior to administration of XELJANZ/XELJANZ XR in patients with a past history of latent or active TB in whom an adequate course of treatment cannot be confirmed, and for patients with a negative test for latent TB but who have risk factors for TB infection. Consultation with a physician with expertise in the treatment of TB is recommended to aid in the decision about whether initiating anti-TB therapy is appropriate for an individual patient.

Monitor patients closely for the development of signs and symptoms of TB, including patients who tested negative for latent TB infection prior to initiating therapy.

Treat patients with latent TB with standard antimycobacterial therapy before administering XELJANZ/XELJANZ XR.

Viral Reactivation

Viral reactivation, including cases of herpes virus reactivation (e.g., herpes zoster), were observed in clinical studies with XELJANZ. Postmarketing cases of hepatitis B reactivation have been reported in patients treated with XELJANZ. The impact of XELJANZ/XELJANZ XR on chronic viral hepatitis reactivation is unknown. Patients who screened positive for hepatitis B or C were excluded from clinical trials. Perform screening for viral hepatitis in accordance with clinical guidelines before starting therapy with XELJANZ/XELJANZ XR. The risk of herpes zoster is increased in patients treated with XELJANZ/XELJANZ XR and appears to be higher in patients treated with XELJANZ in Japan and Korea.

5.2 Increased Risk of Mortality

Increased risk of mortality may occur with XELJANZ (tablets and oral solution) and XELJANZ XR (extended-release tablets). Adult patients with rheumatoid arthritis (RA), 50 years of age and older, with at least one cardiovascular risk factor treated with XELJANZ tablets 5 mg or 10 mg twice a day had a higher observed rate of all-cause mortality, including sudden cardiovascular death, compared to those treated with TNF blockers in a large, randomized, postmarketing safety study (RA Safety Study 1). The incidence rate of all-cause mortality per 100 patient-years was 1.23 for XELJANZ tablets 10 mg twice a day, 0.88 for XELJANZ tablets 5 mg twice a day, and 0.69 for TNF blockers [see Clinical Studies (14.6)]. Consider the benefits and risks for the individual patient prior to initiating or continuing therapy with XELJANZ/XELJANZ XR.

XELJANZ 10 mg twice daily (or XELJANZ XR 22 mg once daily) dosages are not recommended for the treatment of RA, PsA, AS, or pcJIA [see Dosage and Administration (2.3, 2.4)].

For the treatment of UC, use XELJANZ/XELJANZ XR at the lowest effective dose and for the shortest duration needed to achieve/maintain therapeutic response [see Dosage and Administration (2.5)].

5.3 Malignancy and Lymphoproliferative Disorders

Malignancies and lymphoproliferative disorders may occur with XELJANZ (tablets and oral solution) and XELJANZ XR (extended-release tablets). Malignancies, including lymphomas and solid cancers, were observed in clinical studies of XELJANZ [see Adverse Reactions (6.1)].

Other malignancies were observed in XELJANZ clinical studies and the postmarketing setting, including, but not limited to, lung cancer, breast cancer, melanoma, prostate cancer, and pancreatic cancer.

In RA Safety Study 1, a higher rate of malignancies (excluding non-melanoma skin cancer (NMSC)) was observed in patients treated with XELJANZ tablets 5 mg or 10 mg twice a day compared with TNF blockers. The incidence rate of malignancies (excluding NMSC) per 100 patient-years was 1.13 for XELJANZ tablets 10 mg twice a day, 1.13 for XELJANZ tablets 5 mg twice a day, and 0.77 for TNF blockers. Patients who are current or past smokers are at additional increased risk [see Clinical Studies (14.6)].

Lymphomas and lung cancers, which are a subset of all malignancies in RA Safety Study 1, were observed at a higher rate in patients treated with XELJANZ tablets 5 mg twice a day and XELJANZ tablets 10 mg twice a day compared to those treated with TNF blockers. The incidence rate of lymphomas per 100 patient-years was 0.11 for XELJANZ tablets 10 mg twice a day, 0.07 for XELJANZ tablets 5 mg twice a day, and 0.02 for TNF blockers. The incidence rate of lung cancers per 100 patient-years among current and past smokers was 0.59 for XELJANZ tablets 10 mg twice a day, 0.48 for XELJANZ tablets 5 mg twice a day, and 0.27 for TNF blockers [see Clinical Studies (14.6)].

Consider the benefits and risks for the individual patient prior to initiating or continuing therapy with XELJANZ/XELJANZ XR, particularly in patients with a known malignancy (other than a successfully treated NMSC), patients who develop a malignancy while on treatment, and patients who are current or past smokers. XELJANZ 10 mg twice daily (or XELJANZ XR 22 mg once daily) dosages are not recommended for the treatment of RA, PsA, AS, or pcJIA [see Dosage and Administration (2.3, 2.4)].

Non-Melanoma Skin Cancer

Non-melanoma skin cancers (NMSCs) have been reported in patients treated with XELJANZ tablets. Periodic skin examination is recommended for patients who are at increased risk for skin cancer. In the UC population, treatment with XELJANZ tablets 10 mg twice daily was associated with greater risk of NMSC than treatment with placebo.

5.4 Major Adverse Cardiovascular Events

Major adverse cardiovascular events may occur with XELJANZ (tablets and oral solution) and XELJANZ XR (extended-release tablets). In RA Safety Study 1, patients with RA who were 50 years of age and older with at least one cardiovascular risk factor and treated with XELJANZ tablets 5 mg or 10 mg twice daily had a higher rate of major adverse cardiovascular events (MACE) defined as cardiovascular death, non-fatal myocardial infarction (MI), and non-fatal stroke, compared to those treated with TNF blockers. The incidence rate of MACE per 100 patient-years was 1.11 for XELJANZ tablets 10 mg twice a day, 0.91 for XELJANZ tablets 5 mg twice a day, and 0.79 for TNF blockers. The incidence rate of fatal or non-fatal myocardial infarction per 100 patient-years was 0.39 for XELJANZ tablets 10 mg twice a day, 0.36 for XELJANZ tablets 5 mg twice a day, and 0.2 for TNF blockers [see Clinical Studies (14.6)]. Patients who are current or past smokers are at additional increased risk.

Consider the benefits and risks for the individual patient prior to initiating or continuing therapy with XELJANZ/XELJANZ XR, particularly in patients who are current or past smokers and patients with other cardiovascular risk factors. Inform patients about the symptoms of serious cardiovascular events and the steps to take if they occur. Discontinue XELJANZ/XELJANZ XR in patients that have experienced a MI or stroke. XELJANZ 10 mg twice daily (or XELJANZ XR 22 mg once daily) dosages are not recommended for the treatment of RA, PsA, AS, or pcJIA [see Dosage and Administration (2.3, 2.4)].

5.5 Thrombosis

Thrombosis may occur with XELJANZ (tablets and oral solution) and XELJANZ XR (extended-release tablets). Thrombosis, including pulmonary embolism (PE), deep venous thrombosis (DVT), and arterial thrombosis, have occurred in patients treated with XELJANZ and other Janus kinase (JAK) inhibitors used to treat inflammatory conditions. Many of these events were serious and some resulted in death [see Warnings and Precautions (5.2)].

Patients with RA 50 years of age and older with at least one cardiovascular risk factor treated with XELJANZ tablets 5 mg or 10 mg twice daily compared to TNF blockers in RA Safety Study 1 had an observed increase in incidence of these thrombotic events. The incidence rate of DVT per 100 patient-years was 0.28 for XELJANZ tablets 10 mg twice a day, 0.22 for XELJANZ tablets 5 mg twice a day, and 0.16 for TNF blockers. The incidence rate of PE per 100 patient-years was 0.49 for XELJANZ tablets 10 mg twice a day, 0.18 for XELJANZ tablets 5 mg twice a day, and 0.05 for TNF blockers [see Clinical Studies (14.6)].

XELJANZ 10 mg twice daily (or XELJANZ XR 22 mg once daily) dosages are not recommended for the treatment of RA, PsA, AS, or pcJIA [see Dosage and Administration (2.3, 2.4)].

In a long-term extension study in patients with UC, five cases of pulmonary embolism were reported in patients taking XELJANZ 10 mg twice daily, including one death in a patient with advanced cancer.

Promptly evaluate patients with symptoms of thrombosis and discontinue XELJANZ/XELJANZ XR in patients with symptoms of thrombosis.

Avoid XELJANZ/XELJANZ XR in patients that may be at increased risk of thrombosis. For the treatment of UC, use XELJANZ tablets or XELJANZ XR at the lowest effective dose and for the shortest duration needed to achieve/maintain therapeutic response [see Dosage and Administration (2.5)].

5.6 Gastrointestinal Perforations

Gastrointestinal perforations may occur with XELJANZ (tablets and oral solution) and XELJANZ XR (extended-release tablets). Events of gastrointestinal perforation have been reported in clinical studies with XELJANZ tablets, although the role of JAK inhibition in these events is not known. In these studies, many patients with RA received background therapy with nonsteroidal anti-inflammatory drugs (NSAIDs).

There was no discernable difference in frequency of gastrointestinal perforation between the placebo and the XELJANZ tablets treatment groups in clinical trials of patients with UC, and many of them were receiving background corticosteroids.

Promptly evaluate patients treated with XELJANZ/XELJANZ XR who may be at increased risk for gastrointestinal perforation (e.g., patients with a history of diverticulitis or taking NSAIDs) and who present with new onset abdominal symptoms for early identification of gastrointestinal perforation [see Adverse Reactions (6.1)].

5.7 Hypersensitivity Reactions

Hypersensitivity reactions may occur with XELJANZ (tablets and oral solution) and XELJANZ XR (extended-release tablets). Reactions such as angioedema and urticaria that may reflect drug hypersensitivity have been observed in patients receiving XELJANZ/XELJANZ XR. Some events were serious. If a serious hypersensitivity reaction occurs, promptly discontinue XELJANZ/XELJANZ XR while evaluating the potential cause or causes of the reaction [see Adverse Reactions (6.2)].

5.8 Laboratory Abnormalities

Laboratory abnormalities may occur with XELJANZ (tablets and oral solution) and XELJANZ XR (extended-release tablets).

Lymphocyte Abnormalities

Treatment with XELJANZ tablets was associated with initial lymphocytosis at one month of XELJANZ tablets treatment followed by a gradual decrease in mean absolute lymphocyte counts below the baseline of approximately 10% during 12 months of therapy. Lymphocyte counts less than 500 cells/mm^3 in these patients were associated with an increased incidence of treated and serious infections.

- Monitor lymphocyte counts at baseline and every 3 months thereafter.
- Avoid initiation of XELJANZ/XELJANZ XR treatment in patients with a low lymphocyte count (i.e., less than 500 cells/mm^3). In patients who develop a confirmed absolute lymphocyte count less than 500 cells/mm^3, treatment with XELJANZ/XELJANZ XR is not recommended.

Neutropenia

Treatment with XELJANZ tablets was associated with an increased incidence of neutropenia (less than 2000 cells/mm^3) compared to treatment with placebo.

- Monitor neutrophil counts at baseline and after 4-8 weeks of treatment and every 3 months thereafter.
- Avoid initiation of XELJANZ/XELJANZ XR treatment in patients with a low neutrophil count (i.e., ANC less than 1000 cells/mm^3). For patients who develop a persistent ANC of 500 to 1000 cells/mm^3, interrupt dosing until ANC is greater than or equal to 1000 cells/mm^3. In patients who develop an ANC less than 500 cells/mm^3, treatment with XELJANZ/XELJANZ XR is not recommended.

Anemia

- Monitor hemoglobin at baseline and after 4-8 weeks of treatment and every 3 months thereafter.
- Avoid initiation of XELJANZ/XELJANZ XR treatment in patients with a low hemoglobin level (i.e., less than 9 g/dL). Interrupt treatment with XELJANZ/XELJANZ XR in patients who develop hemoglobin levels less than 8 g/dL or whose hemoglobin level drops greater than 2 g/dL on treatment until hemoglobin values have normalized.

Liver Enzyme Elevations

Treatment with XELJANZ tablets was associated with an increased incidence of liver enzyme elevation compared to treatment with placebo. Most of these abnormalities occurred in studies with background DMARD therapy (primarily methotrexate).

- Routine monitoring of liver tests and prompt investigation of the causes of liver enzyme elevations is recommended to identify potential cases of drug-induced liver injury.
- If drug-induced liver injury is suspected, interrupt the administration of XELJANZ/XELJANZ XR until this diagnosis has been excluded.

Lipid Elevations

Treatment with XELJANZ tablets was associated with dose-dependent increases in lipid parameters including total cholesterol, low-density lipoprotein (LDL) cholesterol, and high-density lipoprotein (HDL) cholesterol. Maximum changes in these lipid parameters were generally observed within 6 weeks. There were no clinically relevant changes in LDL/HDL cholesterol ratios. The effect of these lipid parameter elevations on cardiovascular morbidity and mortality has not been determined.

- Perform assessment of lipid parameters approximately 4-8 weeks following initiation of XELJANZ/XELJANZ XR therapy.
- Manage patients according to clinical guidelines [e.g., National Cholesterol Educational Program (NCEP)] for the management of hyperlipidemia.

5.9 Vaccinations

Avoid use of live vaccines concurrently with XELJANZ (tablets and oral solution) or XELJANZ XR (extended-release tablets). Prior to initiating XELJANZ/XELJANZ XR therapy, update immunizations in agreement with current immunization guidelines. The interval between live vaccinations and initiation of XELJANZ/XELJANZ XR therapy should be in accordance with current vaccination guidelines regarding immunosuppressive agents.

5.10 Risk of Gastrointestinal Obstruction with XELJANZ XR - A Non-Deformable Extended-Release Formulation

Gastrointestinal obstruction may occur with XELJANZ XR (extended-release tablets). Avoid use of XELJANZ XR in patients with pre-existing severe gastrointestinal narrowing (pathologic or iatrogenic). There have been rare reports of obstructive symptoms in patients with known strictures in association with the ingestion of other drugs utilizing a non-deformable extended-release formulation.

6 ADVERSE REACTIONS

The following clinically significant adverse reactions are described elsewhere in the labeling:

- Serious Infections [see Warnings and Precautions (5.1)]
- Increased Risk of Mortality [see Warnings and Precautions (5.2)]
- Malignancy and Lymphoproliferative Disorders [see Warnings and Precautions (5.3)]
- Major Adverse Cardiovascular Events [see Warnings and Precautions (5.4)]
- Thrombosis [see Warnings and Precautions (5.5)]
- Gastrointestinal Perforations [see Warnings and Precautions (5.6)]
- Hypersensitivity Reactions [see Warnings and Precautions (5.7)]
- Laboratory Abnormalities [see Warnings and Precautions (5.8)]

6.1 Clinical Trials Experience

Because clinical studies are conducted under widely varying conditions, adverse reaction rates observed in the clinical studies of a drug cannot be directly compared to rates in the clinical studies of another drug and may not predict the rates observed in a broader patient population in clinical practice.

The clinical studies described in this subsection were conducted using XELJANZ tablets (referred to as “XELJANZ” in this subsection of labeling) and/or XELJANZ oral solution.

Adverse Reactions in Adults with Rheumatoid Arthritis

In RA Safety Study 1, 1,455 adults were treated with XELJANZ 5 mg twice daily, 1,456 adults were treated with 10 mg twice daily, and 1,451 adults were treated with a TNF blocker for a median of 4 years [see Clinical Studies (14.6)]. A dosage of XELJANZ 10 mg twice daily is not recommended for the treatment of RA because of increased risks [see Dosage and Administration (2.3) and Warnings and Precautions (5)]. For the treatment of adults with moderately to severely active RA [see Indications and Usage (1.1)], the recommended dosage of XELJANZ is 5 mg twice daily and the recommended dosage for XELJANZ XR is 11 mg once daily.

The safety of XELJANZ was also evaluated in two Phase 2 and five Phase 3 double-blind, placebo-controlled, multicenter trials in patients with RA. In these trials, adults were randomized to receive:

- XELJANZ (monotherapy) 5 mg twice daily (292 patients) or 10 mg twice daily (306 patients),
- In combination with DMARDs (including methotrexate), XELJANZ 5 mg twice daily (1044 patients) or 10 mg twice daily (1043 patients and
- Placebo (809 patients).

All seven trials included provisions for patients taking placebo to receive treatment with XELJANZ at Month 3 or Month 6 either by patient response (based on uncontrolled disease activity) or by design, so that adverse events cannot always be unambiguously attributed to a given treatment. Therefore, some analyses that follow include patients who changed treatment by design or by patient response from placebo to XELJANZ in both the placebo and XELJANZ group of a given interval. Comparisons between placebo and XELJANZ groups were based on the first 3 months of exposure, and comparisons between XELJANZ 5 mg twice daily and XELJANZ 10 mg twice daily were based on the first 12 months of exposure.

The long-term safety population includes all adults with RA who participated in a double-blind, placebo-controlled trial (including earlier development phase studies) and then participated in one of two long-term safety studies. The design of the long-term safety studies allowed for modification of XELJANZ doses according to clinical judgment. This limits the interpretation of the long-term safety data with respect to dose.

The most common serious adverse reactions were serious infections [see Warnings and Precautions (5.1)].

The proportion of patients who discontinued treatment due to any adverse reaction during the 0 to 3 months exposure in the double-blind, placebo-controlled trials was 4% for XELJANZ-treated patients and 3% for placebo-treated patients.

Overall Infections

In the seven placebo-controlled trials in patients with RA, during the 0 to 3 months exposure, the overall frequency of infections was 20% and 22% in the XELJANZ 5 mg twice daily and XELJANZ 10 mg twice daily groups, respectively, and 18% in the placebo group.

The most commonly reported infections with XELJANZ were upper respiratory tract infections, nasopharyngitis, and urinary tract infections (4%, 3%, and 2% of patients, respectively).

Serious Infections: In the seven placebo-controlled trials in patients with RA, during the 0 to 3 months exposure, serious infections were reported in 1 patient (0.5 events per 100 patient-years) who received placebo and 11 patients (1.7 events per 100 patient-years) who received XELJANZ 5 mg or 10 mg twice daily. The rate difference between treatment groups (and the corresponding 95% confidence interval) was 1.1 (-0.4, 2.5) events per 100 patient-years for the combined XELJANZ 5 mg twice daily and 10 mg twice daily group minus placebo.

In the seven placebo-controlled trials, during the 0 to 12 months exposure, serious infections were reported in 34 patients (2.7 events per 100 patient-years) who received XELJANZ 5 mg twice daily and 33 patients (2.7 events per 100 patient-years) who received XELJANZ 10 mg twice daily. The rate difference between XELJANZ doses (and the corresponding 95% confidence interval) was -0.1 (-1.3, 1.2) events per 100 patient-years for XELJANZ 10 mg twice daily minus XELJANZ 5 mg twice daily.

The most common serious infections included pneumonia, cellulitis, herpes zoster, and urinary tract infection [see Warnings and Precautions (5.1)].

Tuberculosis: In the seven placebo-controlled trials in patients with RA, during the 0 to 3 months exposure, tuberculosis (TB) was not reported in patients who received placebo, XELJANZ 5 mg twice daily, or XELJANZ 10 mg twice daily.

In the seven placebo-controlled trials, during the 0 to 12 months exposure, TB was reported in 0 patients who received XELJANZ 5 mg twice daily and 6 patients (0.5 events per 100 patient-years) who received XELJANZ 10 mg twice daily. The rate difference between XELJANZ doses (and the corresponding 95% confidence interval) was 0.5 (0.1, 0.9) events per 100 patient-years for XELJANZ 10 mg twice daily minus XELJANZ 5 mg twice daily.

Cases of disseminated TB were also reported. The median XELJANZ exposure prior to diagnosis of TB was 10 months (range from 152 to 960 days) [see Warnings and Precautions (5.1)].

Opportunistic Infections (excluding tuberculosis): In the seven placebo-controlled trials in patients with RA, during the 0 to 3 months exposure, opportunistic infections were not reported in patients who received placebo, XELJANZ 5 mg twice daily, or XELJANZ 10 mg twice daily.

In the seven placebo-controlled trials, during the 0 to 12 months exposure, opportunistic infections were reported in 4 patients (0.3 events per 100 patient-years) who received XELJANZ 5 mg twice daily and 4 patients (0.3 events per 100 patient-years) who received XELJANZ 10 mg twice daily. The rate difference between XELJANZ doses (and the corresponding 95% confidence interval) was 0 (-0.5, 0.5) events per 100 patient-years for XELJANZ 10 mg twice daily minus XELJANZ 5 mg twice daily.

The median XELJANZ exposure prior to diagnosis of an opportunistic infection was 8 months (range from 41 to 698 days) [see Warnings and Precautions (5.1)].

Malignancies

In the seven placebo-controlled trials in patients with RA, during the 0 to 3 months exposure, malignancies excluding NMSC were reported in 0 patients who received placebo and 2 patients (0.3 events per 100 patient-years) who received either XELJANZ 5 mg or 10 mg twice daily. The rate difference between treatment groups (and the corresponding 95% confidence interval) was 0.3 (-0.1, 0.7) events per 100 patient-years for the combined XELJANZ 5 mg and 10 mg twice daily group minus placebo.

In the seven placebo-controlled trials, during the 0 to 12 months exposure, malignancies excluding NMSC were reported in 5 patients (0.4 events per 100 patient-years) who received XELJANZ 5 mg twice daily and 7 patients (0.6 events per 100 patient-years) who received XELJANZ 10 mg twice daily. The rate difference between XELJANZ doses (and the corresponding 95% confidence interval) was 0.2 (-0.4, 0.7) events per 100 patient-years for XELJANZ 10 mg twice daily minus XELJANZ 5 mg twice daily. One of these malignancies was a case of lymphoma that occurred during the 0-to-12-month period in a patient treated with XELJANZ 10 mg twice daily.

The most common types of malignancy, including malignancies observed during the long-term extension in XELJANZ-treated patients, were lung and breast cancer, followed by gastric, colorectal, renal cell, prostate cancer, lymphoma, and malignant melanoma [see Warnings and Precautions (5.3)].

Laboratory Abnormalities

Lymphopenia: In the placebo-controlled clinical trials in patients with RA, confirmed decreases in absolute lymphocyte counts below 500 cells/mm^3 occurred in 0.04% of patients for the XELJANZ 5 mg twice daily and 10 mg twice daily groups combined during the first 3 months of exposure.

Confirmed lymphocyte counts less than 500 cells/mm^3 were associated with an increased incidence of treated and serious infections [see Warnings and Precautions (5.8)].

Neutropenia: In the placebo-controlled clinical trials in patients with RA, confirmed decreases in ANC below 1,000 cells/mm^3 occurred in 0.07% of patients for the XELJANZ 5 mg twice daily and 10 mg twice daily groups combined during the first 3 months of exposure.

There were no confirmed decreases in ANC below 500 cells/mm^3 observed in any treatment group. There was no clear relationship between neutropenia and the occurrence of serious infections.

In the long-term safety population, the pattern and incidence of confirmed decreases in ANC remained consistent with what was seen in the placebo-controlled clinical trials [see Warnings and Precautions (5.8)].

Liver Enzyme Elevations: Confirmed increases in liver enzymes greater than 3 times the upper limit of normal (3× ULN) were observed in patients with RA treated with XELJANZ. In patients experiencing liver enzyme elevation, modification of treatment regimen, such as reduction in the dose of concomitant DMARD, interruption of XELJANZ, or reduction in XELJANZ dosage, resulted in decrease or normalization of liver enzymes.

In the placebo-controlled monotherapy trials (0–3 months), no differences in the incidence of ALT or AST elevations were observed between the placebo, and XELJANZ 5 mg, and 10 mg twice daily groups.

In the placebo-controlled background DMARD trials (0–3 months), ALT elevations greater than 3× ULN were observed in 1.0%, 1.3% and 1.2% of patients who received placebo, XELJANZ 5 mg, and 10 mg twice daily, respectively. In these trials, AST elevations greater than 3× ULN were observed in 0.6%, 0.5% and 0.4% of patients who received placebo, XELJANZ 5 mg, and 10 mg twice daily, respectively.

One case of drug-induced liver injury was reported in a patient treated with XELJANZ 10 mg twice daily for approximately 2.5 months. The patient developed symptomatic elevations of AST and ALT greater than 3× ULN and bilirubin elevations greater than 2× ULN, which required hospitalizations and a liver biopsy.

Lipid Elevations: In the placebo-controlled clinical trials in patients with RA, dose-related elevations in lipid parameters (total cholesterol, LDL cholesterol, HDL cholesterol, triglycerides) were observed at one month of exposure and remained stable thereafter. Changes in lipid parameters during the first 3 months of exposure in the placebo-controlled clinical trials are summarized below:

- Mean LDL cholesterol increased by 15% in the XELJANZ 5 mg twice daily arm and 19% in the XELJANZ 10 mg twice daily arm.
- Mean HDL cholesterol increased by 10% in the XELJANZ 5 mg twice daily arm and 12% in the XELJANZ 10 mg twice daily arm.
- Mean LDL/HDL ratios were essentially unchanged in XELJANZ-treated patients.

In a placebo-controlled clinical trial, elevations in LDL cholesterol and ApoB decreased to pretreatment levels in response to statin therapy.

In the long-term safety population, elevations in lipid parameters remained consistent with what was seen in the placebo-controlled clinical trials.

Serum Creatinine Elevations: In the placebo-controlled clinical trials in patients with RA, dose-related elevations in serum creatinine were observed with XELJANZ treatment. The mean increase in serum creatinine was <0.1 mg/dL in the 12-month pooled safety analysis; however, with increasing duration of exposure in the long-term extensions, up to 2% of patients were discontinued from XELJANZ treatment due to the protocol-specified discontinuation criterion of an increase in creatinine by more than 50% of baseline. The clinical significance of the observed serum creatinine elevations is unknown.

Common Adverse Reactions

Table 5 displays adverse reactions that occurred in 2% or more of patients on XELJANZ 5 mg or 10 mg twice daily and at least 1% greater than in XELJANZ-treated patients that observed in placebo-treated patients with or without DMARD in the RA trials.

Table 5: Common Adverse Reactions [reported in ≥2% of patients treated with either dose of XELJANZ and ≥1% greater than that reported for placebo.] in Clinical Trials of XELJANZ for the Treatment of Rheumatoid Arthritis in Adults With or Without Concomitant DMARDs (0–3 Months)
Preferred Term | Placebo | XELJANZ 5 mg Twice Daily | XELJANZ 10 mg Twice Daily [The recommended dose of XELJANZ for the treatment of RA is 5 mg twice daily [see Dosage and Administration (2)].]
Preferred Term | N = 809 (%) | N = 1336 (%) | N = 1349 (%)
Upper respiratory tract infection | 3 | 4 | 4
Nasopharyngitis | 3 | 4 | 3
Diarrhea | 2 | 4 | 3
Headache | 2 | 4 | 3
Hypertension | 1 | 2 | 2
N reflects randomized and treated patients from the seven placebo-controlled clinical trials.

Other adverse reactions that occurred in placebo-controlled and open-label extension studies in patients with RA included:

Blood and lymphatic system disorders: Anemia

Infections and infestations: Diverticulitis

Metabolism and nutrition disorders: Dehydration

Psychiatric disorders: Insomnia

Nervous system disorders: Paresthesia

Respiratory, thoracic and mediastinal disorders: Dyspnea, cough, sinus congestion, interstitial lung disease (cases were limited to patients with RA and some were fatal)

Gastrointestinal disorders: Abdominal pain, dyspepsia, vomiting, gastritis, nausea

Hepatobiliary disorders: Hepatic steatosis

Skin and subcutaneous tissue disorders: Rash, erythema, pruritus

Musculoskeletal, connective tissue and bone disorders: Musculoskeletal pain, arthralgia, tendonitis, joint swelling

Neoplasms benign, malignant and unspecified (including cysts and polyps): Non-melanoma skin cancers

General disorders and administration site conditions: Pyrexia, fatigue, peripheral edema

Clinical Experience in Methotrexate-Naïve Patients

Study RA-VI was an active-controlled clinical trial in methotrexate-naïve patients [see Clinical Studies (14)]. The safety experience in these patients was consistent with Studies RA-I through V.

Adverse Reactions in Adults with Psoriatic Arthritis

The safety of XELJANZ was evaluated in 2 double-blind Phase 3 clinical trials in adults with active psoriatic arthritis (PsA):

- Study PsA-I (NCT01877668) had a duration of 12 months and enrolled adults who had an inadequate response to a nonbiologic DMARD and who were naïve to treatment with a TNF blocker. Study PsA-I included a 3-month placebo-controlled period and also included adalimumab 40 mg subcutaneously once every 2 weeks for 12 months.
- Study PsA-II (NCT01882439) had a duration of 6 months and enrolled adults who had an inadequate response to at least one approved TNF blocker. This clinical trial included a 3-month placebo-controlled period.

In these combined Phase 3 clinical trials, 238 patients were randomized and treated with XELJANZ 5 mg twice daily and 236 patients were randomized and treated with XELJANZ 10 mg twice daily. A dosage of XELJANZ 10 mg twice daily is not recommended for the treatment of PsA. For the treatment of adults with active PsA [see Indications and Usage (1.2)], the recommended dosage of XELJANZ is 5 mg twice daily and the recommended dosage for XELJANZ XR is 11 mg once daily [see Dosage and Administration (2.3)].

All patients in the clinical trials in patients with PsA were required to receive treatment with a stable dose of a nonbiologic DMARD [the majority (79%) received methotrexate]. The study population randomized and treated with XELJANZ (474 patients) included 45 (10%) patients aged 65 years or older and 66 (14%) patients with diabetes at baseline.

During the 2 PsA controlled clinical trials, there were:

- 3 malignancies (excluding NMSC) in 474 patients who received XELJANZ plus non-biologic DMARD (6 to 12 months exposure)
- 0 malignancies in 236 patients who received placebo plus non-biologic DMARD group (3 months exposure) and
- 0 malignancies in 106 patients in patients who received adalimumab plus non-biologic DMARD group (12 months exposure).

No lymphomas were reported. Malignancies have also been observed in the long-term extension study in patients with PsA treated with XELJANZ.

The safety profile observed in adults with active PsA treated with XELJANZ was consistent with the safety profile observed in adults with RA.

Adverse Reactions in Adults with Ankylosing Spondylitis

The safety of XELJANZ was evaluated in adults with active ankylosing spondylitis (AS) in a double-blind placebo-controlled Phase 3 clinical trial (Study AS-I) and in a dose-ranging Phase 2 clinical trial (Study AS-II).

- Study AS-I (NCT03502616) had a duration of 48 weeks and enrolled adults who had an inadequate response to at least 2 NSAIDs. Study AS-I included a 16-week double-blind period in which patients received XELJANZ 5 mg or placebo twice daily and a 32-week open-label treatment period in which all patients received XELJANZ 5 mg twice daily.
- Study AS-II (NCT01786668) had a duration of 16 weeks and enrolled adults who had an inadequate response to at least 2 NSAIDs. This clinical trial included a 12-week treatment period in which patients received either XELJANZ 2 mg (40% of the recommended dose), 5 mg, 10 mg, or placebo twice daily. A dosage of XELJANZ 10 mg twice daily is not recommended for the treatment of AS. For the treatment of adults with active AS [see Indications and Usage (1.3)], the recommended dosage of XELJANZ is 5 mg twice daily and the recommended dosage for XELJANZ XR is 11 mg once daily [see Dosage and Administration (2.3)].

In the combined Phase 2 and Phase 3 clinical trials, a total of 420 patients were treated with either XELJANZ 2 mg, 5 mg, or 10 mg twice daily. Of these, 316 patients were treated with XELJANZ 5 mg twice daily for up to 48 weeks. In the combined double-blind period, 185 patients were randomized to and treated with XELJANZ 5 mg twice daily and 187 to placebo for up to 16 weeks. Concomitant treatment with stable doses of nonbiologic DMARDs, NSAIDs, or corticosteroids (≤10 mg/day) was permitted. The study population randomized and treated with XELJANZ included 13 (3%) patients aged 65 years or older and 18 (4%) patients with diabetes at baseline.

The safety profile observed in adults with AS treated with XELJANZ was consistent with the safety profile observed in adults with RA and PsA.

Adverse Reactions in Pediatric Patients 2 Years of Age and Older with Polyarticular Course Juvenile Idiopathic Arthritis

XELJANZ tablets and XELJANZ oral solution 5 mg twice daily or weight-based equivalent twice daily was studied in 225 pediatric patients from 2 years to 17 years of age in Study pcJIA-I [see Clinical Studies (14.4)] and one open-label extension study (Study A3921145). The total patient exposure (defined as patients who received at least one dose of XELJANZ tablets or XELJANZ oral solution) was 105.6 patient-years in Study pcJIA-I and 777.5 patient-years in Study A3921145.

In general, the types of adverse reactions in pediatric patients 2 years of age and older with pcJIA, were consistent with those seen in adults with RA and PsA (see Adverse Reactions in Adults with Rheumatoid Arthritis and Adverse Reactions in Adults with Psoriatic Arthritis).

Adverse Reactions in Adults with Ulcerative Colitis

The safety of XELJANZ has been evaluated in adults with moderately to severely active UC in 4 randomized, double-blind, placebo-controlled trials (UC-I, UC-II, UC-III, and dose-ranging UC-V) and an open-label long-term extension study (UC-IV) [see Clinical Studies (14.5)].

Adverse reactions reported in ≥5% of patients treated with either XELJANZ 5 mg or 10 mg twice daily and ≥1% greater than reported in patients receiving placebo in either the induction or maintenance clinical trials of patients with UC were: nasopharyngitis, elevated cholesterol levels, headache, upper respiratory tract infection, increased blood creatine phosphokinase, rash, diarrhea, and herpes zoster.

Induction Trials in Adults with UC

Common adverse reactions reported in ≥2% of patients treated with XELJANZ 10 mg twice daily and ≥1% greater in XELJANZ-treated patients than placebo-treated patients in the 3 induction trials of patients with UC (Studies UC-I, UC-II, and UC-V) were: headache, nasopharyngitis, elevated cholesterol levels, acne, increased blood creatine phosphokinase, and pyrexia.

Maintenance Trial in Adults with UC

Common adverse reactions reported in ≥4% of patients treated with either dosage of XELJANZ and ≥1% greater than reported in patients treated with placebo in the maintenance trial of patients with UC (Study UC-III) are shown in Table 6.

Table 6: Common Adverse Reactions [Reported in ≥4% of patients treated with either XELJANZ dosage and ≥1% greater in XELJANZ-treated patients than placebo-treated patients.] in Adults with UC During the 52-Week Maintenance Trial (Study UC-III)
Preferred Term | Placebo | XELJANZ; 5 mg Twice Daily | XELJANZ; 10 mg Twice Daily
Preferred Term | N = 198; (%) | N = 198; (%) | N = 196; (%)
Nasopharyngitis | 6 | 10 | 14
Elevated cholesterol levels [Includes hypercholesterolemia, hyperlipidemia, blood cholesterol increased, dyslipidemia, blood triglycerides increased, low-density lipoprotein increased, low-density lipoprotein abnormal, or lipids increased.] | 1 | 5 | 9
Headache | 6 | 9 | 3
Upper respiratory tract infection | 4 | 7 | 6
Increased blood creatine phosphokinase | 2 | 3 | 7
Rash | 4 | 3 | 6
Diarrhea | 3 | 2 | 5
Herpes zoster | 1 | 1 | 5
Gastroenteritis | 3 | 3 | 4
Anemia | 2 | 4 | 2
Nausea | 3 | 1 | 4

Dose-dependent adverse reactions seen in patients treated with XELJANZ 10 mg twice daily, in comparison to 5 mg twice daily, include the following: herpes zoster infections, serious infections, and NMSC [see Warnings and Precautions (5.1, 5.3)].

During the UC controlled clinical studies (8-week induction and 52-week maintenance studies), which included 1,220 patients, 0 cases of solid cancer or lymphoma were observed in XELJANZ-treated patients.

In the long-term extension study, malignancies (including solid cancers, lymphomas and NMSC) were observed in patients treated with XELJANZ 5 mg and 10 mg twice daily [see Warnings and Precautions (5.3)]. Five cases of pulmonary embolism were reported in patients taking XELJANZ 10 mg twice daily, including one fatality in a patient with advanced cancer [see Warnings and Precautions (5.5)].

6.2 Postmarketing Experience

The following adverse reactions have been identified during post-approval use of XELJANZ (tablets and oral solution) and XELJANZ XR (extended-release tablets). Because these reactions are reported voluntarily from a population of uncertain size, it is not always possible to reliably estimate their frequency or establish a causal relationship to drug exposure.

Immune system disorders: Drug hypersensitivity (events such as angioedema and urticaria have been observed)

Skin and subcutaneous tissue disorders: Acne

7 DRUG INTERACTIONS

Table 7 includes drugs with clinically significant drug interactions when concomitantly used with XELJANZ (tablets and oral solution) and XELJANZ XR (extended-release tablets) and instructions for preventing or managing them.

Table 7: Clinically Significant Interactions Affecting XELJANZ/XELJANZ XR When Concomitantly Used with Other Drugs
Strong CYP3A4 Inhibitors (e.g., ketoconazole)
Clinical Impact | Increased exposure to tofacitinib
Intervention | Dosage modification of XELJANZ/XELJANZ XR is recommended [see Dosage and Administration (2), Clinical Pharmacology, Figure 3 (12.3)]
Moderate CYP3A4 Inhibitors Concomitantly Used with Strong CYP2C19 Inhibitors (e.g., fluconazole)
Clinical Impact | Increased exposure to tofacitinib
Intervention | Dosage modification of XELJANZ/XELJANZ XR is recommended [see Dosage and Administration (2), Clinical Pharmacology, Figure 3 (12.3)]
Strong CYP3A4 Inducers (e.g., rifampin)
Clinical Impact | Decreased exposure to tofacitinib and may result in loss of or reduced clinical response
Intervention | Concomitant use with XELJANZ/XELJANZ XR is not recommended [see Clinical Pharmacology, Figure 3 (12.3)]
Immunosuppressive Drugs (e.g., azathioprine, tacrolimus, cyclosporine)
Clinical Impact | Risk of added immunosuppression; concomitant use of XELJANZ/XELJANZ XR with biologic DMARDs or potent immunosuppressants has not been studied in patients with RA, PsA, AS, UC, or pcJIA.
Intervention | Concomitant use with XELJANZ/XELJANZ XR is not recommended [see Indications and Usage (1), Clinical Pharmacology, Figure 3 (12.3)]

8 USE IN SPECIFIC POPULATIONS

8.1 Pregnancy

Risk Summary

The available data with XELJANZ (tablets and oral solution) and XELJANZ XR (extended-release tablets) from a pregnancy exposure registry that enrolled 11 exposed pregnant females, pharmacovigilance, and published literature are insufficient to draw conclusions about a drug‑associated risk of major birth defects, miscarriage, or other adverse maternal or fetal outcomes. There are risks to the mother and the fetus associated with RA and UC in pregnancy (see Clinical Considerations). In animal reproduction studies, fetocidal and teratogenic effects were noted when pregnant rats and rabbits received tofacitinib during the period of organogenesis at exposures multiples of 73-times and 6.3-times the maximum recommended dose of 10 mg twice daily, respectively. Further, in a peri- and post-natal study in rats, tofacitinib resulted in reductions in live litter size, postnatal survival, and pup body weights at exposure multiples of approximately 73-times the recommended dosage of 5 mg twice daily and approximately 36 times the maximum recommended dosage of 10 mg twice daily, respectively (see Data).

The background risks of major birth defects and miscarriage for the indicated populations are unknown. All pregnancies have a background risk of birth defect, loss, or other adverse outcomes. The background risks in the U.S. general population of major birth defects and miscarriages are 2 to 4% and 15 to 20% of clinically recognized pregnancies, respectively.

Clinical Considerations

Disease-Associated Maternal and/or Embryo/Fetal Risk: Published data suggest that increased disease activity is associated with the risk of developing adverse pregnancy outcomes in women with RA or UC. Adverse pregnancy outcomes include preterm delivery (before 37 weeks of gestation), low birth weight (less than 2500 grams) infants, and small for gestational age at birth.

Data

Animal Data: In a rat embryofetal developmental study, in which pregnant rats received tofacitinib during organogenesis, tofacitinib was teratogenic at exposure levels approximately 146 times the recommended dose of 5 mg twice daily, and approximately 73 times the maximum recommended dose of 10 mg twice daily (on an AUC basis at oral doses of 100 mg/kg/day in rats). Teratogenic effects consisted of external and soft tissue malformations of anasarca and membranous ventricular septal defects, respectively; and skeletal malformations or variations (absent cervical arch; bent femur, fibula, humerus, radius, scapula, tibia, and ulna; sternoschisis; absent rib; misshapen femur; branched rib; fused rib; fused sternebra; and hemicentric thoracic centrum). In addition, there was an increase in post-implantation loss, consisting of early and late resorptions, resulting in a reduced number of viable fetuses. Mean fetal body weight was reduced. No developmental toxicity was observed in rats at exposure levels approximately 58 times the recommended dose of 5 mg twice daily, and approximately 29 times the maximum recommended dose of 10 mg twice daily (on an AUC basis at oral doses of 30 mg/kg/day in pregnant rats).

In a rabbit embryofetal developmental study in which pregnant rabbits received tofacitinib during the period of organogenesis, tofacitinib was teratogenic at exposure levels approximately 13 times the recommended dose of 5 mg twice daily, and approximately 6.3 times the maximum recommended dose of 10 mg twice daily (on an AUC basis at oral doses of 30 mg/kg/day in rabbits) in the absence of signs of maternal toxicity. Teratogenic effects included thoracogastroschisis, omphalocele, membranous ventricular septal defects, and cranial/skeletal malformations (microstomia, microphthalmia), mid-line and tail defects. In addition, there was an increase in post-implantation loss associated with late resorptions. No developmental toxicity was observed in rabbits at exposure levels approximately 3 times the recommended dose of 5 mg twice daily, and approximately 1.5 times the maximum recommended dose of 10 mg twice daily (on an AUC basis at oral doses of 10 mg/kg/day in pregnant rabbits).

In a peri- and postnatal development study in pregnant rats that received tofacitinib from gestation day 6 through day 20 of lactation, there were reductions in live litter size, postnatal survival, and pup body weights at exposure levels approximately 73 times the recommended dose of 5 mg twice daily, and approximately 36 times the maximum recommended dose of 10 mg twice daily (on an AUC basis at oral doses of 50 mg/kg/day in rats). There was no effect on behavioral and learning assessments, sexual maturation or the ability of the F1 generation rats to mate and produce viable F2 generation fetuses in rats at exposure levels approximately 17 times the recommended dose of 5 mg twice daily, and approximately 8.3 times the maximum recommended dose of 10 mg twice daily (on an AUC basis at oral doses of 10 mg/kg/day in rats).

8.2 Lactation

Risk Summary

Based on published data, tofacitinib is present in human milk. Data on the effects of tofacitinib on the breastfed infant is limited to a small number of cases with no reported adverse effects. There are no data on the effects on milk production. Given the serious adverse reactions seen in patients treated with XELJANZ (tablets and oral solution) and XELJANZ XR (extended-release tablets), such as increased risk of serious infections, advise patients that breastfeeding is not recommended during treatment and for at least 18 hours after the last dose of XELJANZ or 36 hours after the last dose of XELJANZ XR (approximately 6 elimination half-lives).

Data

Following administration of tofacitinib to lactating rats, concentrations of tofacitinib in milk over time paralleled those in serum and were approximately 2 times higher in milk relative to maternal serum at all time points measured.

8.3 Females and Males of Reproductive Potential

Contraception

Females

In an animal reproduction study, tofacitinib at AUC multiples of 13 times the recommended dosage of 5 mg twice daily and 6.3 times the maximum recommended dosage of 10 mg twice daily demonstrated adverse embryo-fetal findings [see Use in Specific Populations (8.1)]. However, there is uncertainty as to how these animal findings relate to females of reproductive potential treated with the recommended clinical dosage. Consider pregnancy planning and prevention for females of reproductive potential.

Infertility

Females

Based on findings in rats, treatment with XELJANZ (tablets and oral solution) and XELJANZ XR (extended-release tablets) may result in reduced fertility in females of reproductive potential. It is not known if this effect is reversible [see Nonclinical Toxicology (13.1)].

8.4 Pediatric Use

The safety and effectiveness of XELJANZ (tablets and oral solution) in pediatric patients for indications, other than in patients with active pcJIA and PsA, have not been established.

The safety and effectiveness of XELJANZ have not been established in pediatric patients less than 2 years of age.

The safety and effectiveness of XELJANZ XR (extended-release tablets) in pediatric patients have not been established.

Polyarticular Course Juvenile Idiopathic Arthritis (pcJIA)

The safety and effectiveness of XELJANZ (tablets and oral solution) for the treatment of active pcJIA have been established in pediatric patients 2 years of age and older who have had an inadequate response or intolerance to one or more TNF blockers.

Use of XELJANZ for this indication is supported by evidence from adequate and well-controlled studies of XELJANZ tablets in adults with RA, pharmacokinetic (PK) data from adult patients with RA, and with additional safety, efficacy, and PK data from a clinical trial of XELJANZ in pediatric patients 2 years and older with active pcJIA (Study pcJIA-I) [see Adverse Reactions (6.1), Clinical Pharmacology (12.3), and Clinical Studies (14.1, 14.4)].

Adverse reactions observed in pediatric patients with pcJIA who received XELJANZ were consistent with those reported in adults with RA [see Adverse Reactions (6.1)].

Psoriatic Arthritis

The safety and effectiveness of XELJANZ (tablets and oral solution) for the treatment of active PsA have been established in pediatric patients 2 years of age and older who have had an inadequate response or intolerance to one or more TNF blockers.

Use of XELJANZ for this indication is supported by evidence from well-controlled studies of XELJANZ tablets in adults with PsA, PK data from adults with PsA, and PK data from a clinical trial of XELJANZ in 225 pediatric patients with JIA, and safety data from 280 pediatric patients 2 years of age and older with JIA [see Adverse Reactions (6.1), Clinical Pharmacology (12.3), and Clinical Studies (14.2)]. Following administration of the recommended XELJANZ dosage in pediatric patients 2 years of age and older with PsA, tofacitinib plasma exposures are predicted to be comparable to those observed in adults with PsA based on population PK modeling and simulation [see Clinical Pharmacology (12.3)].

Systemic Juvenile Idiopathic Arthritis

The safety and effectiveness of XELJANZ for the treatment of pediatric patients with systemic juvenile idiopathic arthritis (sJIA) have not been established.

The results from a two-part study (an open-label, run-in phase, followed by a double-blind, placebo-controlled, randomized event-driven withdrawal phase) in 100 patients 2 years to 17 years of age with sJIA with active systemic features did not demonstrate that XELJANZ (dosed at 5 mg twice daily or body weight-based equivalent twice daily) was efficacious in the treatment of sJIA with active systemic features.

Of the 100 patients enrolled in the open-label run-in phase, 59 (59%) patients achieved a clinical response and were eligible for the double-blind withdrawal phase. There were 28 patients randomized to XELJANZ and 31 patients to placebo. The study data were insufficient to demonstrate efficacy and, therefore, XELJANZ is not recommended for the treatment of sJIA.

Adverse reactions observed in pediatric patients with sJIA receiving XELJANZ/XELJANZ oral solution were consistent with those reported in pcJIA and RA patients [see Adverse Reactions (6.1)].

8.5 Geriatric Use

Of the 3315 adults who were enrolled in clinical trials with RA (Studies RA-I to V), a total of 505 patients were 65 years of age and older, including 71 patients 75 years and older. The frequency of serious infection among XELJANZ tablets-treated patients 65 years of age and older was higher than among those adults under the age of 65.

Of the 1156 XELJANZ tablet-treated patients in clinical trials of patients with UC, a total of 77 patients (7%) were 65 years of age or older. Clinical studies of XELJANZ in patients with UC did not include sufficient numbers of patients aged 65 years and older to determine whether they respond differently from younger adult patients.

Of the 783 XELJANZ tablet-treated patients in clinical trials of patients with PsA, a total of 72 (9.2%) patients were 65 years of age and older, including 2 (0.3%) patients 75 years and older. These clinical studies did not include sufficient numbers of patients aged 65 years and older with PsA to determine if they respond differently from younger adult patients.

Of the 420 XELJANZ tablet-treated patients in clinical trials of patients with AS, a total of 12 (2.9%) patients were 65 years of age and older, including 1 (0.2%) patient 75 years and older. These clinical studies did not include sufficient numbers of patients aged 65 years and older with AS to determine if they respond differently from younger adult patients.

8.6 Renal Impairment

Moderate and Severe Renal Impairment

XELJANZ-treated patients with moderate renal impairment (RI) (CLcr ≥30 and ≤50 mL/minute) or severe RI (<30 mL/minute) had greater tofacitinib blood concentrations than XELJANZ-treated patients with normal renal function (CLcr >80 mL/minute). The recommended dosage of XELJANZ (tablets and oral solution) and XELJANZ XR (extended-release tablets) in patients with moderate or severe RI (including those with severe RI who are undergoing hemodialysis) is lower than the recommended dosage in patients with normal renal function [see Dosage and Administration (2.3, 2.4, 2.5)].

Mild Renal Impairment

The recommended dosage in patients with mild RI (CLcr >50 and ≤80 mL/minute) is the same as patients with normal renal function.

8.7 Hepatic Impairment

Severe Hepatic Impairment

XELJANZ (tablets and oral solution) and XELJANZ XR (extended-release tablets) has not been studied in patients with severe hepatic impairment (HI) (Child-Pugh C); therefore, use of XELJANZ/XELJANZ XR in patients with severe HI is not recommended.

Moderate Hepatic Impairment

XELJANZ-treated patients with moderate hepatic impairment (Child-Pugh B) had greater tofacitinib blood concentration than XELJANZ-treated patients with normal hepatic function [see Clinical Pharmacology (12.3)]. Higher blood concentrations may increase the risk of some adverse reactions. The recommended XELJANZ (tablets and oral solution) and XELJANZ XR (extended-release tablets) dosage in patients with moderate HI is lower than the recommended dosage in patients with normal hepatic function [see Dosage and Administration (2.3, 2.4, 2.5)].

Mild Hepatic Impairment

The recommended dosage of XELJANZ/XELJANZ XR in patients with mild hepatic impairment (Child-Pugh A) is the same as patients with normal hepatic function.

Hepatitis B or C Serology

The safety and efficacy of XELJANZ/XELJANZ XR have not been studied in patients with positive hepatitis B virus or hepatitis C virus serology.

10 OVERDOSAGE

There is no specific antidote for overdose with XELJANZ (tablets and oral solution) and XELJANZ XR (extended-release tablets). In case of an overdose, it is recommended that the patient be monitored for signs and symptoms of adverse reactions.

In a study in patients with end-stage renal disease (ESRD) undergoing hemodialysis, plasma tofacitinib concentrations declined more rapidly during the period of hemodialysis and dialyzer efficiency, calculated as dialyzer clearance/blood flow entering the dialyzer, was high [mean (SD) = 0.73 (0.15)]. However, due to the significant non-renal clearance of tofacitinib, the fraction of total elimination occurring by hemodialysis was small, and thus, limits the value of hemodialysis for treatment of overdose with XELJANZ/XELJANZ XR.

Consider contacting the Poison Help line (1-800-222-1222) or a medical toxicologist for additional overdose management recommendations.

11 DESCRIPTION

XELJANZ (tofacitinib) tablets, XELJANZ XR (tofacitinib) extended-release tablets and XELJANZ (tofacitinib) oral solution are formulated with the citrate salt of tofacitinib, a JAK inhibitor.

Tofacitinib citrate is a white to off-white powder with the following chemical name: (3R,4R)-4-methyl-3-(methyl-7H-pyrrolo [2,3-d]pyrimidin-4-ylamino)-ß-oxo-1-piperidinepropanenitrile, 2-hydroxy-1,2,3-propanetricarboxylate (1:1).

The solubility of tofacitinib citrate in water is 2.9 mg/mL.

Tofacitinib citrate has a molecular weight of 504.5 Daltons (or 312.4 Daltons as the tofacitinib free base) and a molecular formula of C16H20N6O•C6H8O7. The chemical structure of tofacitinib citrate is:

XELJANZ tablets is supplied for oral administration as a:

- 5 mg white round, immediate-release film-coated tablet. Each tablet contains 5 mg of tofacitinib (equivalent to 8.08 mg of tofacitinib citrate) and the following inactive ingredients: croscarmellose sodium, HPMC 2910/Hypromellose 6cP, lactose monohydrate, macrogol/PEG3350, magnesium stearate, microcrystalline cellulose, titanium dioxide, and triacetin.
- 10 mg blue round, immediate-release film-coated tablet. Each tablet contains 10 mg of tofacitinib (equivalent to 16.16 mg of tofacitinib citrate) and the following inactive ingredients: croscarmellose sodium, FD&C Blue #1/Brilliant Blue FCF Aluminum Lake, FD&C Blue #2/Indigo Carmine Aluminum Lake, HPMC 2910/Hypromellose 6cP, lactose monohydrate, macrogol/PEG3350, magnesium stearate, microcrystalline cellulose, titanium dioxide, and triacetin.

XELJANZ XR is supplied for oral administration as a:

- 11 mg pink, oval, extended-release film-coated tablet with a drilled hole at one end of the tablet band. Each tablet contains 11 mg of tofacitinib (equivalent to 17.77 mg tofacitinib citrate) and the following inactive ingredients: cellulose acetate, copovidone, hydroxyethyl cellulose, hydroxypropyl cellulose, HPMC 2910/Hypromellose, magnesium stearate, red iron oxide, sorbitol, titanium dioxide and triacetin. Printing ink contains, ammonium hydroxide, ferrosoferric oxide/black iron oxide, propylene glycol, and shellac glaze.
- 22 mg beige, oval, extended-release film-coated tablet with a drilled hole at one end of the tablet band. Each tablet contains 22 mg of tofacitinib (equivalent to 35.54 mg tofacitinib citrate) and the following inactive ingredients: cellulose acetate, copovidone, FD&C Blue #2 Aluminum Lake, hydroxyethyl cellulose, hydroxypropyl cellulose, HPMC 2910/Hypromellose, magnesium stearate, red iron oxide, sorbitol, titanium dioxide, triacetin, and yellow iron oxide. Printing ink contains ammonium hydroxide, ferrosoferric oxide/black iron oxide, propylene glycol, and shellac glaze.

XELJANZ oral solution is supplied for oral administration as a 1 mg/mL clear, colorless solution. Each 1 mL contains 1 mg of tofacitinib (equivalent to 1.62 mg of tofacitinib citrate) and the following inactive ingredients: grape flavor (natural), hydrochloric acid, lactic acid, purified water, sodium benzoate, sucralose, and xylitol.

12 CLINICAL PHARMACOLOGY

12.1 Mechanism of Action

Tofacitinib is a Janus kinase (JAK) inhibitor. JAKs are intracellular enzymes which transmit signals arising from cytokine or growth factor-receptor interactions on the cellular membrane to influence cellular processes of hematopoiesis and immune cell function. Within the signaling pathway, JAKs phosphorylate and activate Signal Transducers and Activators of Transcription (STATs) which modulate intracellular activity including gene expression. Tofacitinib modulates the signaling pathway at the point of JAKs, preventing the phosphorylation and activation of STATs. JAK enzymes transmit cytokine signaling through pairing of JAKs (e.g., JAK1/JAK3, JAK1/JAK2, JAK1/TyK2, JAK2/JAK2). Tofacitinib inhibited the in vitro activities of JAK1/JAK2, JAK1/JAK3, and JAK2/JAK2 combinations with IC50 of 406, 56, and 1377 nM, respectively. However, the relevance of specific JAK combinations to therapeutic effectiveness is not known.

12.2 Pharmacodynamics

Treatment with XELJANZ was associated with dose-dependent reductions of circulating CD16/56+ natural killer cells, with estimated maximum reductions occurring at approximately 8-10 weeks after initiation of therapy. These changes generally resolved within 2-6 weeks after discontinuation of treatment. Treatment with XELJANZ was associated with dose-dependent increases in B cell counts. Changes in circulating T-lymphocyte counts and T-lymphocyte subsets (CD3+, CD4+ and CD8+) were small and inconsistent. The clinical significance of these changes is unknown.

Total serum IgG, IgM, and IgA levels after 6-month dosing in patients with rheumatoid arthritis (RA) were lower than in patients who received placebo; however, changes were small and not dose-dependent.

After treatment with XELJANZ in patients with RA, rapid decreases in serum C-reactive protein (CRP) were observed and maintained throughout dosing. Changes in CRP observed with XELJANZ treatment do not reverse fully within 2 weeks after discontinuation, indicating a longer duration of pharmacodynamic activity compared to the pharmacokinetic half-life.

Similar changes in T cells, B cells, and serum CRP have been observed in patients with active psoriatic arthritis (PsA) although reversibility was not assessed. Total serum immunoglobulins were not assessed in patients with active PsA.

12.3 Pharmacokinetics

Following oral administration of XELJANZ (tablets and oral solution), peak plasma concentrations were reached within 0.5 hour - 1 hour, elimination half-life was about 3 hours and a dose-proportional increase in systemic exposure was observed in the therapeutic dosage range. Steady state concentrations were achieved in 24-48 hours with negligible accumulation after twice daily administration.

Following oral administration of XELJANZ XR (extended-release tablets), peak plasma concentrations were reached at 4 hours and half-life was about 6 to 8 hours. Steady state concentrations were achieved within 48 hours with negligible accumulation after once daily administration.

Table 8 describes the pharmacokinetic parameters of XELJANZ and XELJANZ XR.

Table 8: Pharmacokinetic Parameters of XELJANZ/XELJANZ XR Following Multiple Oral Dosing
PK Parameters [Values represent the geometric mean, except Tmax, for which is the median (range) is shown.] (CV%) | XELJANZ |  | XELJANZ XR
Dosing Regimen | 5 mg Twice Daily | 10 mg Twice Daily | 11 mg Once Daily | 22 mg Once Daily
AUC24 (ng.hr/mL) | 263.4 (15) | 539.6 (22) | 269.0 (18) | 596.6 (19)
Cmax (ng/mL) | 42.7 (26) | 84.7 (18) | 38.2 (15) | 83.8 (25)
Cmin (ng/mL) | 1.41 (40) | 3.10 (54) | 1.07 (69) | 3.11 (43)
Tmax (hours) | 1.0 (0.5 to14.0 [Values beyond 12 hours were after the evening dose which was administered 12 hours after the morning dose of twice-daily XELJANZ.]) | 0.8 (0.5 to 14.0) | 4.0 (3.0 to 4.0) | 4.0 (2.0 to 4.0)
Abbreviations: AUC24 = area under the concentration time profile from time 0 to 24 hours; Cmax = maximum plasma concentration; Cmin = minimum plasma concentration; Tmax = time to Cmax; CV = Coefficient of variation.

Absorption

XELJANZ

The absolute oral bioavailability of XELJANZ is 74%. Coadministration of XELJANZ with a high-fat meal resulted in no changes in AUC while Cmax was reduced by 32%. In clinical trials, XELJANZ was administered without regard to meals [see Dosage and Administration (2.2)].

XELJANZ XR

Coadministration of XELJANZ XR 11 and 22 mg with a high-fat meal resulted in no changes in AUC while Cmax was increased by 27% and 19% respectively. Tmax was extended by approximately 1 hour for both XELJANZ XR 11 and 22 mg.

Distribution

After intravenous administration, the volume of distribution was 87 L. The protein binding of tofacitinib is approximately 40%. Tofacitinib binds predominantly to albumin and does not appear to bind to α1-acid glycoprotein. Tofacitinib distributes equally between red blood cells and plasma.

Metabolism and Excretion

Clearance mechanisms for tofacitinib are approximately 70% hepatic metabolism and 30% renal excretion of the parent drug. The metabolism of tofacitinib is primarily mediated by CYP3A4 with minor contribution from CYP2C19. In a human radiolabeled study, more than 65% of the total circulating radioactivity was accounted for by unchanged tofacitinib, with the remaining 35% attributed to 8 metabolites, each accounting for less than 8% of total radioactivity. The pharmacologic activity of tofacitinib is attributed to the parent molecule.

Pharmacokinetics in Patients with RA, PsA, AS, and UC

Population pharmacokinetic (PK) analyses indicated that PK characteristics were similar between patients with RA, PsA, ankylosing spondylitis, and UC. The coefficient of variation (%) in AUC of tofacitinib were generally similar across different disease patients, ranging from 22% to 34% (Table 9).

Table 9: Tofacitinib Exposure in Patients with RA, PsA, AS, and UC After Administration of XELJANZ 5 mg Twice Daily or 10 mg Twice Daily
Pharmacokinetic Parameters [Pharmacokinetic parameters estimated based on population pharmacokinetic analysis.] Geometric Mean (CV%) | XELJANZ 5 mg Twice Daily |  |  |  | XELJANZ 10 mg Twice Daily
Pharmacokinetic Parameters [Pharmacokinetic parameters estimated based on population pharmacokinetic analysis.] Geometric Mean (CV%) | Rheumatoid Arthritis | Psoriatic Arthritis | Ankylosing Spondylitis | Ulcerative Colitis | Ulcerative Colitis
AUC0–24,ss (ng∙h/mL) | 504 (22.0%) | 419 (34.1%) | 381 (25.4%) | 423 (22.6%) | 807 (24.6%)
Abbreviations: AUC0–24,ss = area under the plasma concentration-time curve over 24 hours at steady state; CV = coefficient of variation.

Specific Populations

Covariate evaluation as part of population PK analyses in adult patient populations indicated no clinically relevant change in tofacitinib exposure, after accounting for differences in renal function (i.e., creatinine clearance) between patients, based on age, weight, biological sex and race (Figure 1). An approximately linear relationship between body weight and volume of distribution was observed, resulting in higher peak (Cmax) and lower trough (Cmin) concentrations in lighter patients. However, this difference is not considered to be clinically relevant.

Covariate evaluation as part of population PK analyses in pediatric patients with pcJIA, including PsA, identified body weight significantly impacting tofacitinib exposure, which supports weight-based dosing in this population. There were no identified clinically significant differences in tofacitinib exposure with different age, biological sex, racial, or pcJIA or PsA disease severity groups.

The effect of renal and hepatic impairment and other intrinsic factors on the PK of tofacitinib is shown in Figure 1.

Figure 1: Impact of Intrinsic Factors on Tofacitinib Pharmacokinetics

Note: Reference values for weight, age, biological sex, and race comparisons are 70 kg, 55 years, male, and white, respectively; reference groups for renal and hepatic impairment data are patients with normal renal and hepatic function. Renal function was estimated using creatinine clearance by Cockcroft-Gault method and hepatic function was estimated using Child-Pugh scoring method.

In patients with end-stage renal disease maintained on hemodialysis, mean AUC was approximately 40% higher compared with historical healthy subject data, consistent with approximately 30% contribution of renal clearance to the total clearance of tofacitinib [see Dosage and Administration (2.3, 2.4, 2.5) and Use in Specific Populations (8.6)].

Drug Interaction Studies

Potential for XELJANZ/XELJANZ XR to Influence the PK of Other Drugs

In vitro studies indicate that tofacitinib does not significantly inhibit or induce the activity of the major human drug-metabolizing CYPs (CYP1A2, CYP2B6, CYP2C8, CYP2C9, CYP2C19, CYP2D6, and CYP3A4) at concentrations corresponding to the steady state Cmax of a 10 mg twice daily dose. These in vitro results were confirmed by a human drug interaction study showing no changes in the pharmacokinetics of midazolam, a highly sensitive CYP3A4 substrate, when concomitantly administered with XELJANZ.

In vitro studies indicate that tofacitinib does not significantly inhibit the activity of the major human drug-metabolizing uridine 5'-diphospho-glucuronosyltransferases (UGTs) [UGT1A1, UGT1A4, UGT1A6, UGT1A9, and UGT2B7] at concentrations exceeding 250 times the steady state Cmax of a 10 mg twice daily dose.

In patients with RA, the oral clearance of tofacitinib does not vary with time, indicating that tofacitinib does not normalize CYP enzyme activity in patients with RA. Therefore, concomitant use with XELJANZ/XELJANZ XR is not expected to result in clinically relevant increases in the metabolism of CYP substrates in patients with RA.

In vitro data indicate that the potential for tofacitinib to inhibit transporters such as P-glycoprotein, organic anionic or cationic transporters at therapeutic concentrations is low.

The impact of tofacitinib on the PK of other drugs for the concomitant drugs are shown in Figure 2.

Figure 2: Impact of Tofacitinib on the Pharmacokinetics of Other Drugs

Note: Reference group is administration of concomitant medication alone; OCT = Organic Cationic Transporter; MATE = Multidrug and Toxic Compound Extrusion.

Potential for Other Drugs to Influence the Pharmacokinetics of Tofacitinib

Since tofacitinib is metabolized by CYP3A4, interaction with drugs that inhibit or induce CYP3A4 is likely. Inhibitors of CYP2C19 alone or P-glycoprotein are unlikely to substantially alter the pharmacokinetics of tofacitinib (see Figure 3).

Figure 3: Impact of Other Drugs on the Pharmacokinetics of Tofacitinib

Note: Reference group is administration of XELJANZ alone.

13 NONCLINICAL TOXICOLOGY

13.1 Carcinogenesis, Mutagenesis, Impairment of Fertility

In a 39-week toxicology study in monkeys, tofacitinib at exposure levels approximately 6 times the recommended dose of 5 mg twice daily, and approximately 3 times the 10 mg twice daily dose (on an AUC basis at oral doses of 5 mg/kg twice daily) produced lymphomas. No lymphomas were observed in this study at exposure levels 1 times the recommended dose of 5 mg twice daily, and approximately 0.5 times the 10 mg twice daily dose (on an AUC basis at oral doses of 1 mg/kg twice daily).

The carcinogenic potential of tofacitinib was assessed in 6-month rasH2 transgenic mouse carcinogenicity and 2-year rat carcinogenicity studies. Tofacitinib, at exposure levels approximately 34 times the recommended dose of 5 mg twice daily, and approximately 17 times the 10 mg twice daily dose (on an AUC basis at oral doses of 200 mg/kg/day) was not carcinogenic in mice.

In the 24-month oral carcinogenicity study in Sprague-Dawley rats, tofacitinib caused benign Leydig cell tumors, hibernomas (malignancy of brown adipose tissue), and benign thymomas at doses greater than or equal to 30 mg/kg/day (approximately 42 times the exposure levels at the recommended dose of 5 mg twice daily, and approximately 21 times the 10 mg twice daily dose on an AUC basis). The relevance of benign Leydig cell tumors to human risk is not known.

Tofacitinib was not mutagenic in the bacterial reverse mutation assay. It was positive for clastogenicity in the in vitro chromosome aberration assay with human lymphocytes in the presence of metabolic enzymes, but negative in the absence of metabolic enzymes. Tofacitinib was negative in the in vivo rat micronucleus assay and in the in vitro CHO-HGPRT assay and the in vivo rat hepatocyte unscheduled DNA synthesis assay.

In rats, tofacitinib at exposure levels approximately 17 times the recommended dose of 5 mg twice daily, and approximately 8.3 times the 10 mg twice daily dose (on an AUC basis at oral doses of 10 mg/kg/day) reduced female fertility due to increased post-implantation loss. There was no impairment of female rat fertility at exposure levels of tofacitinib equal to the recommended dose of 5 mg twice daily, and approximately 0.5 times the 10 mg twice daily dose (on an AUC basis at oral doses of 1 mg/kg/day). Tofacitinib exposure levels at approximately 133 times the recommended dose of 5 mg twice daily, and approximately 67 times the 10 mg twice daily dose (on an AUC basis at oral doses of 100 mg/kg/day) had no effect on male fertility, sperm motility, or sperm concentration.

14 CLINICAL STUDIES

14.1 Clinical Studies in Rheumatoid Arthritis

The rheumatoid arthritis (RA) clinical development program with XELJANZ tablets (referred to as “XELJANZ” in this subsection of labeling) included six randomized controlled trials in adults with moderate to severe active RA.

Trial Design

- Study RA-I (NCT00814307) was a 6-month monotherapy trial in which 610 patients with moderate to severe active RA who had an inadequate response to a DMARD (nonbiologic or biologic) received XELJANZ 5 mg or 10 mg twice daily or placebo added to their background DMARD. At the Month 3 visit, all patients randomized to placebo treatment were switched in a blinded fashion to a second predetermined treatment of XELJANZ 5 mg or 10 mg twice daily. The primary endpoints at Month 3 were the proportion of patients who achieved an ACR20 response, changes in Health Assessment Questionnaire – Disability Index (HAQ-DI), and rates of Disease Activity Score DAS28-4(ESR) less than 2.6.
- Study RA-II (NCT00856544) was a 12-month trial in which 792 patients with moderate to severe active RA who had an inadequate response to a nonbiologic DMARD received XELJANZ 5 mg or 10 mg twice daily or placebo added to background DMARD treatment (excluding potent immunosuppressive treatments such as azathioprine or cyclosporine). At the Month 3 visit, nonresponding patients were switched in a blinded fashion to a second predetermined treatment of XELJANZ 5 mg or 10 mg twice daily. At the end of Month 6, all patients treated with placebo were switched to their second predetermined XELJANZ treatment in a blinded fashion. The primary endpoints were the proportion of patients who achieved an ACR20 response at Month 6, changes in HAQ-DI at Month 3, and rates of DAS28-4(ESR) less than 2.6 at Month 6.
- Study RA-III (NCT00853385) was a 12-month trial in 717 patients with moderate to severe active RA who had an inadequate response to methotrexate (MTX). Patients received XELJANZ 5 mg or 10 mg orally twice daily, adalimumab 40 mg subcutaneously every other week, or placebo added to background MTX. Patients treated with placebo were switched as in Study RA-II. The primary endpoints were the proportion of patients who achieved an ACR20 response at Month 6, HAQ-DI at Month 3, and DAS28-4(ESR) less than 2.6 at Month 6.
- Study RA-IV (NCT00847613) was a 2-year trial with a planned analysis at 1 year in which 797 patients with moderate to severe active RA who had an inadequate response to MTX received XELJANZ 5 mg or 10 mg twice daily or placebo added to background MTX. Patients treated with placebo were switched as in Study RA-II. The primary endpoints were the proportion of patients who achieved an ACR20 response at Month 6, mean change from baseline in van der Heijde-modified total Sharp Score (mTSS) at Month 6, HAQ-DI at Month 3, and DAS28-4(ESR) less than 2.6 at Month 6.
- Study RA-V (NCT00960440) was a 6-month trial in which 399 patients with moderate to severe active RA who had an inadequate response to at least one approved TNF blocking biological product received XELJANZ 5 mg or 10 mg twice daily or placebo added to background MTX. At the Month 3 visit, all patients randomized to placebo treatment were switched in a blinded fashion to a second predetermined treatment of XELJANZ 5 or 10 mg twice daily. The primary endpoints at Month 3 were the proportion of patients who achieved an ACR20 response, HAQ-DI, and DAS28-4(ESR) less than 2.6.
- Study RA-VI (NCT01039688) was a 2-year monotherapy trial with a planned analysis at 1 year in which 952 MTX-naïve patients with moderate to severe active RA received XELJANZ 5 or 10 mg twice daily or MTX dose-titrated over 8 weeks to 20 mg weekly. The primary endpoints were mean change from baseline in van der Heijde-modified Total Sharp Score (mTSS) at Month 6 and the proportion of patients who achieved an ACR70 response at Month 6.

Although other dosages have been studied, the recommended dosage of XELJANZ is 5 mg twice daily. XELJANZ 10 mg twice daily is not recommended for the treatment of RA [see Dosage and Administration (2.3)].

Clinical Response

The percentages of XELJANZ-treated patients who achieved ACR20, ACR50, and ACR70 responses in Studies RA-I, IV, and V are shown in Table 10. Similar results were observed with Studies RA-II and III. In trials RA-I through V, patients treated with 5 mg twice daily XELJANZ had higher ACR20, ACR50, and ACR70 response rates versus patients treated with placebo, with or without background DMARD treatment, at Month 3 and Month 6. Higher ACR20 response rates were observed within 2 weeks compared to placebo. In the 12-month trials, ACR response rates in XELJANZ-treated patients were consistent at 6 and 12 months.

Table 10: Proportion of Adults with Moderate to Severe Active RA with an ACR Response at Months 3 and 6 in Studies RA-I, IV, and V
 | Monotherapy in Nonbiologic or Biologic DMARD Inadequate Responders [Inadequate response to at least one DMARD (biologic or nonbiologic) due to lack of efficacy or toxicity.] |  | MTX Inadequate Responders [Inadequate response to MTX defined as the presence of sufficient residual disease activity to meet the entry criteria.] |  | TNF Blocker Inadequate Responders [Inadequate response to a least one TNF blocker due to lack of efficacy and/or intolerance.]
 | Study RA-I |  | Study RA-IV |  | Study RA-V
N [N is number of randomized and treated patients.] | Placebo + background DMARD | XELJANZ; 5 mg Twice Daily + background DMARD | Placebo + background MTX | XELJANZ; 5 mg Twice Daily + background MTX | Placebo + background MTX | XELJANZ; 5 mg Twice Daily + background MTX
 | 122 | 243 | 160 | 321 | 132 | 133
ACR20; Month 3; Month 6 | 26%; NA [NA (not applicable), as data for placebo treatment is not available beyond 3 months in Studies RA-I and RA-V due to placebo advancement.] | 59%; 69% | 27%; 25% | 55%; 50% | 24%; NA | 41%; 51%
ACR50; Month 3; Month 6 | 12%; NA | 31%; 42% | 8%; 9% | 29%; 32% | 8%; NA | 26%; 37%
ACR70; Month 3; Month 6 | 6%; NA | 15%; 22% | 3%; 1% | 11%; 14% | 2%; NA | 14%; 16%

In Study RA-IV, a greater proportion of patients treated with XELJANZ 5 mg twice daily plus MTX achieved a low level of disease activity as measured by a DAS28-4(ESR) less than 2.6 at 6 months compared to those treated with MTX alone (Table 11).

Table 11: Proportion and Numbers of Adults with Moderate to Severe Active RA with DAS28-4(ESR) Less Than 2.6 with Number of Residual Active Joints at Month 6 in Study RA-IV
 | Study RA-IV
DAS28-4(ESR) Less Than 2.6 | Placebo + MTX; 160 | XELJANZ 5 mg Twice Daily + MTX; 321
Proportion of responders at Month 6 (n) | 1% (2) | 6% (19)
Of responders, proportion with 0 active joints (n) | 50% (1) | 42% (8)
Of responders, proportion with 1 active joint (n) | 0 | 5% (1)
Of responders, proportion with 2 active joints (n) | 0 | 32% (6)
Of responders, proportion with 3 or more active joints (n) | 50% (1) | 21% (4)

The results of the components of the ACR response criteria for Study RA-IV are shown in Table 12. Similar results were observed for XELJANZ in Studies RA-I, II, III, V, and VI.

Table 12: Components of ACR Response in Adults with Moderate to Severe Active RA at Baseline and Month 3 in Study RA-IV
 | Study RA-IV
 | Placebo + MTX; N=160 |  | XELJANZ; 5 mg; Twice Daily + MTX; N=321
Component (mean) [Data shown is mean (Standard Deviation) at Month 3.] | Baseline | Month 3 | Baseline | Month 3
Number of tender joints; (0-68) | 23; (13) | 18; (14) | 24; (14) | 13; (14)
Number of swollen joints; (0-66) | 14; (9) | 10; (9) | 14; (8) | 6; (8)
Pain [Visual analog scale: 0 = best, 100 = worst.] | 55; (24) | 47; (24) | 58; (23) | 34; (23)
Patient global assessment | 54; (23) | 47; (24) | 58; (24) | 35; (23)
Disability index; (HAQ-DI) [Health Assessment Questionnaire Disability Index: 0 = best, 3 = worst; 20 questions; categories: dressing and grooming, arising, eating, walking, hygiene, reach, grip, and activities.] | 1.32; (0.67) | 1.19; (0.68) | 1.41; (0.68) | 0.99; (0.65)
Physician global assessment | 56; (18) | 43; (22) | 59; (16) | 30; (19)
CRP (mg/L) | 13.7; (14.9) | 14.6; (18.7) | 15.3; (19.0) | 7.1; (19.1)

The percent of ACR20 responders by visit for Study RA-IV is shown in Figure 4. Similar responses were observed for XELJANZ in Studies RA-I, II, III, V, and VI.

Figure 4: Percentage of ACR20 Responders by Visit Through Month 6 in Study RA-IV

Radiographic Response

Two studies were conducted to evaluate the effect of XELJANZ on structural joint damage. In Study RA-IV and Study RA-VI, progression of structural joint damage was assessed radiographically and expressed as change from baseline in mTSS and its components, the erosion score and joint space narrowing score, at Months 6 and 12. The proportion of patients with no radiographic progression (mTSS change less than or equal to 0) was also assessed.

In Study RA-IV, XELJANZ 5 mg twice daily reduced the mean progression of structural damage (not statistically significant) as shown in Table 13. Analyses of erosion and joint space narrowing scores were consistent with the overall results.

In the placebo plus MTX group, 74% of patients experienced no radiographic progression at Month 6 compared to 84% of patients treated with XELJANZ plus MTX 5 mg twice daily.

In Study RA-VI, XELJANZ monotherapy inhibited the progression of structural damage compared to MTX at Months 6 and 12 as shown in Table 13. Analyses of erosion and joint space narrowing scores were consistent with the overall results.

In the MTX group, 55% of patients experienced no radiographic progression at Month 6 compared to 73% of patients treated with XELJANZ 5 mg twice daily.

Table 13: Radiographic Changes in Adults with Moderate to Severe Active RA at Months 6 and 12 in Studies RA-IV and VI
 | Study RA-IV
 | Placebo N=139 Mean (SD) [SD = Standard Deviation] | XELJANZ 5 mg Twice Daily N=277 Mean (SD) | XELJANZ 5 mg Twice Daily Mean Difference from Placebo [Difference between least squares means XELJANZ minus placebo or MTX (95% CI = 95% confidence interval)] (CI)
mTSS [Month 6 and Month 12 data are mean change from baseline.]
Baseline | 33 (42) | 31 (48) | -
Month 6 | 0.5 (2.0) | 0.1 (1.7) | -0.3 (-0.7, 0.0)
 | Study RA-VI
 | MTX N=166 Mean (SD) | XELJANZ 5 mg Twice Daily N=346 Mean (SD) | XELJANZ 5 mg Twice Daily Mean Difference from MTX (CI)
mTSS
Baseline | 17 (29) | 20 (40) | -
Month 6 | 0.8 (2.7) | 0.2 (2.3) | -0.7 (-1.0, -0.3)
Month 12 | 1.3 (3.7) | 0.4 (3.0) | -0.9 (-1.4, -0.4)

Physical Function Response

Improvement in physical functioning was measured by the HAQ-DI. Patients who received XELJANZ 5 mg twice daily demonstrated greater improvement from baseline in physical functioning compared to patients who received placebo at Month 3.

The mean (95% CI) difference from placebo in HAQ-DI improvement from baseline at Month 3 in Study RA-III was -0.22 (-0.35, -0.10) in patients who received 5 mg XELJANZ twice daily. Similar results were obtained in Studies RA-I, II, IV and V. In the 12-month trials, HAQ-DI results in XELJANZ-treated patients were consistent at 6 and 12 months.

Other Health-Related Outcomes

General health status was assessed by the Short Form health survey (SF-36). In Studies RA-I, IV, and V, patients who received XELJANZ 5 mg twice daily demonstrated greater improvement from baseline compared to placebo in physical component summary (PCS), mental component summary (MCS) scores and in all 8 domains of the SF-36 at Month 3.

14.2 Clinical Studies in Psoriatic Arthritis

The psoriatic arthritis (PsA) clinical development program with XELJANZ tablets (referred to as “XELJANZ” in this subsection of labeling) included 2 multicenter, randomized, double-blind, placebo-controlled trials in 816 adults with active PsA (Studies PsA-I and PsA-II).

Trial Designs and Population

All patients had active PsA for at least 6 months based upon the Classification Criteria for Psoriatic Arthritis (CASPAR), at least 3 tender/painful joints and at least 3 swollen joints, and active plaque psoriasis. Patients randomized and treated across the 2 clinical trials represented different PsA subtypes at screening, including <5 joints or asymmetric involvement (21%), ≥5 joints involved (90%), distal interphalangeal (DIP) joint involvement (61%), arthritis mutilans (8%), and spondylitis (19%). Patients in these clinical trials had a diagnosis of PsA for a mean (SD) of 7.7 (7.2) years. At baseline, 80% and 53% of patients had enthesitis and dactylitis, respectively. At baseline, all patients were required to receive treatment with a stable dose of a nonbiologic DMARD (79% received methotrexate, 13% received sulfasalazine, 7% received leflunomide, 1% received other nonbiologic DMARDs). In both clinical trials, the primary endpoints were the ACR20 response and the change from baseline in HAQ-DI at Month 3.

- Study PsA-I was a 12-month clinical trial in 422 patients who had an inadequate response to a nonbiologic DMARD (67% and 33% were inadequate responders to 1 nonbiologic DMARD and ≥2 nonbiologic DMARDs, respectively) and who were naïve to treatment with a TNF blocker. Although Study PsA-1 included patients who are TNF blocker-naïve, XELJANZ and XELJANZ XR are not approved for use in TNF blocker-naïve patients [see Indications and Usage (1.2)]. Patients were randomized in a 2:2:2:1:1 ratio to receive XELJANZ 5 mg twice daily, XELJANZ 10 mg twice daily, adalimumab 40 mg subcutaneously once every 2 weeks, placebo to XELJANZ 5 mg twice daily treatment sequence, or placebo to XELJANZ 10 mg twice daily treatment sequence, respectively; study drug was added to background nonbiologic DMARD treatment. At the Month 3 visit, all patients randomized to placebo treatment were switched in a blinded fashion to a predetermined XELJANZ dosage of 5 mg or 10 mg twice daily. Study PsA-I was not designed to demonstrate noninferiority or superiority to adalimumab.
- Study PsA-II was a 6-month clinical trial in 394 patients who had an inadequate response to at least 1 approved TNF blocker (66%, 19%, and 15% were inadequate responders to 1 TNF blocker, 2 TNF blockers and ≥3 TNF blockers, respectively). Patients were randomized in a 2:2:1:1 ratio to receive XELJANZ 5 mg twice daily, XELJANZ 10 mg twice daily, placebo to XELJANZ 5 mg twice daily treatment sequence, or placebo to XELJANZ 10 mg twice daily treatment sequence, respectively; study drug was added to background nonbiologic DMARD treatment. At the Month 3 visit, placebo patients were switched in a blinded fashion to a predetermined XELJANZ dosage of 5 mg or 10 mg twice daily as in Study PsA-I.

Although other dosages have been studied, the recommended dosage of XELJANZ is 5 mg twice daily. XELJANZ 10 mg twice daily is not recommended for treatment of PsA [see Dosage and Administration (2.3)].

Clinical Response

At Month 3, patients treated with XELJANZ 5 mg twice daily had higher (p≤0.05) response rates versus placebo for ACR20, ACR50, and ACR70 in Study PsA-I and for ACR20 and ACR50 in Study PsA-II; ACR70 response rates were also higher for XELJANZ 5 mg twice daily versus placebo in Study PsA-II, although the differences versus placebo were not statistically significant (p>0.05) (Tables 14 and 15).

Table 14: Proportion of Adults with Active PsA with an ACR Response at Month 3 in Study PsA-I [Patients received one concomitant nonbiologic DMARD.] [Nonbiologic DMARD Inadequate Responders (TNF Blocker-Naïve)] [XELJANZ and XELJANZ XR are not approved for use in TNF blocker-naïve patients [see Indications and Usage (1.2)].]
Treatment Group | Placebo | XELJANZ 5 mg Twice Daily + Background Nonbiologic DMARD
N [N is number of randomized and treated patients.] | 105 | 107
 | Response Rate | Response Rate | Difference (%) 95% CI from Placebo
Month 3
ACR20 | 33% | 50% | 17.1 (4.1, 30.2)
ACR50 | 10% | 28% | 18.5 (8.3, 28.7)
ACR70 | 5% | 17% | 12.1 (3.9, 20.2)
Patients with missing data were treated as non-responders.

Table 15: Proportion of Adults with Active PsA with an ACR Response at Month 3 in Study PsA-II [Patients received one concomitant nonbiologic DMARD.] (TNF Blocker Inadequate Responders)
Treatment Group | Placebo | XELJANZ 5 mg Twice Daily
N [N is number of randomized and treated patients.] | 131 | 131
 | Response Rate | Response Rate | Difference (%) 95% CI from Placebo
Month 3
ACR20 | 24% | 50% | 26.0 (14.7, 37.2)
ACR50 | 15% | 30% | 15.3 (5.4, 25.2)
ACR70 | 10% | 17% | 6.9 (-1.3, 15.1)
Patients with missing data were treated as non-responders.

Improvements from baseline in the ACR response criteria components for both studies are shown in Table 16.

Table 16: Components of ACR Response in Adults with Active PsA at Baseline and Month 3 in Studies PsA-I and PsA-II
 | Nonbiologic DMARD Inadequate Responders (TNF Blocker-Naïve) |  | TNF Blocker Inadequate Responders
 | Study PsA-I [Patients received one concomitant nonbiologic DMARD.] , [XELJANZ and XELJANZ XR are not approved for use in TNF blocker-naïve patients [see Indications and Usage (1.2)].] |  | Study PsA-II
Treatment Group | Placebo | XELJANZ 5 mg Twice Daily | Placebo | XELJANZ 5 mg Twice Daily
N at Baseline | 105 | 107 | 131 | 131
ACR Component [Data shown are mean value at baseline and at Month 3.]
Number of tender/painful joints (0–68)
Baseline | 20.6 | 20.5 | 19.8 | 20.5
Month 3 | 14.6 | 12.2 | 15.1 | 11.5
Number of swollen joints (0–66)
Baseline | 11.5 | 12.9 | 10.5 | 12.1
Month 3 | 7.1 | 6.3 | 7.7 | 4.8
Patient assessment of arthritis pain [Visual analog scale (VAS): 0 = best, 100 = worst.]
Baseline | 53.2 | 55.7 | 54.9 | 56.4
Month 3 | 44.7 | 34.7 | 48.0 | 36.1
Patient global assessment of arthritis
Baseline | 53.9 | 54.7 | 55.8 | 57.4
Month 3 | 44.4 | 35.5 | 49.2 | 36.9
HAQ-DI [HAQ-DI = Health Assessment Questionnaire – Disability Index: 0 = best, 3 = worst; 20 questions; categories: dressing and grooming, arising, eating, walking, hygiene, reach, grip, and activities.]
Baseline | 1.11 | 1.16 | 1.25 | 1.26
Month 3 | 0.95 | 0.81 | 1.09 | 0.88
Physician's Global Assessment of Arthritis
Baseline | 53.8 | 54.6 | 53.7 | 53.5
Month 3 | 35.4 | 29.5 | 36.4 | 27.0
CRP (mg/L)
Baseline | 10.4 | 10.5 | 12.1 | 13.8
Month 3 | 8.6 | 4.0 | 11.4 | 7.7

The percentage of ACR20 responders by visit for Study PsA-I is shown in Figure 5. Similar responses were observed in Study PsA-II. In both studies, improvement in ACR20 response on XELJANZ was observed at the first visit after baseline (Week 2).

Figure 5: Percentage of ACR20 Responders by Visit Through Month 3 in Study PsA-I [Subjects received one concomitant nonbiologic DMARD.] [XELJANZ and XELJANZ XR are not approved for use in TNF blocker-naïve patients [see Indications and Usage (1.2)].]

BID = twice daily; SE = standard error.

Patients with missing data were treated as non-responders.

In patients with active PsA evidence of benefit in enthesitis and dactylitis was observed with XELJANZ treatment.

Physical Function

Improvement in physical functioning was measured by the HAQ-DI. Patients receiving XELJANZ 5 mg twice daily demonstrated significantly greater improvement (p ≤0.05) from baseline in physical functioning compared to placebo at Month 3 (Table 17).

Table 17: Change from Baseline in HAQ-DI in Adults with Active PsA at Month 3 Studies PsA-I and PsA-II
 | Least Squares Mean Change from Baseline In HAQ-DI at Month 3
 | Nonbiologic DMARD Inadequate Responders [Inadequate response to at least one nonbiologic DMARD due to lack of efficacy and/or intolerability.] (TNF Blocker-Naïve) |  | TNF Blocker Inadequate Responders [Inadequate response to at least one TNF blocker due to lack of efficacy and/or intolerability.]
 | Study PsA-I [Patients received one concomitant nonbiologic DMARD.] , [XELJANZ and XELJANZ XR are not approved for use in TNF blocker-naïve patients [see Indications and Usage (1.2)].] |  | Study PsA-II
Treatment Group | Placebo | XELJANZ 5 mg Twice Daily | Placebo | XELJANZ 5 mg Twice Daily
N [N is the total number of patients in the statistical analysis.] | 104 | 107 | 131 | 129
LSM Change from Baseline | -0.18 | -0.35 | -0.14 | -0.39
Difference from Placebo (95% CI) | - | -0.17 (-0.29, -0.05) | - | -0.25 (-0.38, -0.13)

In Study PsA-I, the HAQ-DI responder rate (response defined as having improvement from baseline of ≥0.35) at Month 3 was 53% in patients receiving XELJANZ 5 mg twice daily and 31% in patients receiving placebo. Similar responses were observed in Study PsA-II.

Other Health-Related Outcomes

General health status was assessed by the Short Form health survey (SF-36). In Studies PsA-I and PsA-II, patients receiving XELJANZ 5 mg twice daily had greater improvement from baseline compared to placebo in Physical Component Summary (PCS) score, but not in Mental Component Summary (MCS) score at Month 3. Patients receiving XELJANZ 5 mg twice daily reported consistently greater improvement relative to placebo in the domains of Physical Functioning, Bodily Pain, Vitality, and Social Functioning, but not in Role-Physical, General Health, Role-Emotional, or Mental Health.

Radiographic Response

Treatment effect on inhibition of radiographic progression in PsA could not be established from the results of Study PsA-I.

14.3 Clinical Studies in Ankylosing Spondylitis

The ankylosing spondylitis (AS) clinical development program with XELJANZ tablets (referred to as “XELJANZ” in this subsection of labeling) included one placebo-controlled trial (Study AS-I) in adults with active AS. Patients had active disease as defined by both Bath Ankylosing Spondylitis Disease Activity Index (BASDAI) and back pain score (BASDAI question 2) of greater or equal to 4 despite non-steroidal anti-inflammatory drug (NSAID), corticosteroid or disease modifying anti-rheumatic drug (DMARD) therapy.

Trial Design

Study AS-I was a randomized, double-blind, placebo-controlled, 48-week clinical trial in 269 adult patients who had an inadequate response (inadequate clinical response or intolerance) to at least 2 NSAIDs. Although Study AS-I included some patients who are TNF blocker-naïve, XELJANZ and XELJANZ XR are not approved for use in TNF blocker-naïve patients [see Indications and Usage (1.3)]. Patients were randomized and treated with XELJANZ 5 mg twice daily or placebo for 16 weeks of blinded treatment and then all received treatment of XELJANZ 5 mg twice daily for additional 32 weeks. The primary endpoint was to evaluate the proportion of patients who achieved an ASAS20 response at Week 16.

Approximately 7% and 21% of patients used concomitant methotrexate or sulfasalazine, respectively from baseline to Week 16. Twenty-two percent of patients had an inadequate response to 1 or 2 TNF blockers.

Clinical Response

Patients treated with XELJANZ 5 mg twice daily achieved greater improvements in ASAS20 and ASAS40 responses compared to patients treated with placebo at Week 16 (Table 18). Consistent results were observed in the subgroup of patients who had an inadequate response to TNF blockers for both the ASAS20 (primary endpoint) and ASAS40 (secondary endpoint) at Week 16 (Table 18).

Table 18: ASAS20 and ASAS40 Responses in Adults with Active AS at Week 16 in Study AS-I
 | Placebo | XELJANZ 5 mg Twice Daily | Difference from Placebo (95% CI)
All patients (N) | N=136 | N=133
ASAS20 response [type I error-controlled.] , % | 29 | 56 | 27 (16, 38) [p-value <0.0001.]
ASAS40 response, % | 13 | 41 | 28 (18, 38)
TNFi-IR patients (N) | N=30 | N=29
ASAS20 response, % | 17 | 41 | 25 (2, 47)
ASAS40 response, % | 7 | 28 | 21 (2, 39)
Abbreviations: CI = confidence interval; TNFi-IR = tumor necrosis factor inhibitor inadequate response.

The improvements in the components of the ASAS response and other measures of disease activity were greater in the XELJANZ 5 mg twice daily group compared to the placebo group as shown in Table 19.

Table 19: ASAS Components and Other Measures of Disease Activity in Adults with Active AS at Week 16 in Study AS-I
 | Placebo (N=136) |  | XELJANZ 5 mg Twice Daily (N=133)
 | Baseline (mean) | Week 16 (LSM change from Baseline) [Estimates are generated based on a mixed model for repeated measures using both on-treatment and off-treatment data.] | Baseline (mean) | Week 16 (LSM change from Baseline) | Difference from Placebo (95% CI)
ASAS Components
- Patient Global Assessment of Disease Activity (0–10) [Measured on a numerical rating scale with 0 = not active or no pain, 10 = very active or most severe pain.] , [type I error-controlled.] | 7.0 | -1.0 | 6.9 | -2.5 | -1.5 (-2.00, -0.97) [p < 0.0001.]
- Total spinal pain (0–10), | 6.9 | -1.1 | 6.9 | -2.6 | -1.5 (-2.00, -1.03)
- BASFI (0–10) [Bath Ankylosing Spondylitis Functional Index measured on a numerical rating scale with 0 = easy and 10 = impossible.] , | 5.9 | -0.8 | 5.8 | -2.0 | -1.2 (-1.64, -0.79)
- Inflammation (0–10) [Inflammation is the mean of two patient-reported stiffness self-assessments in BASDAI.] , | 6.8 | -1.1 | 6.6 | -2.8 | -1.7 (-2.13, -1.18)
BASDAI Score [BASDAI total score.] | 6.5 | -1.2 | 6.4 | -2.6 | -1.4 (-1.86, -0.98)
BASMI [Bath Ankylosing Spondylitis Metrology Index.] , | 4.4 | -0.1 | 4.5 | -0.6 | -0.5 (-0.66, -0.36)
hsCRP [High sensitivity C-reactive protein.] , (mg/dL) | 1.8 | -0.1 | 1.6 | -1.1 | -0.9 (-1.17, -0.69)
LSM = least squares mean.

The percentage of patients with active AS who achieved ASAS20 response by visit is shown in Figure 6.

Figure 6: Percentage of ASAS20 Responders Over Time Up to Week 16 in Patients with Active AS in Study AS-I

SE = standard error.
Patients with missing data were treated as non-responders.

Other Health-Related Outcomes

Patients treated with XELJANZ 5 mg twice daily achieved greater improvements from baseline in Ankylosing Spondylitis Quality of Life (ASQoL) (-4.0 vs -2.0) compared to patients treated with placebo at Week 16.

14.4 Clinical Studies in Polyarticular Course Juvenile Idiopathic Arthritis

The efficacy of XELJANZ (tablets and oral solution) for pcJIA was assessed in Study pcJIA-I (NCT02592434). This was a 44-week, two-part study (that consisted of an 18-week, open-label, run-in phase, followed by a 26-week double-blind, placebo-controlled, randomized withdrawal phase) in pediatric patients 2 years to 17 years of age with active rheumatoid factor (RF) negative polyarthritis, RF positive polyarthritis, extended oligoarthritis, and systemic JIA without systemic manifestations who had an inadequate response or intolerance to at least one DMARD which could have included MTX or biologic agents. This study also included patients ages 2 years to 17 years of age with active juvenile psoriatic arthritis (jPsA) and enthesitis-related arthritis (ERA) who had an inadequate response to NSAIDs. Although the clinical studies included some patients who are TNF blocker-naïve, XELJANZ is not approved for use in TNF blocker-naïve patients [see Indications and Usage (1.4)].

Patients received XELJANZ (dosed at 5 mg twice daily or body weight-based equivalent twice daily) for 18 weeks (run-in phase) followed by randomization to either XELJANZ (dosed at 5 mg twice daily or body weight-based equivalent twice daily) or placebo for 26 weeks (double-blind phase). Only patients who achieved at least a JIA ACR30 response at the end of the run-in phase were randomized (1:1) to the double-blind phase. Treatment with a stable dose of MTX was permitted but was not required during the study. Concurrent use of biologics or DMARDs other than MTX was not permitted in the study.

Baseline Disease Characteristics

A total of 225 pediatric patients with JIA (56 male and 169 female) with active polyarthritis were enrolled in the run-in phase including RF negative (104), RF positive (39), extended oligoarthritis (28), systemic JIA without systemic manifestations (13), jPsA (20), and ERA (21). Patients had a mean (SD) disease duration of 3.8 ± 3.5 years, and a mean (SD) number of active joints of 12.2 ± 8.1.

Efficacy Results

Of the 225 patients, 173 (77%) patients achieved JIA ACR30 response at Week 18 and were randomized into the double-blind phase to either XELJANZ (n=88) or placebo (n=85). At the conclusion of the 18-week, open-label, run-in phase, pediatric ACR 30/50/70 responses were 77%, 70%, and 49%, respectively.

In both the run-in and double-blind phases, approximately one-third of the patients were taking concomitant oral corticosteroids, and approximately two-thirds were taking concomitant MTX.

The primary endpoint was the occurrence of disease flare at Week 44 relative to the double-blind phase baseline at Week 18. Disease flare was defined (according to Pediatric Rheumatology Collaborative Study Group (PRCSG)/Pediatric Rheumatology International Trials Organization (PRINTO) Disease Flare criteria) as worsening of ≥30% in 3 or more of the 6 JIA core response variables with no more than 1 of the remaining JIA core response variables improving by ≥30%.

XELJANZ-treated patients experienced significantly fewer disease flares at Week 44 compared to placebo-treated patients (31% [27/88] vs. 55% [47/85]; difference in proportions -25% [95% CI: -39%, -10%]; p=0.0007). The occurrence of disease flare by visit in Study pcJIA-I is shown in Figure 7.

Figure 7: Occurrence of Disease Flare in Pediatric Patients 2 Years of Age and Older with JIA by Visit from Week 18 to Week 44 in the Double-Blind Phase in Study pcJIA-I

BID = twice daily; SE = standard error; N = total number of patients.

The 26-week double-blind phase is from Week 18 through Week 44 on and after randomization day.

14.5 Clinical Studies in Ulcerative Colitis

The efficacy of XELJANZ tablets (referred to as “XELJANZ” in this subsection of labeling) was evaluated in two 12-week induction studies (UC-I and UC-II), a 52-week maintenance study (UC-III), and a long-term extension study (UC-IV).

Induction Trials (Study UC-I [NCT01465763] and Study UC-II [NCT01458951])

In two identical induction trials (UC-I and UC-II), 1139 adult patients were randomized (598 and 541 patients, respectively) to XELJANZ 10 mg twice daily or placebo with a 4:1 treatment allocation ratio. These trials included adult patients with moderately to severely active UC (total Mayo score of 6 to 12, with an endoscopy subscore of at least 2, and rectal bleeding subscore of at least 1) and who had failed or were intolerant to at least 1 of the following treatments: oral or intravenous corticosteroids, azathioprine, 6-MP or TNF blocker. XELJANZ and XELJANZ XR are indicated only for use in patients who have had inadequate response or intolerance to one or more TNF blockers [see Indications and Usage (1.5)].

The disease activity was assessed by Mayo scoring index (0 to 12) which consists of four subscores (0 to 3 for each subscore): stool frequency, rectal bleeding, findings on endoscopy, and physician global assessment. An endoscopy subscore of 2 was defined by marked erythema, absent vascular pattern, any friability, and erosions; an endoscopy subscore of 3 was defined by spontaneous bleeding and ulceration.

Patients were permitted to use stable doses of oral aminosalicylates and corticosteroids (prednisone daily dose up to 25 mg equivalent). Concomitant immunosuppressants (oral immunomodulators or biologic therapies) were not permitted for UC patients during these studies.

A total of 52%, 73% and 72% of patients had previously failed or were intolerant to TNF blockers (51% in Study UC-1 and 52% in Study UC-II), corticosteroids (75% in Study UC-I and 71% in Study UC-II), and/or immunosuppressants (74% in Study UC-I and 70% in Study UC-II), respectively.

Oral corticosteroids were received as concomitant treatment for UC by 47% of patients (45% in Study UC-I and 48% in Study UC-II) and 71% received concomitant aminosalicylates as treatment for UC (71% in Study UC-I, and 72% in Study UC-II). The baseline clinical characteristics were generally similar between the XELJANZ-treated patients and placebo-treated patients.

The primary endpoint of Study UC-I and Study UC-II was the proportion of patients in remission at Week 8, and the key secondary endpoint was the proportion of patients with improvement of endoscopic appearance of the mucosa at Week 8.

The efficacy results of Study UC-I and Study UC-II based on the centrally read endoscopy results are shown in Table 20.

Table 20: Proportion of Adult Patients with Moderately to Severely Active UC Who Met Primary and Key Secondary Efficacy Endpoints at Week 8 in Study UC-I and Study UC-II (Central Endoscopy Read)
Study UC‑I
Endpoint | Placebo | XELJANZ; 10 mg; Twice Daily | Treatment Difference versus Placebo; (95% CI)
Remission at Week 8 [Remission was defined as clinical remission (a Mayo score ≤2 with no individual subscore >1) and rectal bleeding subscore of 0.]
Total Population | N=122; 8% | N=476; 18% | 10% [p-value <0.01.]; (4.3, 16.3)
With Prior TNF Blocker Failure [Prior TNF blocker failure was defined in this program as inadequate response, loss of response, or intolerance to TNF blocker therapy.] | N=64; 2% | N=243; 11%
Without Prior TNF Blocker Failure [Patients in this group had failed one or more conventional therapies (corticosteroid, azathioprine, 6 mercaptopurine) but did not have history of prior failure of TNF blocker therapy.] , [XELJANZ and XELJANZ XR are indicated only for use in patients who have had inadequate response or intolerance to one or more TNF blockers [see Indications and Usage (1.5)].] | N=58; 16% | N=233; 26%
Improvement of Endoscopic Appearance of the Mucosa at Week 8 [Improvement of endoscopic appearance of the mucosa was defined as Mayo endoscopy subscore of 0 (normal or inactive disease) or 1 (erythema, decreased vascular pattern).]
Total Population | N=122; 16% | N=476; 31% | 16% [p-value <0.001.]; (8.1, 23.4)
With Prior TNF Blocker Failure | N=64; 6% | N=243; 23%
Without Prior TNF Blocker Failure, | N=58; 26% | N=233; 40%
Study UC-II
Endpoint | Placebo | XELJANZ; 10 mg; Twice Daily | Treatment Difference; (95% CI)
Remission at Week 8
Total Population | N=112; 4% | N=429; 17% | 13%; (8.1, 17.9)
With Prior TNF Blocker Failure | N=60; 0% | N=222; 12%
Without Prior TNF Blocker Failure, | N=52; 8% | N=207; 22%
Improvement of Endoscopic Appearance of the Mucosa at Week 8
Total Population | N=112; 12% | N=429; 28% | 17%; (9.5, 24.1)
With Prior TNF Blocker Failure | N=60; 7% | N=222; 22%
Without Prior TNF Blocker Failure, | N=52; 17% | N=207; 36%
CI = Confidence interval; N = number of patients in the analysis set; TNF = tumor necrosis factor

Clinical Response at Week 8

Clinical response was defined as a decrease from baseline in Mayo score of ≥3 points and ≥30%, with an accompanying decrease in the subscore for rectal bleeding of ≥1 point or absolute subscore for rectal bleeding of 0 or 1.

Clinical response was observed in 60% of patients treated with XELJANZ 10 mg twice daily compared to 33% of patients treated with placebo in Study UC-I and 55% compared to 29% in Study UC-II.

Normalization of the Endoscopic Appearance of the Mucosa at Week 8

Normalization of endoscopic appearance of the mucosa was defined as a Mayo endoscopic subscore of 0 and was observed in 7% of patients treated with XELJANZ 10 mg twice daily compared to 2% of treated with placebo in both Studies UC-I and UC-II.

Rectal Bleeding and Stool Frequency

Decreases in rectal bleeding and stool frequency subscores were observed as early as Week 2 in patients treated with XELJANZ.

Maintenance Trial (Study UC-III [NCT01458574])

A total of 593 adult patients who completed the induction trials (UC-I or UC-II) and achieved clinical response were re-randomized with 1:1:1 treatment allocation ratio to XELJANZ 5 mg twice daily, XELJANZ 10 mg twice daily, or placebo for 52 weeks in Study UC-III. XELJANZ 5 mg twice daily is the recommended dosage for maintenance therapy; limit use of XELJANZ 10 mg twice daily beyond induction to those with loss of response and should be used for the shortest duration [see Dosage and Administration (2.5)]. As in the induction trials, patients were permitted to use stable doses of oral aminosalicylates; however, corticosteroid tapering was required upon entrance into this study for patients who were receiving corticosteroids at baseline. Concomitant immunosuppressants (oral immunomodulators or biologic therapies) were not permitted.

At baseline of Study UC-III:

- 179 (30%) patients were in remission
- 289 (49%) patients were receiving oral corticosteroids
- 265 (45%), 445 (75%), and 413 (70%) patients had previously failed or were intolerant to TNF blocker therapy, corticosteroids, and immunosuppressants, respectively. XELJANZ and XELJANZ XR are indicated only for use in patients who have had inadequate response or intolerance to one or more TNF blockers [see Indications and Usage (1.5)].

In Study UC-III, the primary endpoint was the proportion of patients in remission at Week 52. There were two key secondary endpoints: the proportion of patients with improvement of endoscopic appearance at Week 52, and the proportion of patients with sustained corticosteroid-free remission at both Week 24 and Week 52 among patients in remission at baseline of Study UC-III.

The efficacy results of Study UC-III based on the centrally read endoscopy results are summarized in Table 21.

Table 21: Proportion of Adult Patients with Moderately to Severely Active UC Who Met Primary and Key Secondary Efficacy Endpoints in Study UC-III (Central Endoscopy Read)
 |  |  |  | Treatment Difference versus Placebo (95% CI)
Endpoint | Placebo | XELJANZ 5 mg Twice Daily | XELJANZ 10 mg Twice Daily | XELJANZ 5 mg Twice Daily | XELJANZ 10 mg Twice Daily
Remission at Week 52 [Remission was defined as clinical remission (a Mayo score ≤2 with no individual subscore >1) and rectal bleeding subscore of 0.]
Total Population | N=198 | N=198 | N=197 | 23% [p-value <0.0001.] (15.3, 31.2) | 30% (21.4, 37.6)
 | 11% | 34% | 41%
With Prior TNF Blocker Failure [Prior TNF blocker failure was defined in this program as inadequate response, loss of response, or intolerance to TNF blocker therapy.] | N=89 | N=83 | N=93
 | 11% | 24% | 37%
Without Prior TNF Blocker Failure [Patients in this group had failed one or more conventional therapies (corticosteroid, azathioprine, 6-mercaptopurine) but did not have history of prior failure of TNF blocker therapy.] [XELJANZ and XELJANZ XR are indicated only for use in patients who have had inadequate response or intolerance to one or more TNF blockers [see Indications and Usage (1.5)].] | N=109 | N=115 | N=104
 | 11% | 42% | 44%
Improvement of endoscopic appearance of the mucosa at Week 52 [Improvement of endoscopic appearance of the mucosa was defined as Mayo endoscopy subscore of 0 (normal or inactive disease) or 1 (erythema, decreased vascular pattern).]
Total Population | N=198 | N=198 | N=197 | 24% (16.0, 32.5) | 33% (24.2, 41.0)
 | 13% | 37% | 46%
With Prior TNF Blocker Failure | N=89 | N=83 | N=93
 | 12% | 30% | 40%
Without Prior TNF Blocker Failure | N=109 | N=115 | N=104
 | 14% | 43% | 51%
Sustained corticosteroid-free remission at both Week 24 and Week 52 among patients in remission at baseline [Sustained corticosteroid-free remission was defined as being in remission and not taking corticosteroids for at least 4 weeks prior to the visit at both Week 24 and Week 52.]
Total Population | N=59 | N=65 | N=55 | 30% (17.4, 43.2) | 42% (27.9, 56.5)
 | 5% | 35% | 47%
With Prior TNF Blocker Failure | N=21 | N=18 | N=18
 | 5% | 22% | 39%
Without Prior TNF Blocker Failure | N=38 | N=47 | N=37
 | 5% | 40% | 51%
CI = Confidence interval; N = number of patients in the analysis set; TNF = tumor necrosis factor.

Maintenance of Clinical Response

Maintenance of clinical response was defined as the proportion of patients who met the definition of clinical response (defined as a decrease from the induction study (UC-I, UC-II) baseline Mayo score of ≥3 points and ≥30%, with an accompanying decrease in the rectal bleeding subscore of ≥1 point or rectal bleeding subscore of 0 or 1) at both Baseline and Week 52 of Study UC-III.

Maintenance of clinical response was observed in 20% in the placebo group, 52% in the XELJANZ 5 mg twice daily group, and 62% in the XELJANZ 10 mg twice daily group.

Maintenance of Remission (Among Patients in Remission at Baseline)

In the 179 patients who were in remission at baseline of Study UC-III (N = 59 for placebo, N = 65 for XELJANZ 5 mg twice daily, N = 55 for XELJANZ 10 mg twice daily), 10% in the placebo group, 46% in the XELJANZ 5 mg twice daily group and 56% in the XELJANZ 10 mg twice daily group maintained remission at Week 52.

Normalization of the Endoscopic Appearance of the Mucosa

Normalization of endoscopic appearance of the mucosa was defined as a Mayo endoscopic subscore of 0 and was observed at Week 52 in 15% of patients in the XELJANZ 5 mg twice daily group and 17% of patients in the XELJANZ 10 mg twice daily group compared to 4% of placebo patients.

Open-label Extension Study (Study UC-IV [NCT01470612])

In Study UC-IV, 914 patients were treated of which 156 received XELJANZ 5 mg twice daily and 758 received XELJANZ 10 mg twice daily.

Of the 905 patients who were assigned to XELJANZ 10 mg twice daily in the 8-week induction studies (Study UC-I or Study UC-II), 322 patients completed the induction studies but did not achieve clinical response. Of these 322 patients, 291 continued to receive XELJANZ 10 mg twice daily (unblinded) and had available data after an additional 8 weeks in Study UC-IV. After 8 additional weeks (a total of 16 weeks treatment), 148 patients achieved clinical response, and 25 patients achieved remission (based on central endoscopy read). Among those 143 patients who achieved clinical response by 16 weeks and had available data at Week 52, 66 patients achieved remission (based on local endoscopy read) after continued treatment with XELJANZ 10 mg twice daily for 52 weeks.

14.6 Safety Study in Adults with Rheumatoid Arthritis (XELJANZ Versus TNF-blocker)

A randomized open-label trial (RA Safety Study 1; NCT02092467) was conducted to evaluate safety with XELJANZ tablets (referred to as “XELJANZ” in this subsection of labeling) at two doses, 5 mg twice daily (N=1455) and 10 mg twice daily (N=1456), versus the TNF-blocker control (N=1451) in RA patients 50 years of age and older with at least one cardiovascular risk factor. The co-primary endpoints were adjudicated MACE (defined as cardiovascular death, non-fatal MI, and non-fatal stroke) and adjudicated malignancy (excluding non-melanoma skin cancer). The study was designed to exclude a prespecified risk margin of 1.8 for the hazard ratio of combined XELJANZ regimens versus the TNF-blocker control for each co-primary endpoint. An independent committee conducted a blinded evaluation of the co-primary endpoints according to predefined criteria (adjudication). The study was event-driven and patients were followed until a sufficient number of primary outcome events accrued. Other endpoints included mortality, serious infections, and thromboembolic events. The median on-study follow-up time was 4 years.

The mean age of the population was 61 years (range: 50 to 88 years). Most patients were female (78%) and Caucasian (77%). Patients had a diagnosis of RA for a mean of 10 years, and a median swollen and tender joint count of 11 and 15 respectively. Cardiovascular risk factors included cigarette smoking (current or past) (48%), hypertension (66%), high density lipoprotein <40 mg/dL (12%), diabetes mellitus (17%), family history of premature coronary heart disease (15%), extra-articular disease associated with RA (37%), and history of coronary artery disease (11%).

The non-inferiority criterion was not met for the primary comparison of the combined XELJANZ dosages to TNF blockers since the upper limit of the 95% CI exceeded the pre-specified non-inferiority criterion of 1.8 (for MACE, the upper limit of the 95% CI was 1.94; for malignancies excluding NMSC, the upper limit of the 95% CI was 2.09).

Table 22 shows the study results for each of the co-primary endpoints, and other endpoints. There was an increased risk of death, MACE, malignancies, serious infections, and thromboembolic events associated with both dosages of XELJANZ.

Table 22: Results of RA Safety Study 1 in Adults with Rheumatoid Arthritis 50 years of Age and Older with at Least One Cardiovascular Risk Factor
Endpoint | TNF Blocker N=1451 PY=5468 | XELJANZ 5 mg Twice Daily N=1455 PY=5490 | XELJANZ 10 mg Twice Daily N=1456 PY=5298
MACE, n [IR] | 43 [0.79] | 50 [0.91] | 59 [1.11]
HR (95% CI) [HR (95%) CI for XELJANZ vs. TNF Blocker (Univariate Cox Proportional Hazard Model).] |  | 1.16 (0.77, 1.74) | 1.41 (0.95, 2.10)
MI, [MI and Stroke include fatal and non-fatal events.] n [IR] | 11 [0.20] | 20 [0.36] | 21 [0.39]
HR (95% CI) |  | 1.81 (0.87, 3.79) | 1.97 (0.95, 4.09)
Stroke, n [IR] | 20 [0.36] | 18 [0.33] | 21 [0.39]
HR (95% CI) |  | 0.89 (0.47, 1.69) | 1.08 (0.59, 2.00)
Cardiovascular Death, n [IR] | 15 [0.27] | 18 [0.32] | 25 [0.47]
HR (95% CI) |  | 1.20 (0.60, 2.37) | 1.71 (0.90, 3.24)
Malignancies Excl. NMSC, n [IR] | 42 [0.77] | 62 [1.13] | 60 [1.13]
HR (95% CI) |  | 1.47 (1.00, 2.18) | 1.48 (1.00, 2.19)
Malignancies Excl. NMSC (among current and past smokers) [Data and analyses for Malignancies excluding NMSC for current and ex-smokers are included. There were 720 current and ex-smokers randomized to XELJANZ 5 mg, 704 to XELJANZ 10 mg, and 679 to TNF blockers.] | 25 [0.99] | 41 [1.53] | 48 [1.91]
HR (95% CI) |  | 1.55 (0.94, 2.55) | 1.94 (1.19, 3.14)
All Death | 38 [0.69] | 49 [0.88] | 66 [1.23]
HR (95% CI) |  | 1.29 (0.84, 1.96) | 1.79 (1.20, 2.66)
Serious Infections | 133 [2.52] | 155 [2.95] | 184 [3.65]
HR (95% CI) |  | 1.17 (0.93, 1.47) | 1.44 (1.15, 1.80)
DVT | 9 [0.16] | 12 [0.22] | 15 [0.28]
HR (95% CI) |  | 1.33 (0.56, 3.15) | 1.72 (0.75, 3.92)
PE | 3 [0.05] | 10 [0.18] | 26 [0.49]
HR (95% CI) |  | 3.32 (0.91, 12.08) | 8.95 (2.71, 29.56)
VTE | 12 [0.22] | 18 [0.33] | 36 [0.68]
HR (95% CI) |  | 1.50 (0.72, 3.10) | 3.10 (1.61, 5.96)
ATE | 45 [0.83] | 51 [0.93] | 55 [1.04]
HR (95% CI) |  | 1.13 (0.76, 1.69) | 1.26 (0.85, 1.87)
TE | 56 [1.03] | 67 [1.23] | 86 [1.65]
HR (95% CI) |  | 1.19 (0.84, 1.70) | 1.60 (1.14, 2.23)
Note: XELJANZ 10 mg twice daily was discontinued by the Data Monitoring Committee due to safety concerns, and ongoing patients switched from XELJANZ 10 mg to XELJANZ 5 mg. The column “XELJANZ 10 mg Twice Daily” includes all events and follow-up for patients randomized to XELJANZ 10 mg twice daily. A XELJANZ (refers to tablets and oral solution) 10 mg twice daily (or a XELJANZ XR 22 mg once daily) dosage is not recommended for the treatment of RA, PsA, AS, or pcJIA [see Dosage and Administration (2.3)].
N indicates number of patients; n indicates number of patients with events.
IR indicates incidence rate per 100 person-year (PY).
NMSC: Non-melanoma Skin Cancer; MACE: Major Adverse Cardiac Events; HR: Hazard Ratio; DVT: Deep Vein Thrombosis; PE: Pulmonary Embolism; VTE: Venous Thromboembolism, first occurrence of a VTE, defined as the composite of adjudicated DVT and adjudicated PE; ATE: Arterial Thromboembolism; TE: Thromboembolism, first occurrence of a TE, defined as the composite of adjudicated VTE and unadjudicated ATE.

Lymphomas and lung cancers, which are a subset of all malignancies in RA Safety Study 1, were observed at a higher rate in patients treated with XELJANZ 5 mg twice a day and XELJANZ 10 mg twice a day compared to those treated with TNF blockers. Lymphoma was reported for 4 patients who received XELJANZ 5 mg twice a day, 6 patients who received XELJANZ 10 mg twice a day, and 1 patient who received TNF blockers (Incidence Rate [IR] of 0.07, 0.11, and 0.02 per 100 patient-years, respectively). Among current and past smokers, lung cancer was reported for 13 patients who received XELJANZ 5 mg twice a day, 15 patients who received XELJANZ 10 mg twice a day, and 7 patients who received TNF blockers (IR of 0.48, 0.59, and 0.27 per 100 patient-years, respectively).

Given these increased risks, XELJANZ (tablets and oral solution) 10 mg twice daily (or XELJANZ XR (extended-release tablets) 22 mg once daily) dosages are not recommended for the treatment of RA, PsA, AS or pcJIA [see Dosage and Administration (2.3, 2.4)].

16 HOW SUPPLIED/STORAGE AND HANDLING

How Supplied Information for XELJANZ Tablets and XELJANZ XR

How supplied information for XELJANZ tablets and XELJANZ XR (extended-release tablets) is shown in Table 23.

Table 23: How Supplied Information for XELJANZ Tablets and XELJANZ XR
Dosage Form, Strength, and Description | Bottle Size (number of tablets) | NDC Number
XELJANZ (tofacitinib) tablets, 5 mg White, round, immediate-release film-coated tablets, debossed with “Pfizer” on one side, and “JKI 5” on the other side | 60 | NDC 0069-1001-01
XELJANZ (tofacitinib) tablets, 10 mg Blue, round, immediate-release film-coated tablets, debossed with “Pfizer” on one side, and “JKI 10” on the other side | 60 | NDC 0069-1002-01
XELJANZ XR (tofacitinib) extended-release tablets, 11 mg Pink, oval, extended-release film-coated tablets with a drilled hole at one end of the tablet band and “JKI 11” printed on one side of the tablet | 30 | NDC 0069-0501-30
XELJANZ XR (tofacitinib) extended-release tablets, 22 mg Beige, oval, extended-release film-coated tablets with a drilled hole at one end of the tablet band and “JKI 22” printed on one side of the tablet | 30 | NDC 0069-0502-30

How Supplied Information for XELJANZ Oral Solution

XELJANZ (tofacitinib) oral solution, 1 mg/mL is supplied in bottles (240 mL fill volume) (NDC 0069-1029-02) and is a clear, colorless solution that contains 1 mg of tofacitinib. Each high-density polyethylene (HDPE) bottle contains one press-in bottle adapter and one 5 mL oral dosing syringe with 3.2 mL, 4 mL, and 5 mL gradations. The press-in bottle adapter and oral dosing syringe are not made with natural rubber latex.

Storage and Handling for XELJANZ Tablets/XELJANZ XR

Store XELJANZ tablets and XELJANZ XR at 20°C to 25°C (68°F to 77°F). [See USP Controlled Room Temperature].

Do not repackage.

Storage and Handling for XELJANZ Oral Solution

Store at 20°C to 25°C (68°F to 77°F), excursions permitted between 15°C and 30°C (between 59°F and 86°F). [See USP Controlled Room Temperature].

Store in the original bottle and carton to protect from light.

Use contents of bottle within 60 days of opening.

Discard unused oral solution after 60 days.

17 PATIENT COUNSELING INFORMATION

Advise patients to read the FDA-approved patient labeling (Medication Guide and Instructions for Use).

Serious Infections

Inform patients that XELJANZ (tablets and oral solution) and XELJANZ XR (extended-release tablets) may lower the ability of their immune system to fight infections. Advise patients not to start taking XELJANZ/XELJANZ XR if they have an active infection. Instruct patients to contact their healthcare provider immediately during treatment if symptoms suggesting infection appear to ensure rapid evaluation and appropriate treatment [see Warnings and Precautions (5.1)].

Advise patients that the risk of herpes zoster, some cases of which can be serious, is increased in patients treated with XELJANZ/XELJANZ XR [see Warnings and Precautions (5.1)].

Malignancies and Lymphoproliferative Disorders

Inform patients that XELJANZ/XELJANZ XR may increase their risk of certain cancers, and that lymphoma and other cancers have been observed in patients taking XELJANZ. Instruct patients to inform their healthcare provider if they have ever had any type of cancer [see Warnings and Precautions (5.3)].

Major Adverse Cardiovascular Events

Inform patients that XELJANZ/XELJANZ XR may increase their risk of major adverse cardiovascular events (MACE) defined as myocardial infarction, stroke, and cardiovascular death. Instruct all patients, especially current or past smokers or patients with other cardiovascular risk factors, to be alert for the development of signs and symptoms of cardiovascular events [see Warnings and Precautions (5.4)].

Thrombosis

Advise patients to stop taking XELJANZ/XELJANZ XR and to call their healthcare provider right away if they experience any symptoms of thrombosis (sudden shortness of breath, chest pain worsened with breathing, swelling of leg or arm, leg pain or tenderness, red or discolored skin in the affected leg or arm) [see Warnings and Precautions (5.5)].

Hypersensitivity

Advise patients to stop taking XELJANZ/XELJANZ XR and to call their healthcare provider right away if they experience any symptoms of allergic reactions while taking XELJANZ/XELJANZ XR [see Warnings and Precautions (5.7)].

Important Information on Laboratory Abnormalities

Inform patients that XELJANZ/XELJANZ XR may affect certain lab test results, and that blood tests are required before and during XELJANZ/XELJANZ XR treatment [see Warnings and Precautions (5.8)].

Pregnancy

Advise pregnant females and females of reproductive potential of the potential risk to a fetus. Advise females to inform their prescriber of a known or suspected pregnancy [see Use in Specific Populations (8.1)].

Lactation

Advise women not to breastfeed during treatment with XELJANZ/XELJANZ XR and for at least 18 hours after the last dose of XELJANZ or 36 hours after the last dose of XELJANZ XR [see Use in Specific Populations (8.2)].

Infertility

Advise females of reproductive potential that XELJANZ/XELJANZ XR may impair fertility [see Use in Specific Populations (8.3), Nonclinical Toxicology (13.1)]. It is not known if this effect is reversible.

Residual Tablet Shell

Patients receiving XELJANZ XR may notice an inert tablet shell passing in the stool or via colostomy. Patients should be informed that the active medication has already been absorbed by the time the patient sees the inert tablet shell.

This product’s labeling may have been updated. For the most recent prescribing information, please visit www.pfizer.com.

LAB-0445-29.0

MEDICATION GUIDE

XELJANZ (ZEL' JANS')
(tofacitinib)
tablets, for oral use

XELJANZ XR (ZEL' JANS' EKS-AHR)
(tofacitinib) extended-release tablets for oral use

XELJANZ (ZEL' JANS')
(tofacitinib)
oral solution

What is the most important information I should know about XELJANZ/XELJANZ XR/XELJANZ oral solution?
XELJANZ/XELJANZ XR/XELJANZ oral solution may cause serious side effects including:

1.

Serious infections. XELJANZ/XELJANZ XR/XELJANZ oral solution are medicines that affect your immune system. XELJANZ/XELJANZ XR/XELJANZ oral solution can lower the ability of your immune system to fight infections. Some people can have serious infections while taking XELJANZ/XELJANZ XR/XELJANZ oral solution, including tuberculosis (TB), and infections caused by bacteria, fungi, or viruses that can spread throughout the body. Some people have died from these infections.

- Your healthcare provider should test you for TB before starting XELJANZ/XELJANZ XR/XELJANZ oral solution and during treatment.
- Your healthcare provider should monitor you closely for signs and symptoms of TB infection during treatment with XELJANZ/XELJANZ XR/XELJANZ oral solution.

You should not start taking XELJANZ/XELJANZ XR/XELJANZ oral solution if you have any kind of infection unless your healthcare provider tells you it is okay. You may be at a higher risk of developing shingles (herpes zoster).
People with ulcerative colitis taking the higher dose of XELJANZ (10 mg twice daily) or XELJANZ XR (22 mg one time each day) have a higher risk of serious infections and shingles.
Before starting XELJANZ/XELJANZ XR/XELJANZ oral solution, tell your healthcare provider if you:

- think you have an infection or have symptoms of an infection such as:

  - fever, sweating, or chills
  - cough
  - blood in phlegm
  - warm, red, or painful skin or sores on your body
  - burning when you urinate or urinating more often than normal

  - muscle aches
  - shortness of breath
  - weight loss
  - diarrhea or stomach pain
  - feeling very tired

- are being treated for an infection.
- get a lot of infections or have infections that keep coming back.
- have diabetes, chronic lung disease, HIV, or a weak immune system. People with these conditions have a higher chance for infections.
- have TB, or have been in close contact with someone with TB.
- live or have lived, or have traveled to certain parts of the country (such as the Ohio and Mississippi River valleys and the Southwest) where there is an increased chance for getting certain kinds of fungal infections (histoplasmosis, coccidioidomycosis, or blastomycosis). These infections may happen or become more severe if you take XELJANZ/XELJANZ XR/XELJANZ oral solution. Ask your healthcare provider if you do not know if you have lived in an area where these infections are common.
- have or have had hepatitis B or C.

After starting XELJANZ/XELJANZ XR/XELJANZ oral solution, call your healthcare provider right away if you have any symptoms of an infection. XELJANZ/XELJANZ XR/XELJANZ oral solution can make you more likely to get infections or make worse any infection that you have.

2.

Increased risk of death in people 50 years of age and older who have at least 1 heart disease (cardiovascular) risk factor and are taking XELJANZ 5 mg or 10 mg twice daily.

3.

Cancer and immune system problems. XELJANZ/XELJANZ XR/XELJANZ oral solution may increase your risk of certain cancers by changing the way your immune system works.

- Lymphoma and other cancers including skin cancers can happen in people taking XELJANZ/XELJANZ XR/XELJANZ oral solution. People taking XELJANZ 5 mg twice daily or XELJANZ 10 mg twice daily have a higher risk of certain cancers including lymphoma and lung cancer, especially if you are a current or past smoker. People with ulcerative colitis taking the higher dose of XELJANZ (10 mg twice daily) or XELJANZ XR (22 mg one time each day) have a higher risk of skin cancers. Tell your healthcare provider if you have ever had any type of cancer.

4.

Increased risk of major cardiovascular events such as heart attack, stroke or death in people 50 years of age and older who have at least 1 heart disease (cardiovascular) risk factor and are taking XELJANZ 5 mg or 10 mg twice daily, especially if you are a current or past smoker.
Get emergency help right away if you have any symptoms of a heart attack or stroke while taking XELJANZ/XELJANZ XR/XELJANZ oral solution, including:

- discomfort in the center of your chest that lasts for more than a few minutes, or that goes away and comes back
- severe tightness, pain, pressure, or heaviness in your chest, throat, neck, or jaw
- pain or discomfort in your arms, back, neck, jaw, or stomach
- shortness of breath with or without chest discomfort
- breaking out in a cold sweat
- nausea or vomiting
- feeling lightheaded
- weakness in one part or on one side of your body
- slurred speech

5.

Blood clots in the lungs, veins of the legs or arms, and arteries. Blood clots in the lungs (pulmonary embolism, PE), veins of the legs (deep vein thrombosis, DVT) and arteries (arterial thrombosis) have happened more often in people who are 50 years of age and older and with at least 1 heart disease (cardiovascular) risk factor taking XELJANZ 5 mg or 10 mg twice daily. Blood clots in the lungs have also happened in people with ulcerative colitis. Some people have died from these blood clots.

- Stop taking XELJANZ/XELJANZ XR/XELJANZ oral solution and tell your healthcare provider right away if you develop signs and symptoms of a blood clot, such as sudden shortness of breath or difficulty breathing, chest pain, swelling of the leg or arm, leg pain or tenderness, or redness or discoloration in the leg or arm.

6.

Tears (perforation) in the stomach or intestines.

- Tell your healthcare provider if you have had diverticulitis (inflammation in parts of the large intestine) or ulcers in your stomach or intestines. Some people taking XELJANZ/XELJANZ XR/XELJANZ oral solution can get tears in their stomach or intestines. This happens most often in people who also take nonsteroidal anti-inflammatory drugs (NSAIDs), corticosteroids, or methotrexate.
  Tell your healthcare provider right away if you have fever and stomach-area pain that does not go away, and a change in your bowel habits.

7.

Allergic reactions.

- Symptoms such as swelling of your lips, tongue, or throat, or hives (raised, red patches of skin that are often very itchy) that may mean you are having an allergic reaction have been seen in people taking XELJANZ/XELJANZ XR. Some of these reactions were serious. If any of these symptoms occur while you are taking XELJANZ/XELJANZ XR/XELJANZ oral solution, stop XELJANZ/XELJANZ XR/XELJANZ oral solution and call your healthcare provider right away.

8.

Changes in certain laboratory test results. Your healthcare provider should do blood tests before you start taking XELJANZ/XELJANZ XR/XELJANZ oral solution and while you take XELJANZ/XELJANZ XR/XELJANZ oral solution to check for the following side effects:

- changes in lymphocyte counts. Lymphocytes are white blood cells that help the body fight off infections.
- low neutrophil counts. Neutrophils are white blood cells that help the body fight off infections.
- low red blood cell count. This may mean that you have anemia, which may make you feel weak and tired.

Your healthcare provider should routinely check certain liver tests.
You should not take XELJANZ/XELJANZ XR/XELJANZ oral solution if your lymphocyte count, neutrophil count, or red blood cell count is too low or your liver tests are too high.
Your healthcare provider may stop your XELJANZ/XELJANZ XR/XELJANZ oral solution treatment for a period of time if needed because of changes in these blood test results.
You may also have changes in other laboratory tests, such as your blood cholesterol levels. Your healthcare provider should do blood tests to check your cholesterol levels 4 to 8 weeks after you start taking XELJANZ/XELJANZ XR/XELJANZ oral solution, and as needed after that. Normal cholesterol levels are important to good heart health.

See "What are the possible side effects of XELJANZ/XELJANZ XR/XELJANZ oral solution?" for more information about side effects.

What is XELJANZ/XELJANZ XR/XELJANZ oral solution?

- XELJANZ/XELJANZ XR/XELJANZ oral solution is a prescription medicine called a Janus kinase (JAK) inhibitor. XELJANZ/XELJANZ XR is used to treat adults with moderately to severely active rheumatoid arthritis when 1 or more medicines called tumor necrosis factor (TNF) blockers have been used and did not work well or cannot be tolerated.
- XELJANZ/XELJANZ XR is used to treat adults and XELJANZ/XELJANZ oral solution is used to treat children 2 years of age and older with active psoriatic arthritis when 1 or more TNF blocker medicines have been used, and did not work well or cannot be tolerated.
- XELJANZ/XELJANZ XR is used to treat adults with active ankylosing spondylitis when 1 or more TNF blocker medicines have been used and did not work well or cannot be tolerated.
- XELJANZ/XELJANZ XR is used to treat adults with moderately to severely active ulcerative colitis when 1 or more TNF blocker medicines have been used, and did not work well or cannot be tolerated.
- XELJANZ/XELJANZ oral solution is used to treat children 2 years of age and older with active polyarticular course juvenile arthritis when 1 or more TNF blocker medicines have been used, and did not work well or cannot be tolerated.

It is not known if XELJANZ/XELJANZ XR/XELJANZ oral solution is safe and effective in people with Hepatitis B or C.
XELJANZ/XELJANZ XR/XELJANZ oral solution is not recommended for people with severe liver problems.
It is not known if XELJANZ/XELJANZ oral solution is safe and effective in children for treatment other than active polyarticular course juvenile arthritis and psoriatic arthritis.
It is not known if XELJANZ XR is safe and effective in children.

What should I tell my healthcare provider before taking XELJANZ/XELJANZ XR/XELJANZ oral solution?
Before taking XELJANZ/XELJANZ XR/XELJANZ oral solution, tell your healthcare provider about all of your medical conditions, including if you:

- have an infection. See "What is the most important information I should know about XELJANZ/XELJANZ XR/XELJANZ oral solution?"
- are a current or past smoker.
- have had any type of cancer.
- have had a heart attack, other heart problems or stroke.
- have had blood clots in the veins of your legs, arms, or lungs, or clots in the arteries in the past.
- have liver problems.
- have kidney problems.
- have any stomach-area (abdominal) pain or been diagnosed with diverticulitis or ulcers in your stomach or intestines.
- have had a reaction to tofacitinib or any of the ingredients in XELJANZ/XELJANZ XR/XELJANZ oral solution.
- have recently received or are scheduled to receive a vaccine. People who take XELJANZ/XELJANZ XR/XELJANZ oral solution should not receive live vaccines. People taking XELJANZ/XELJANZ XR/XELJANZ oral solution can receive non-live vaccines.
- plan to become pregnant or are pregnant. XELJANZ/XELJANZ XR/XELJANZ oral solution may affect the ability of females to get pregnant. It is not known if this will change after stopping XELJANZ/XELJANZ XR/XELJANZ oral solution. It is not known if XELJANZ/XELJANZ XR/XELJANZ oral solution will harm an unborn baby.
- plan to breastfeed or are breastfeeding. You and your healthcare provider should decide if you will take XELJANZ/XELJANZ XR/XELJANZ oral solution or breastfeed. You should not do both. After you stop your treatment with XELJANZ/XELJANZ XR/XELJANZ oral solution do not start breastfeeding again until:
  - 18 hours after your last dose of XELJANZ/XELJANZ oral solution or
  - 36 hours after your last dose of XELJANZ XR

Tell your healthcare provider about all the medicines you take, including prescription and over-the-counter medicines, vitamins, and herbal supplements. XELJANZ/XELJANZ XR/XELJANZ oral solution and other medicines may affect each other causing side effects.
Especially tell your healthcare provider if you take:

- any other medicines to treat your rheumatoid arthritis, psoriatic arthritis, ankylosing spondylitis, ulcerative colitis, or polyarticular course juvenile arthritis. You should not take tocilizumab (Actemra), etanercept (Enbrel), adalimumab (Humira), infliximab (Remicade), rituximab (Rituxan), abatacept (Orencia), anakinra (Kineret), certolizumab (Cimzia), golimumab (Simponi), ustekinumab (Stelara), secukinumab (Cosentyx), vedolizumab (Entyvio), ixekizumab (Taltz), azathioprine, cyclosporine, or other immunosuppressive drugs while you are taking XELJANZ/XELJANZ XR/XELJANZ oral solution. Taking XELJANZ/XELJANZ XR/XELJANZ oral solution with these medicines may increase your risk of infection.
- medicines that affect the way certain liver enzymes work. Ask your healthcare provider if you are not sure if your medicine is one of these.

Know the medicines you take. Keep a list of them to show your healthcare provider and pharmacist when you get a new medicine.

How should I take XELJANZ/XELJANZ XR/XELJANZ oral solution?
Take XELJANZ/XELJANZ XR/XELJANZ oral solution exactly as your healthcare provider tells you to take it.

- Take XELJANZ/XELJANZ oral solution 2 times a day with or without food.
- Take XELJANZ XR 1 time a day with or without food.
- Swallow XELJANZ XR tablets whole and intact. Do not crush, split, or chew.
- When you take XELJANZ XR, you may see something in your stool that looks like a tablet. This is the empty shell from the tablet after the medicine has been absorbed by your body.
- If you take too much XELJANZ/XELJANZ XR/XELJANZ oral solution, call your healthcare provider or go to the nearest hospital emergency room right away.
- For the treatment of psoriatic arthritis, take XELJANZ/XELJANZ XR/XELJANZ oral solution in combination with methotrexate, sulfasalazine or leflunomide as instructed by your healthcare provider.
- XELJANZ XR should not be used instead of XELJANZ oral solution.

What are the possible side effects of XELJANZ/XELJANZ XR/XELJANZ oral solution?

XELJANZ/XELJANZ XR/XELJANZ oral solution may cause serious side effects, including:

- See "What is the most important information I should know about XELJANZ/XELJANZ XR/XELJANZ oral solution?"
- Hepatitis B or C activation infection in people who carry the virus in their blood. If you are a carrier of the hepatitis B or C virus (viruses that affect the liver), the virus may become active while you use XELJANZ/XELJANZ XR/XELJANZ oral solution. Your healthcare provider may do blood tests before you start treatment with XELJANZ/XELJANZ XR/XELJANZ oral solution and while you are taking XELJANZ/XELJANZ XR/XELJANZ oral solution. Tell your healthcare provider if you have any of the following symptoms of a possible hepatitis B or C infection:

  - feel very tired
  - little or no appetite
  - clay-colored bowel movements
  - chills
  - muscle aches
  - skin rash

  - skin or eyes look yellow
  - vomiting
  - fevers
  - stomach discomfort
  - dark urine

Common side effects of XELJANZ/XELJANZ XR/XELJANZ oral solution in people with rheumatoid arthritis, psoriatic arthritis, and ankylosing spondylitis include:

- upper respiratory tract infections (common cold, sinus infections)
- headache
- diarrhea
- nasal congestion, sore throat, and runny nose (nasopharyngitis)
- high blood pressure (hypertension)
- acne

Common side effects of XELJANZ/XELJANZ XR in people with ulcerative colitis include:

- nasal congestion, sore throat, and runny nose (nasopharyngitis)
- increased cholesterol levels
- headache
- upper respiratory tract infections (common cold, sinus infections)
- increased muscle enzyme levels
- rash
- acne
- diarrhea
- shingles (herpes zoster)

Common side effects of XELJANZ/XELJANZ oral solution in children with polyarticular course juvenile arthritis and psoriatic arthritis include:

- upper respiratory tract infections (common cold, sinus infections)
- nasal congestion, sore throat, and runny nose (nasopharyngitis)
- headache
- fever
- nausea
- vomiting
- acne

Tell your healthcare provider if you have any side effect that bothers you or that does not go away.
These are not all the possible side effects of XELJANZ/XELJANZ XR/XELJANZ oral solution. For more information, ask your healthcare provider or pharmacist.
Call your doctor for medical advice about side effects. You may report side effects to FDA at 1-800-FDA-1088.
You may also report side effects to Pfizer at 1-800-438-1985.

How should I store XELJANZ/XELJANZ XR/XELJANZ oral solution?

- Store XELJANZ/XELJANZ XR at room temperature between 68°F to 77°F (20°C to 25°C).
- Store XELJANZ oral solution at room temperature between 68°F to 77°F (20°C to 25°C) in the original bottle and carton to protect from light.
- Safely throw away XELJANZ oral solution that is out of date or no longer needed. Use XELJANZ oral solution within 60 days of opening the bottle. Throw away (discard) remaining oral solution after 60 days.

Keep XELJANZ/XELJANZ XR/XELJANZ oral solution and all medicines out of the reach of children.

General information about the safe and effective use of XELJANZ/XELJANZ XR/XELJANZ oral solution.
Medicines are sometimes prescribed for purposes other than those listed in a Medication Guide. Do not use XELJANZ/XELJANZ XR/XELJANZ oral solution for a condition for which it was not prescribed. Do not give XELJANZ/XELJANZ XR/XELJANZ oral solution to other people, even if they have the same symptoms you have. It may harm them.
This Medication Guide summarizes the most important information about XELJANZ/XELJANZ XR/XELJANZ oral solution. If you would like more information, talk to your healthcare provider. You can ask your pharmacist or healthcare provider for information about XELJANZ/XELJANZ XR/XELJANZ oral solution that is written for health professionals.

What are the ingredients in XELJANZ 5 mg?
Active ingredient: tofacitinib citrate
Inactive ingredients: croscarmellose sodium, HPMC 2910/Hypromellose 6cP, lactose monohydrate, macrogol/PEG3350, magnesium stearate, microcrystalline cellulose, titanium dioxide, and triacetin.
What are the ingredients in XELJANZ 10 mg?
Active ingredient: tofacitinib citrate
Inactive ingredients: croscarmellose sodium, FD&C Blue #1/Brilliant Blue FCF Aluminum Lake, FD&C Blue #2/Indigo Carmine Aluminum Lake, HPMC 2910/Hypromellose 6cP, lactose monohydrate, macrogol/PEG3350, magnesium stearate, microcrystalline cellulose, titanium dioxide, and triacetin.
What are the ingredients in XELJANZ XR 11 mg?
Active ingredient: tofacitinib citrate
Inactive ingredients: cellulose acetate, copovidone, hydroxyethyl cellulose, hydroxypropyl cellulose, HPMC 2910/Hypromellose, magnesium stearate, red iron oxide, sorbitol, titanium dioxide, and triacetin. Printing ink contains ammonium hydroxide, ferrosoferric oxide/black iron, propylene glycol, and shellac glaze.
What are the ingredients in XELJANZ XR 22 mg?
Active ingredient: tofacitinib citrate
Inactive ingredients: cellulose acetate, copovidone, FD&C Blue #2 Aluminum Lake, hydroxyethyl cellulose, hydroxypropyl cellulose, HPMC 2910/Hypromellose, magnesium stearate, red iron oxide, sorbitol, titanium dioxide, triacetin, and yellow iron oxide. Printing ink contains ammonium hydroxide, ferrosoferric oxide/black iron oxide, propylene glycol, and shellac glaze.
What are the ingredients in XELJANZ oral solution?
Active ingredient: tofacitinib citrate
Inactive ingredients: grape flavor (natural), hydrochloric acid, lactic acid, purified water, sodium benzoate, sucralose, and xylitol.

This Medication Guide may have been updated. For the most recent Medication Guide, please visit www.pfizer.com.

LAB-0535-16.0

This Medication Guide has been approved by the U.S. Food and Drug Administration. Revised: October 2025

INSTRUCTIONS FOR USE

XELJANZ® (ZEL' JANS')
(tofacitinib)
oral solution

Read this Instructions for Use before you start taking XELJANZ oral solution and each time you get a refill. There may be new information. This leaflet does not take the place of talking to your healthcare provider about your medical condition or treatment.

Important information about measuring XELJANZ oral solution:

Always use the oral dosing syringe that comes with XELJANZ oral solution to measure and take your prescribed dose. Ask your healthcare provider or pharmacist to show you how to measure your prescribed dose if you are not sure.

How should I store XELJANZ?

- Store XELJANZ oral solution at room temperature between 68°F to 77°F (20°C to 25°C).
- Always store XELJANZ oral solution in the original bottle and carton to protect from light.

Keep XELJANZ and all medicines out of the reach of children.

Use XELJANZ oral solution within 60 days of opening the bottle. Throw away (discard) remaining XELJANZ oral solution after 60 days.

To help you remember when to throw away your bottle of XELJANZ oral solution, you can write the date when you first start to use it on the carton and below:

Date of first use ____ / ____ / ____.

Before each use:

Wash your hands with soap and water and place the items from the carton on a clean, flat surface.

Each carton of XELJANZ oral solution contains:

- 1 press-in bottle adapter
- 1 bottle of XELJANZ oral solution
- 1 oral dosing syringe

Step 1. Remove bottle from carton

Open the carton and remove the bottle of XELJANZ oral solution.

Step 2. Open bottle

Open the bottle by pushing down on the child-resistant cap and turning it to the left (counter-clockwise) as shown. Remove the seal off the top of the bottle (first time only).

Do not throw away the child-resistant cap.

Note: The bottle does not need to be shaken before use.

Step 3. Insert press-in bottle adapter (first time only)

Remove the press-in bottle adapter and oral dosing syringe from the plastic overwrap. With the bottle on a flat surface, push the ribbed end of the press-in bottle adapter all the way into the neck of the bottle with your thumbs while holding the bottle firmly.

Note: Do not remove the press-in bottle adapter from the bottle after it is inserted.

Step 4. Remove air from oral dosing syringe

Push the oral dosing syringe plunger all the way down to the tip of the syringe barrel to remove excess air.

Step 5. Insert the oral dosing syringe

Insert the oral dosing syringe tip into the upright bottle through the opening of the press-in bottle adapter until it is firmly in place.

Step 6. Withdraw dose from bottle

With the oral dosing syringe in place, turn the bottle upside down. Pull down on the plunger until the bottom of the plunger is even with the markings on the oral dosing syringe for your prescribed dose of oral solution.

If you see air bubbles in the oral dosing syringe, fully push the plunger in so that the oral solution flows back into the bottle. Then withdraw your prescribed dose of oral solution.

Step 7. Remove oral dosing syringe

Turn the bottle upright and place the bottle on a flat surface. Remove the oral dosing syringe from the press-in bottle adapter and bottle by pulling straight up on the oral dosing syringe barrel.

Step 8. Check the dose

Check that the correct dose was drawn up into the oral dosing syringe.

If the dose is not correct, insert the oral dosing syringe tip firmly into the press-in bottle adapter. Fully push in the plunger so that the oral solution flows back into the bottle. Repeat Step 6 and Step 7.

Step 9. Take the dose of XELJANZ

Place the tip of the oral dosing syringe into the inside of the cheek.

Slowly push the plunger all the way down to give all of the medicine in the oral dosing syringe. Make sure there is time to swallow the medicine.

Step 10. Close the bottle

Close the bottle tightly by turning the child-resistant cap to the right (clockwise), leaving the press-in bottle adapter in place.

Place the bottle back into the carton.

Close the carton to protect XELJANZ oral solution from light.

Step 11. Clean oral dosing syringe

Remove the plunger from the barrel by pulling the plunger and the barrel away from each other.

Rinse both with water after each use.

Allow to air dry. When the barrel and plunger are dry, put the oral dosing syringe back together by inserting the plunger into the barrel.

Store the oral dosing syringe with the XELJANZ oral solution.

Do not throw away the oral dosing syringe.

LAB-1422-3.0

This Instructions for Use has been approved by the U.S. Food and Drug Administration.
Approved: October 2025

This Instructions for Use may have been updated. For the most recent Instructions for Use, please visit www.pfizer.com.

PRINCIPAL DISPLAY PANEL - 5 mg Tablet Bottle Label

PROFESSIONAL SAMPLE-NOT FOR SALE
ALWAYS DISPENSE WITH MEDICATION GUIDE

NDC 63539-012-02

Pfizer

Xeljanz™
(tofacitinib tablets)

5 mg*

60 Tablets
Rx only

PRINCIPAL DISPLAY PANEL - 11 mg Tablet Bottle Label

PROFESSIONAL SAMPLE-NOT FOR SALE
ALWAYS DISPENSE WITH MEDICATION GUIDE

NDC 63539-501-30

Pfizer

Xeljanz® XR
(tofacitinib) tablets

Extended Release Tablets

11 mg*

30 Tablets
Rx only

PRINCIPAL DISPLAY PANEL - 10 mg Tablet Bottle Label

PROFESSIONAL SAMPLE – NOT FOR SALE
ALWAYS DISPENSE WITH MEDICATION GUIDE

NDC 63539-016-02

Pfizer

Xeljanz®
(tofacitinib) tablets

10 mg*

10mg Is Recommended Only In
Ulcerative Colitis

60 Tablets
Rx only

PRINCIPAL DISPLAY PANEL - 22 mg Tablet Bottle Label

PROFESSIONAL SAMPLE-NOT FOR SALE
ALWAYS DISPENSE WITH MEDICATION GUIDE

Pfizer

NDC 63539-502-30

Xeljanz® XR
(tofacitinib) tablets

Extended Release Tablets

22 mg*

22mg Is Recommended Only In
Ulcerative Colitis

30 Tablets
Rx only

PRINCIPAL DISPLAY PANEL - 240 mL Bottle Label

PROFESSIONAL SAMPLE – NOT FOR SALE

NDC 63539-029-01

ALWAYS DISPENSE WITH
MEDICATION GUIDE

Pfizer

Xeljanz®
(tofacitinib) oral solution

1 mg/mL

240 mL
Rx only

PRINCIPAL DISPLAY PANEL - 240 mL Bottle Carton

PROFESSIONAL SAMPLE – NOT FOR SALE

NDC 63539-029-02

ALWAYS DISPENSE WITH MEDICATION GUIDE

Pfizer

Xeljanz®
(tofacitinib) oral solution

1 mg/mL

Contents:

- Oral solution bottle
- 1 Oral dosing syringe
- 1 Press-in bottle adapter
- Prescribing Information
- Medication Guide
- Instructions for Use

240 mL
Rx only